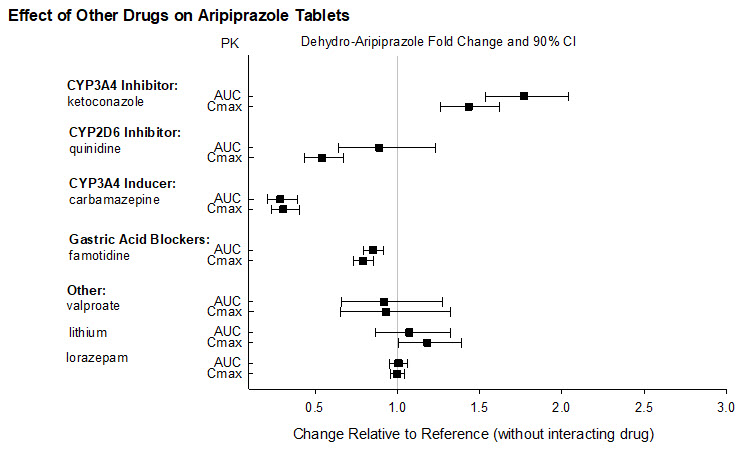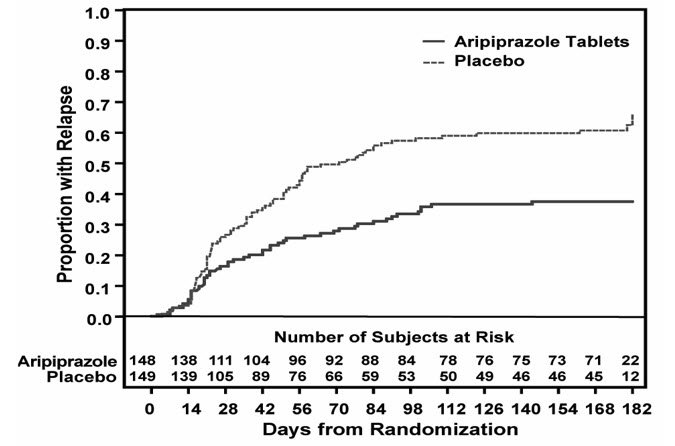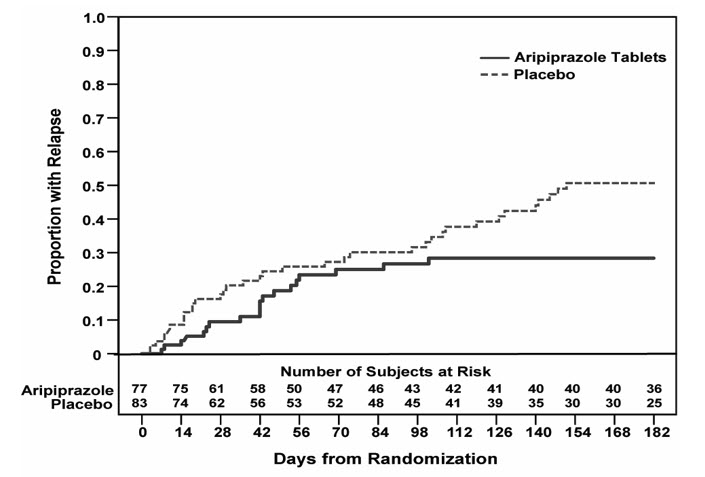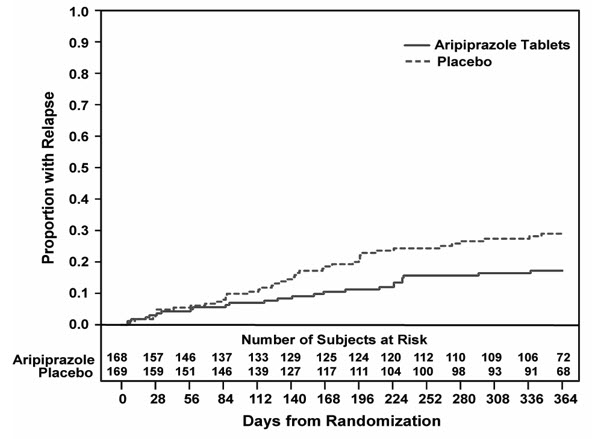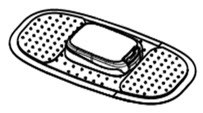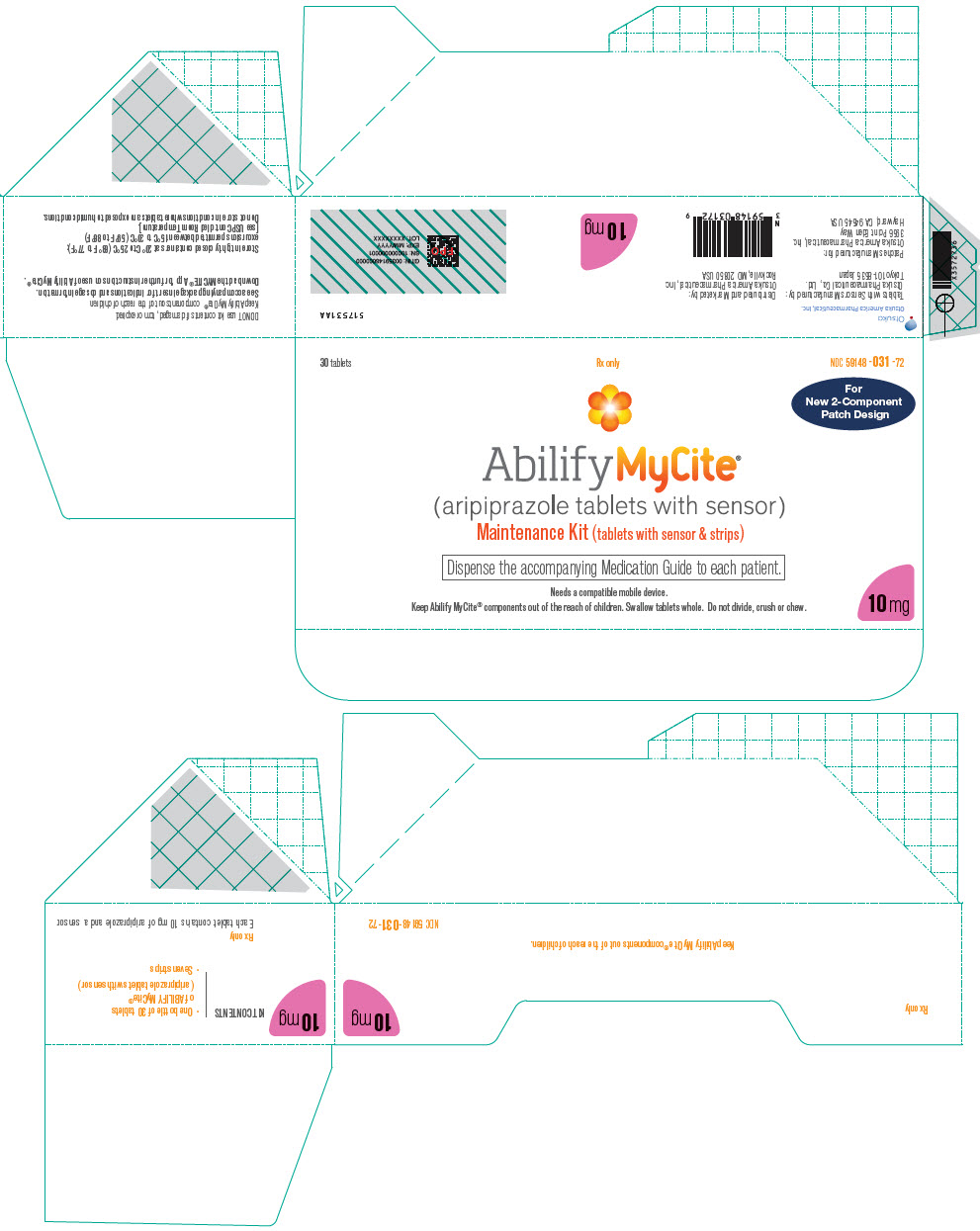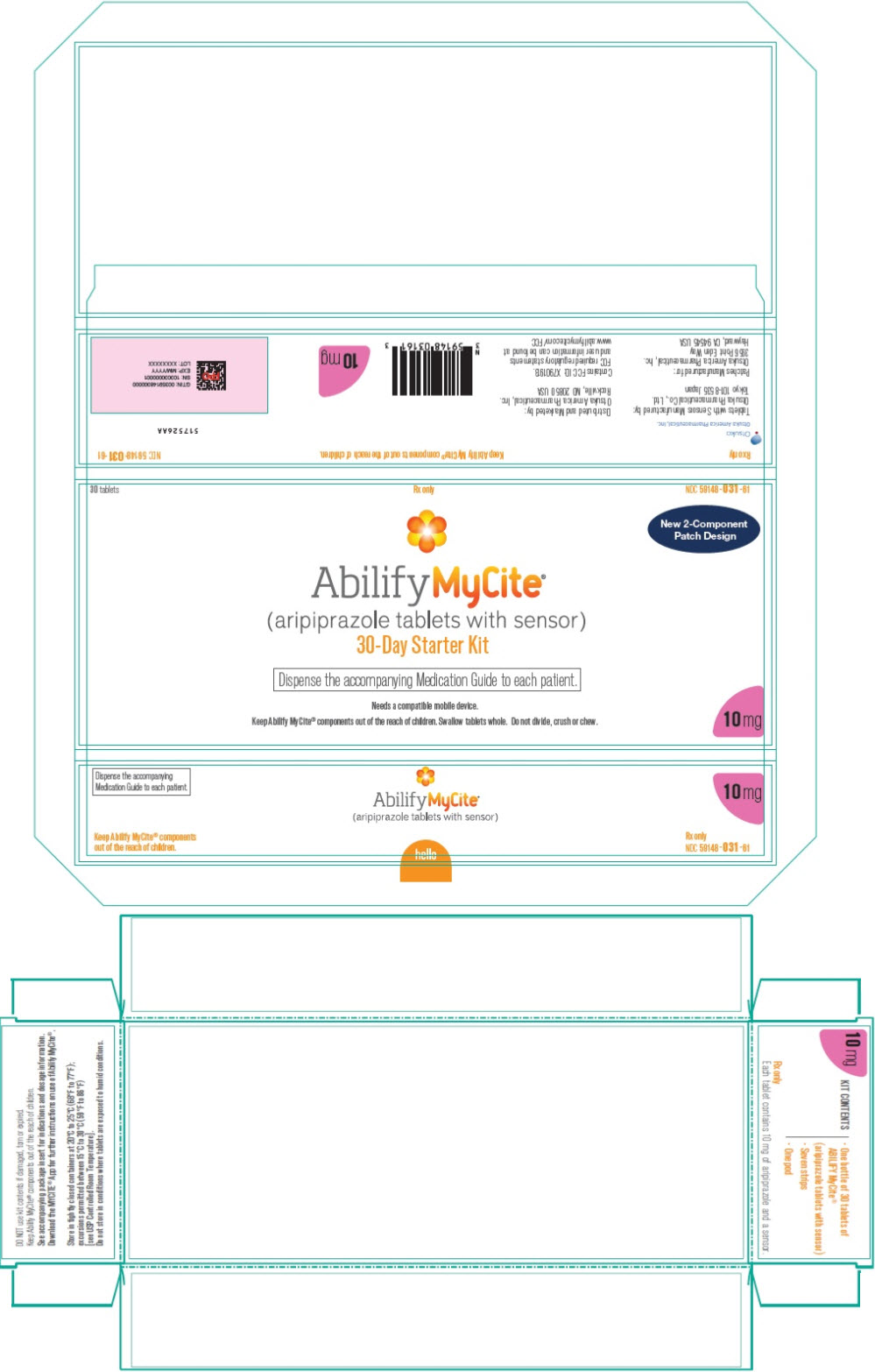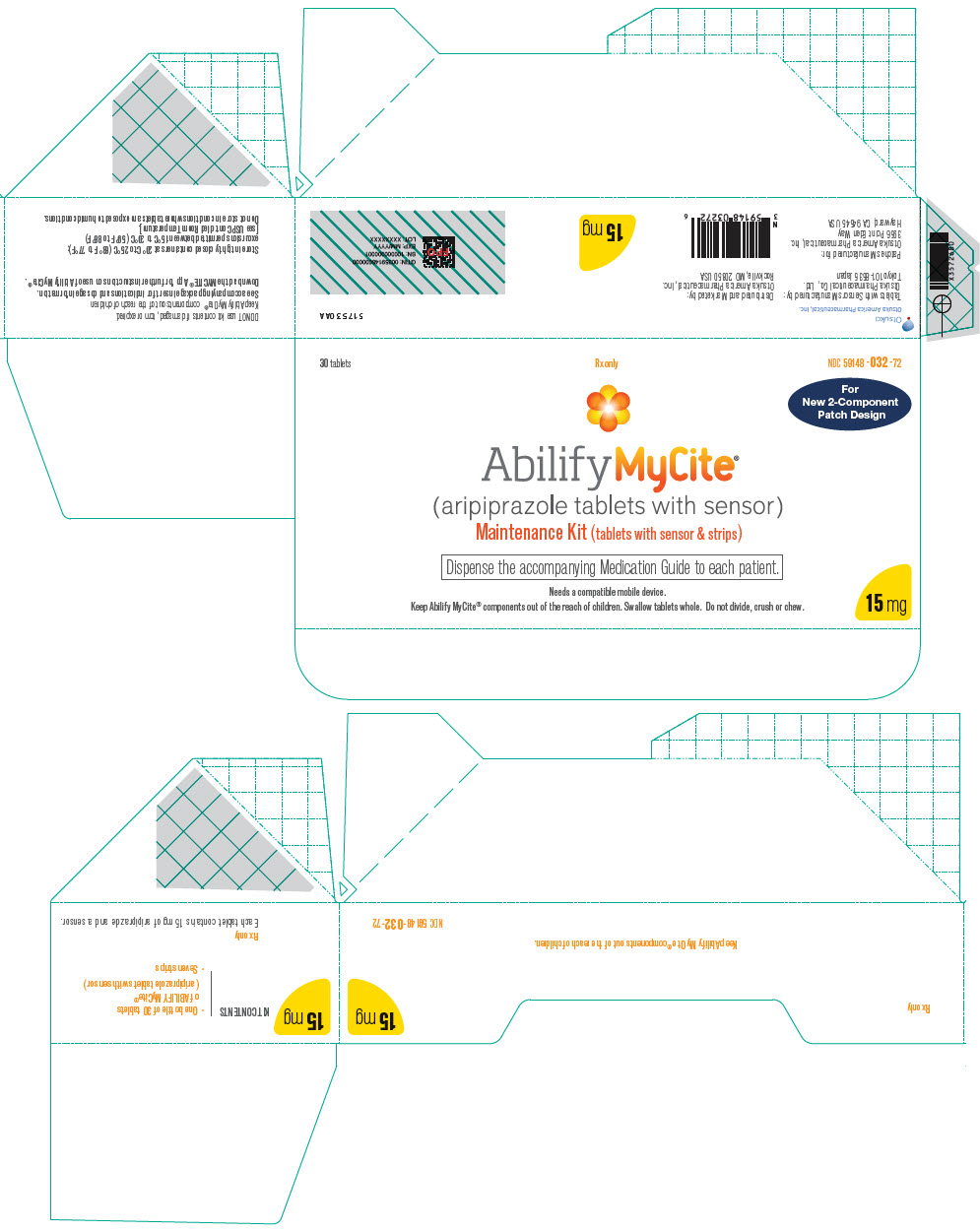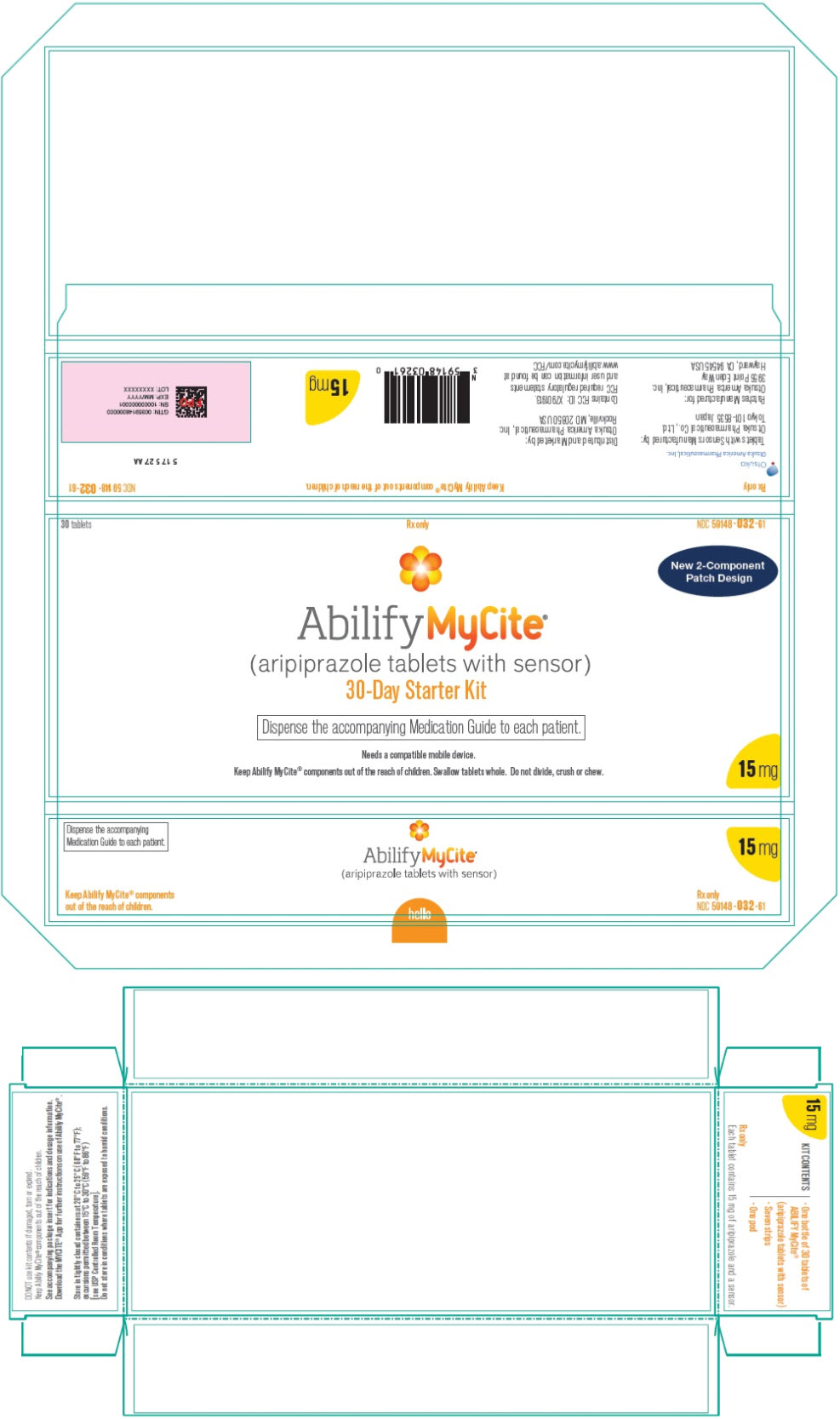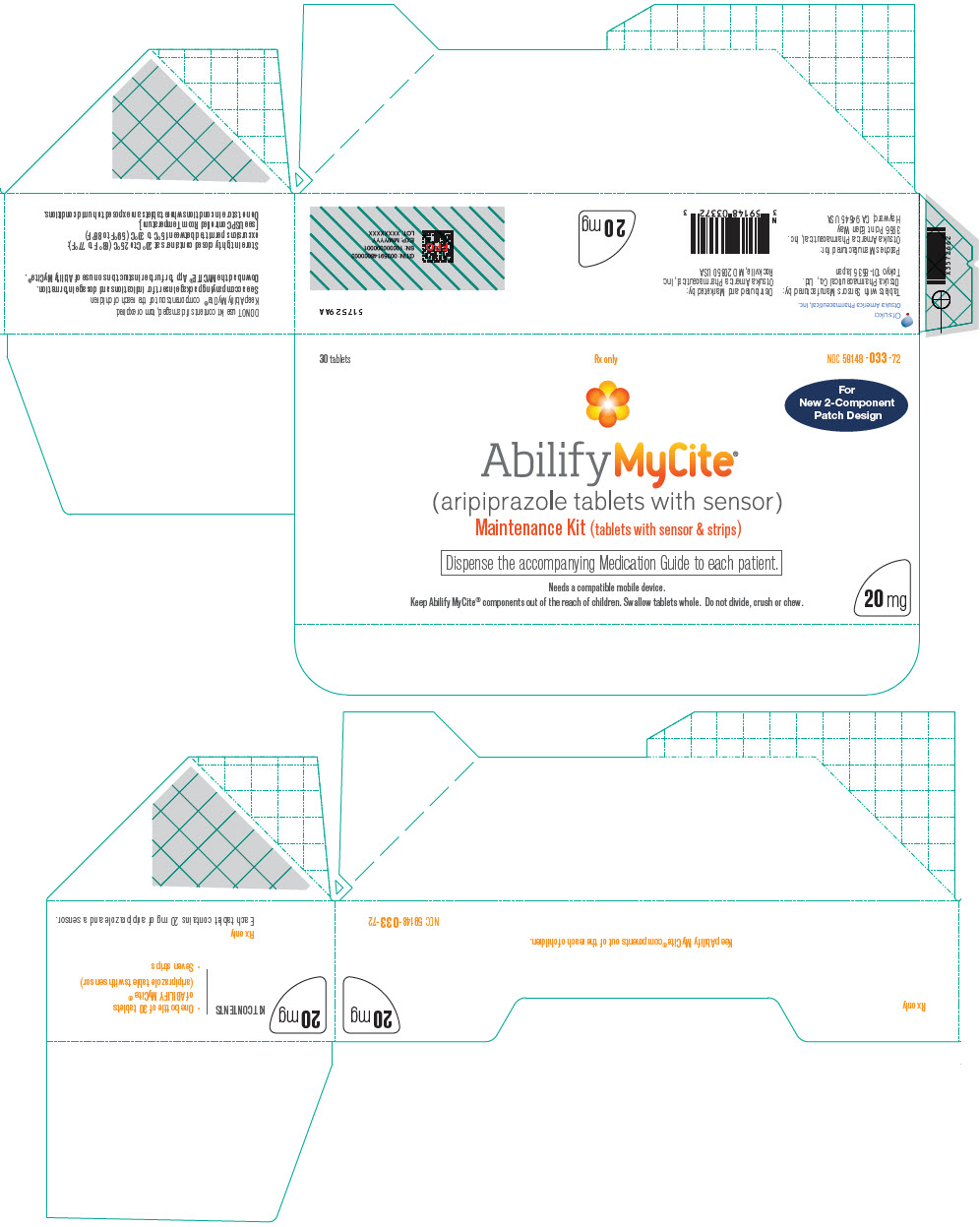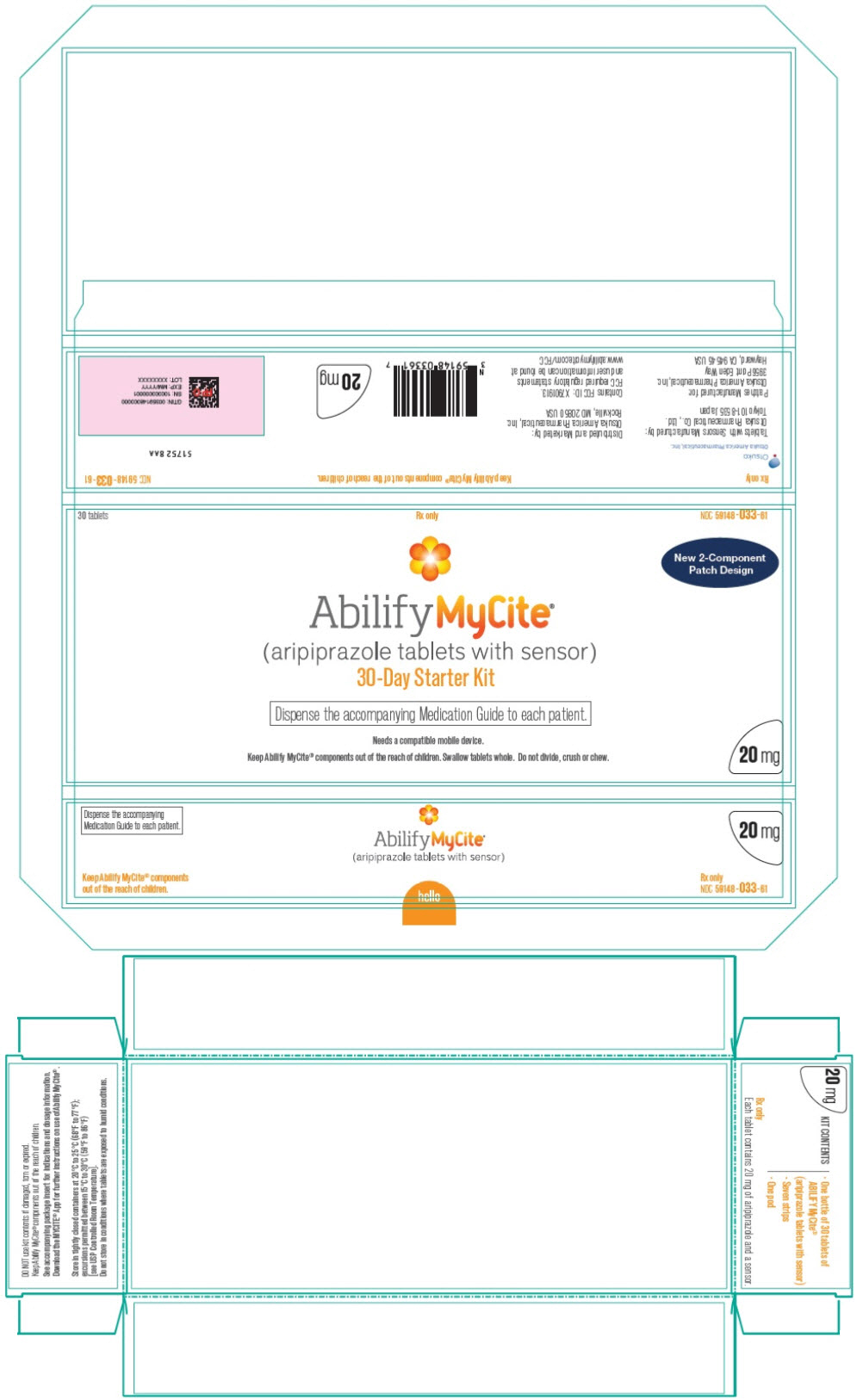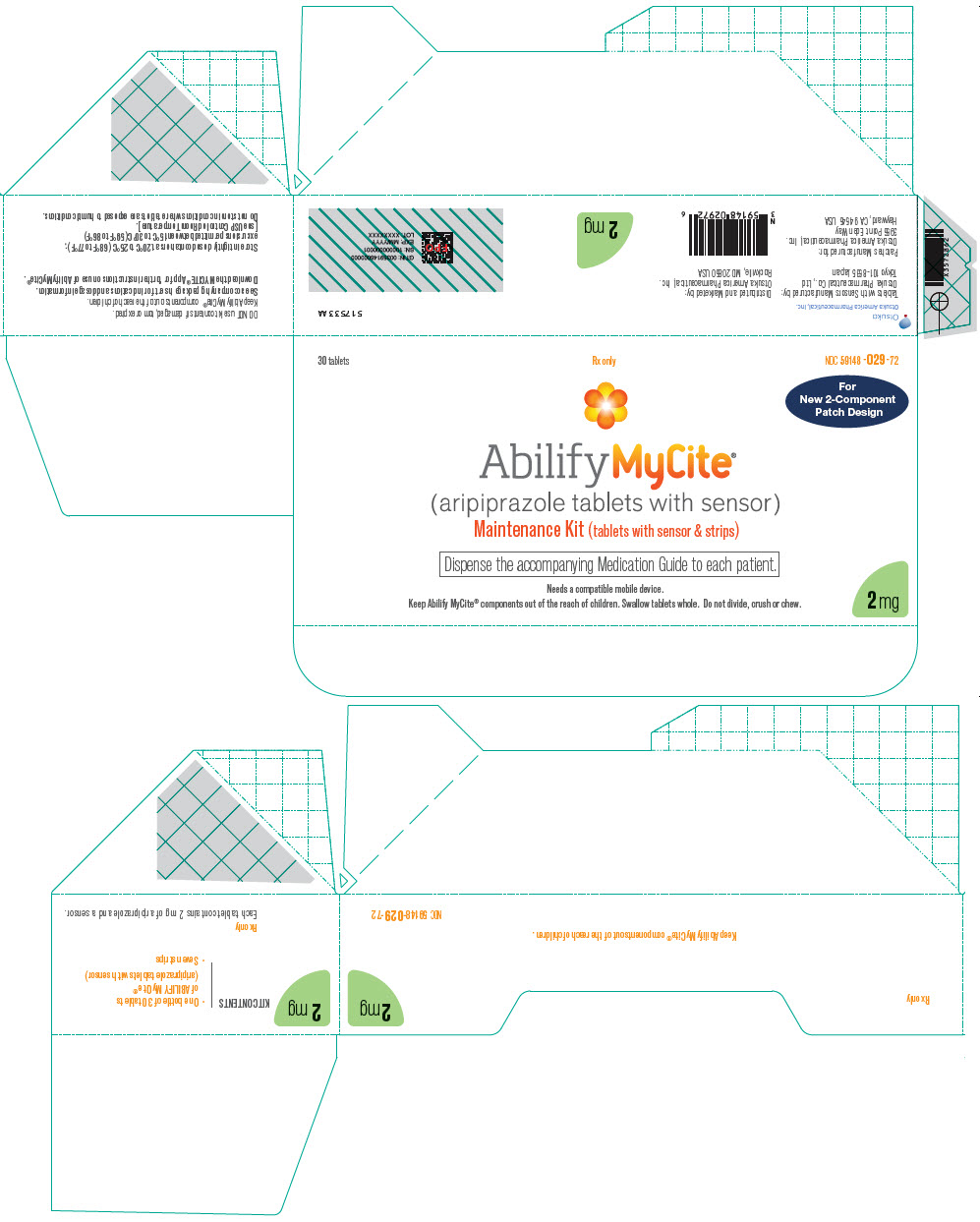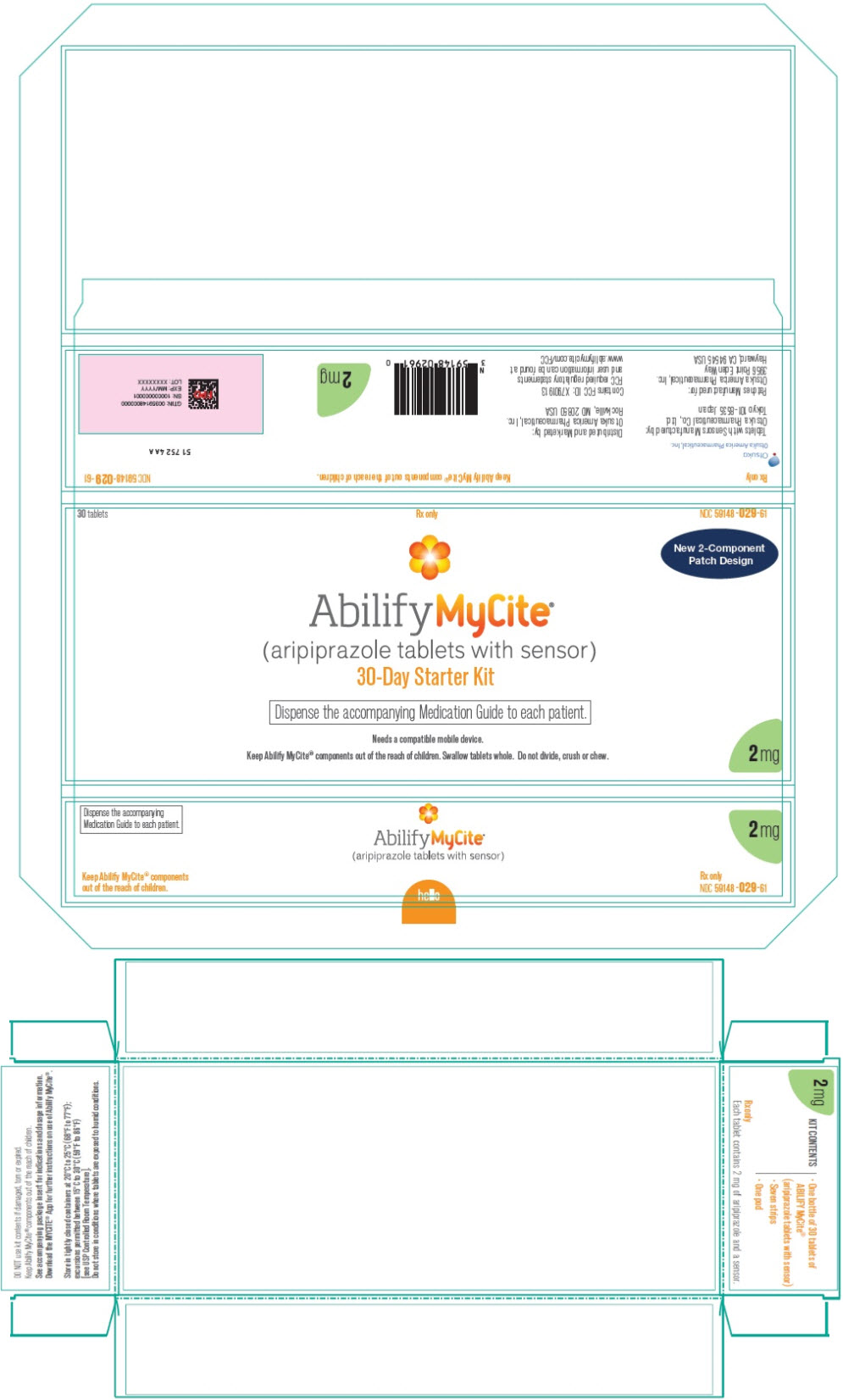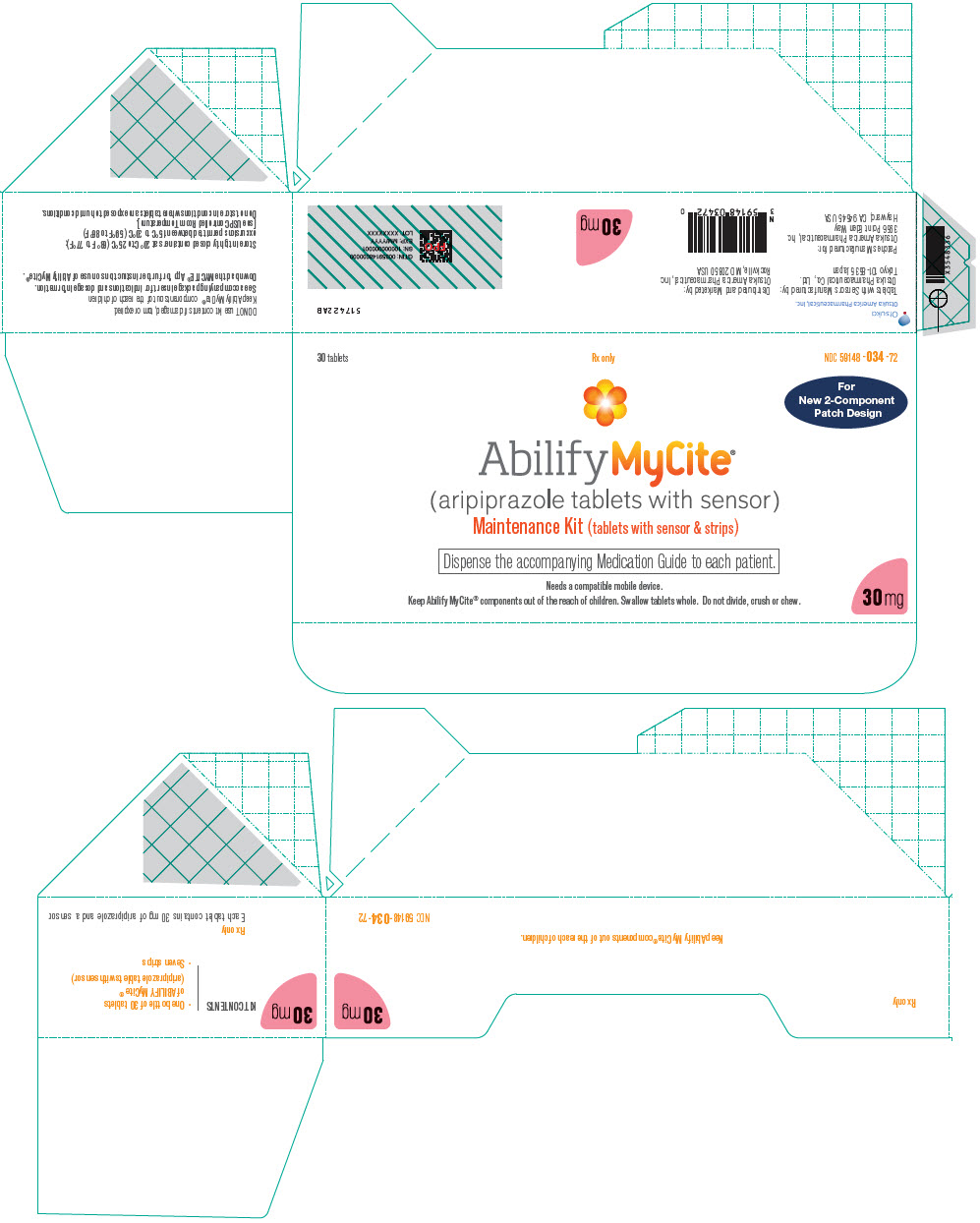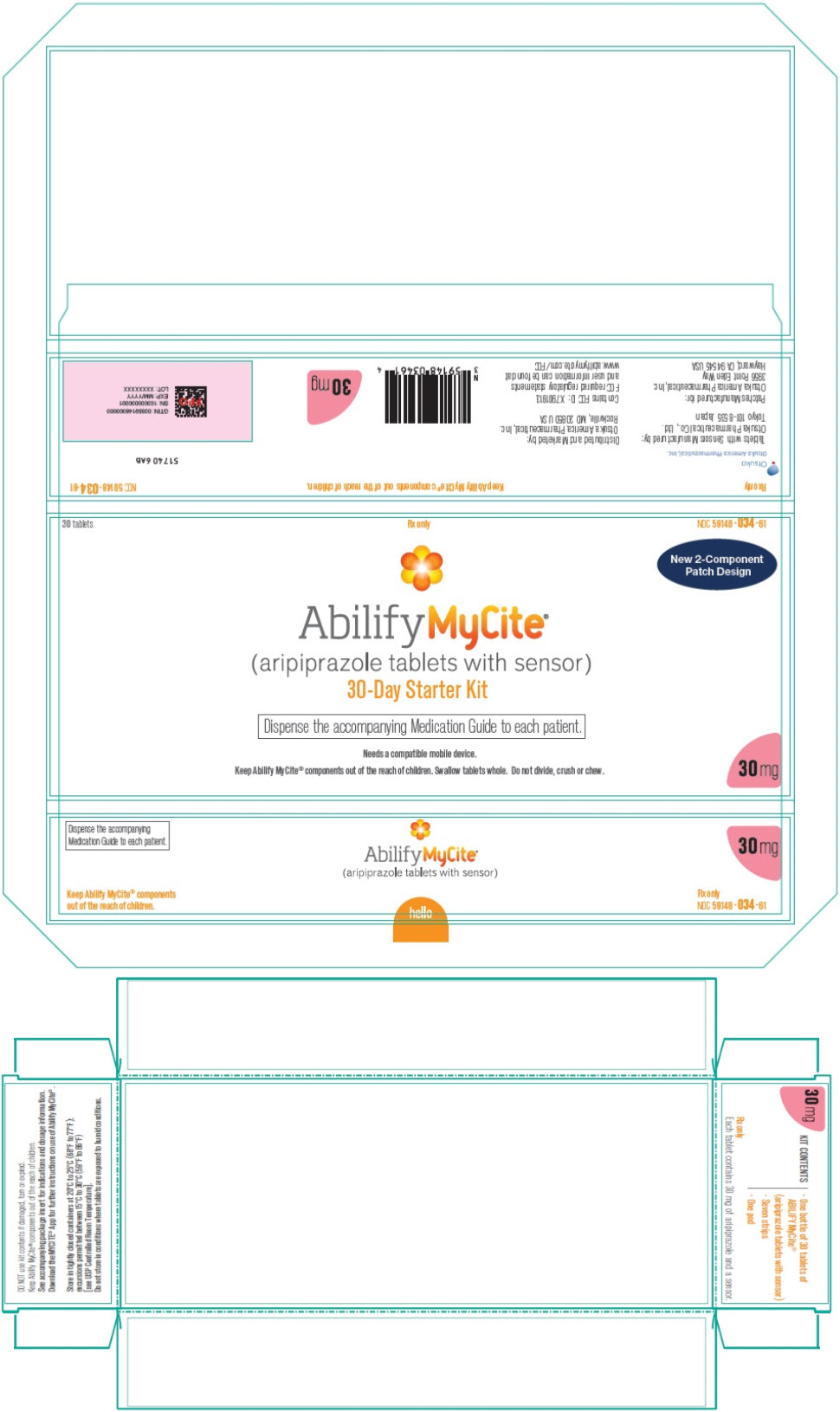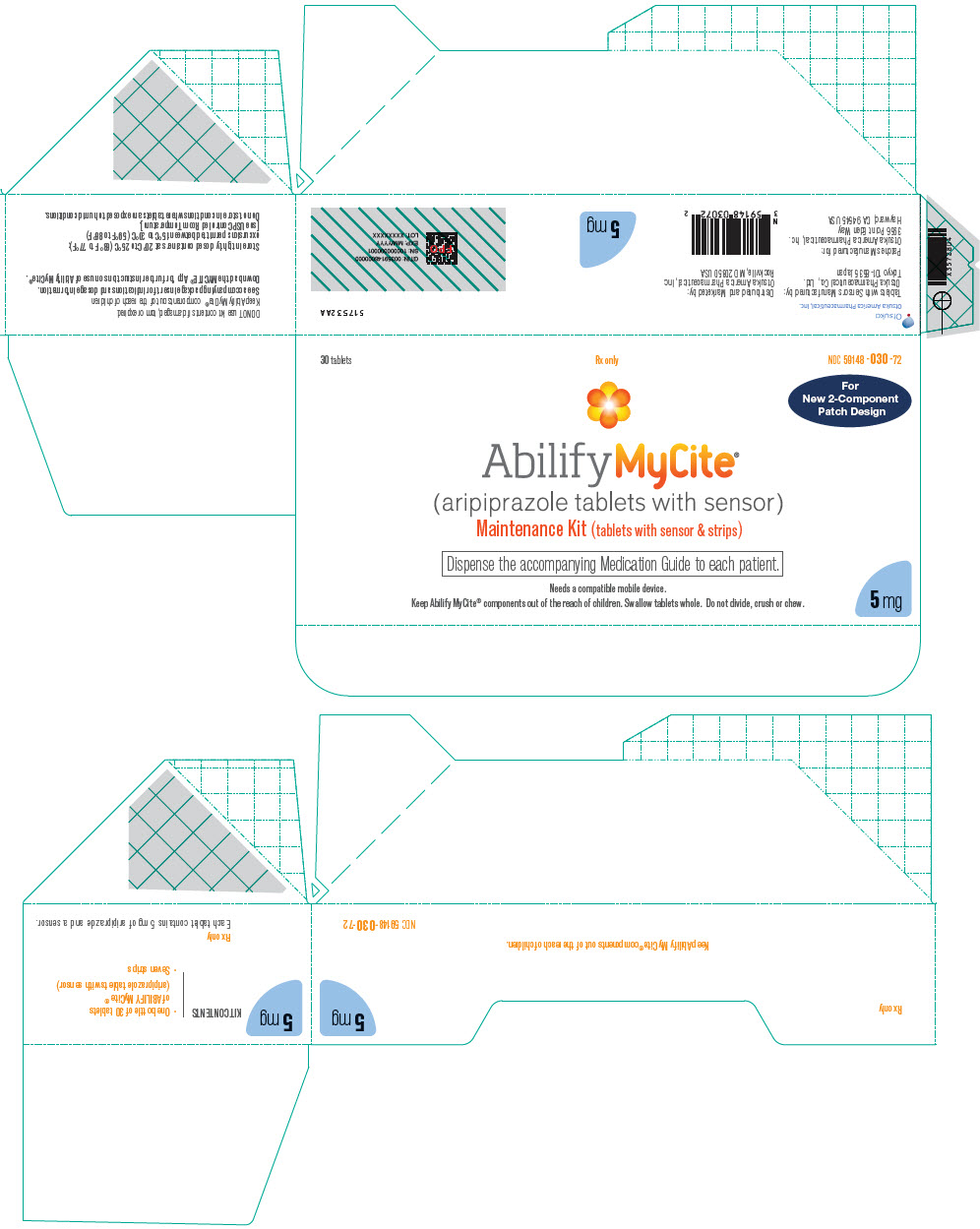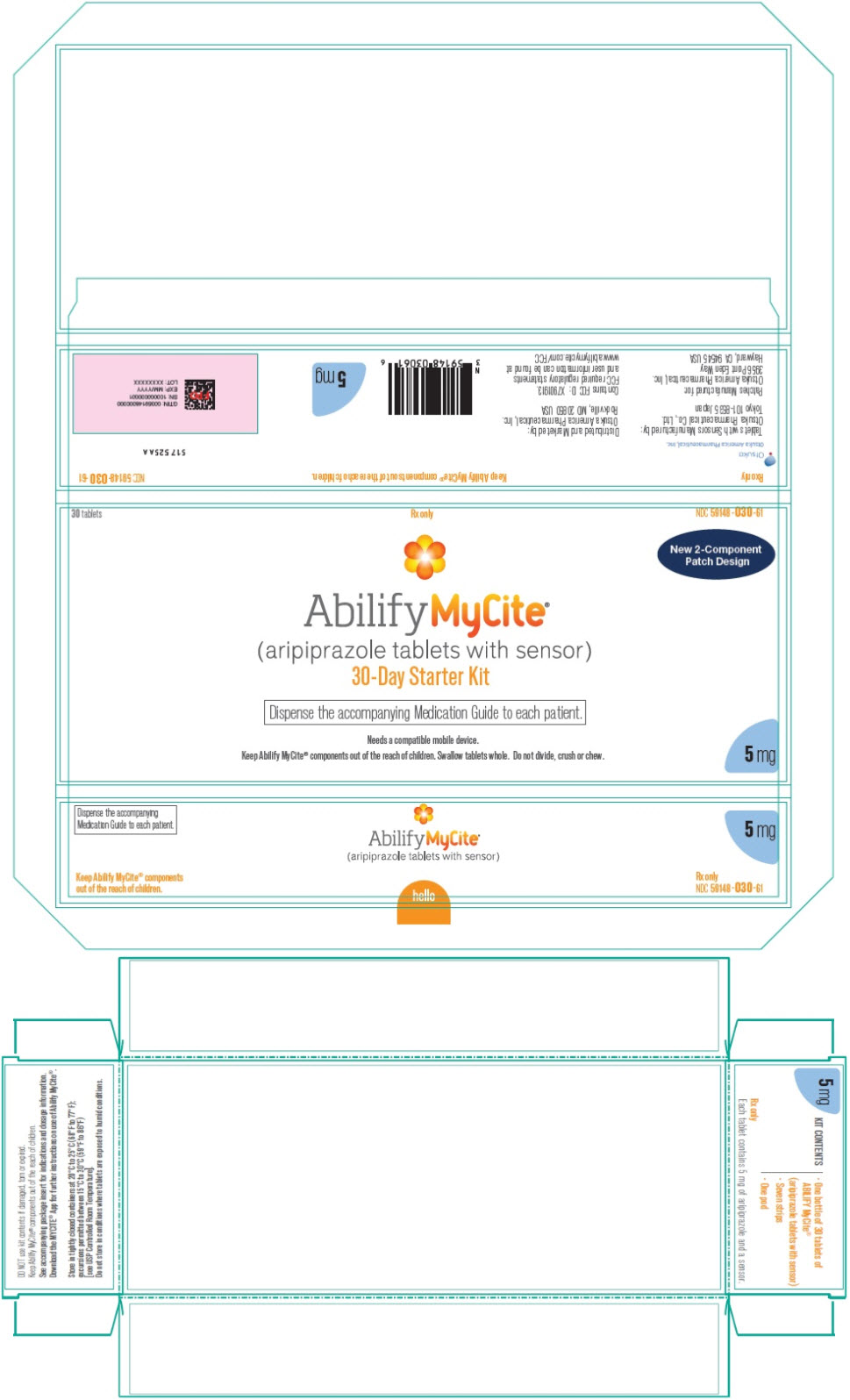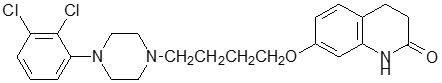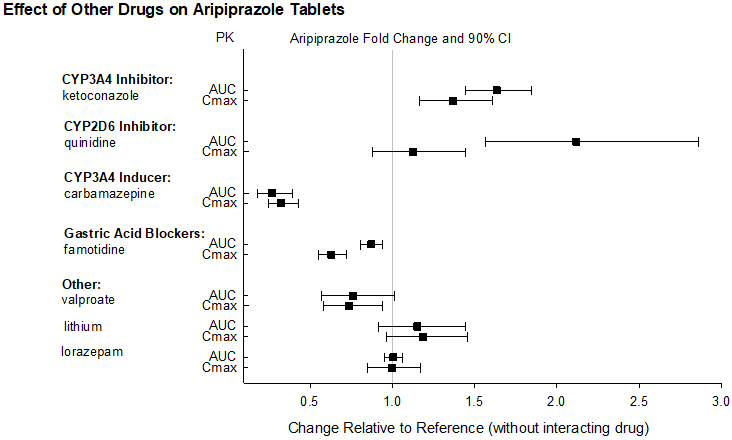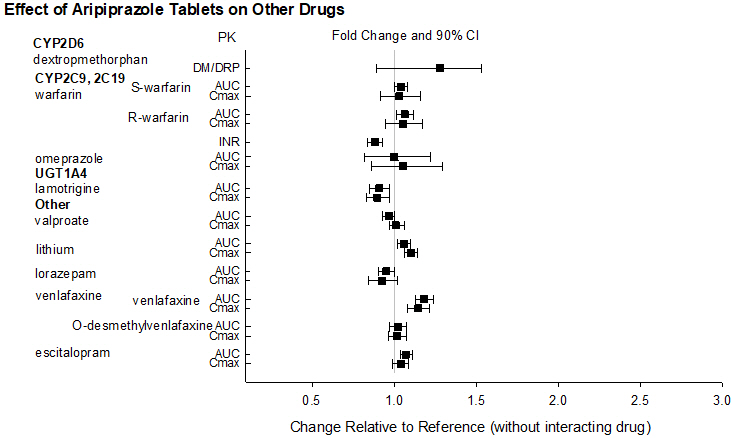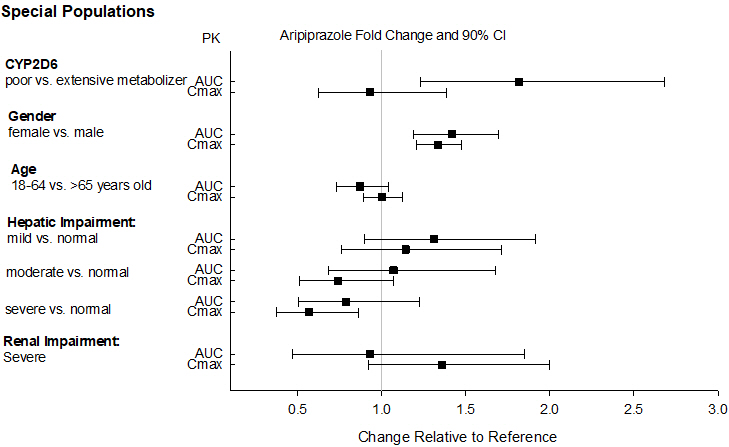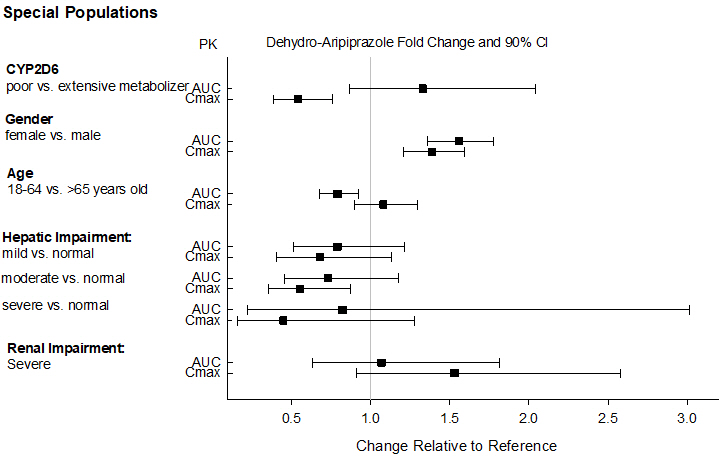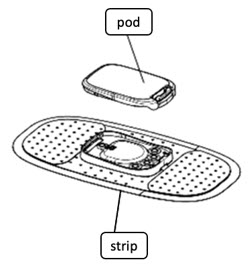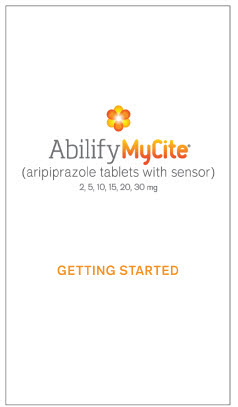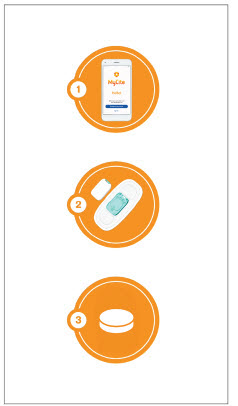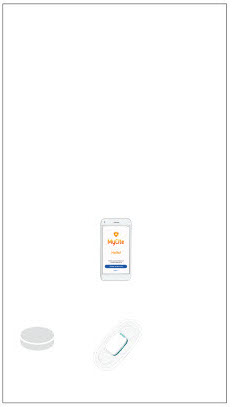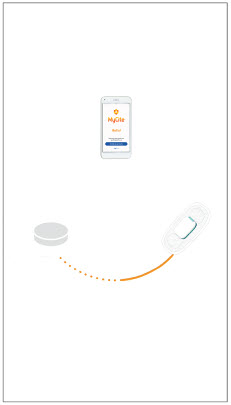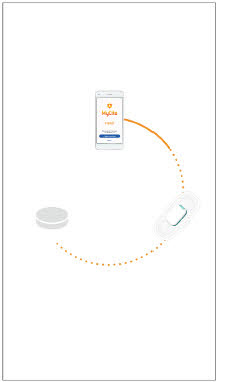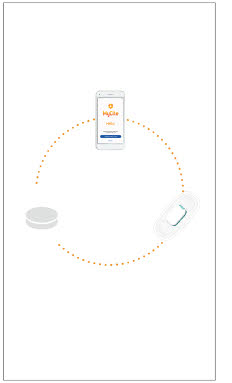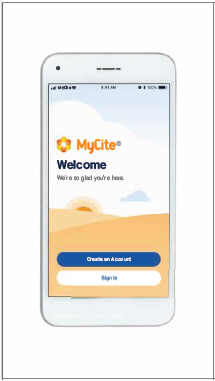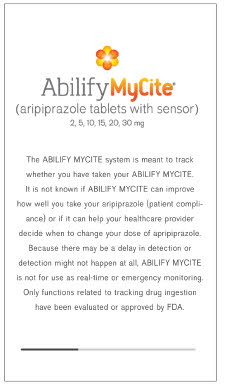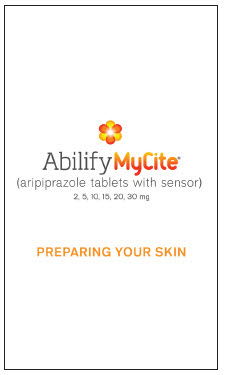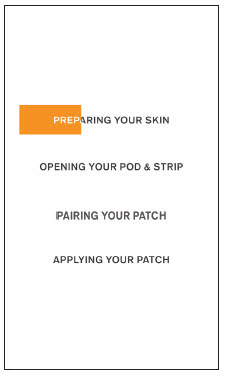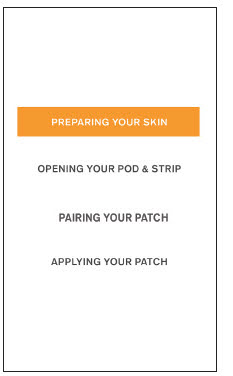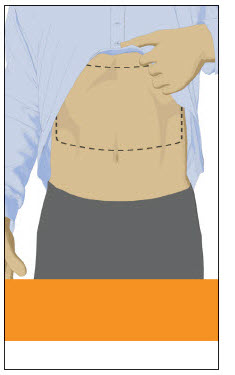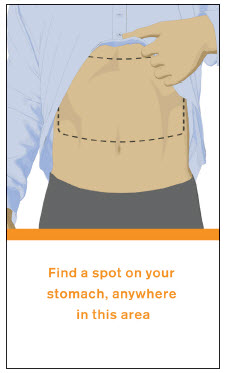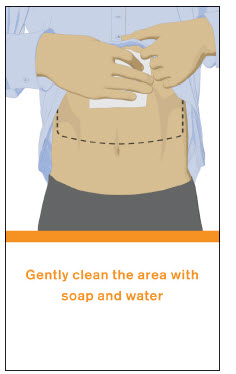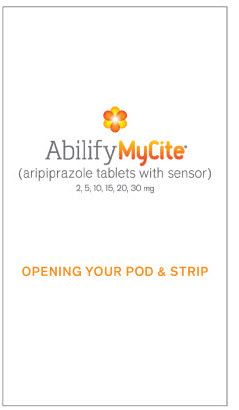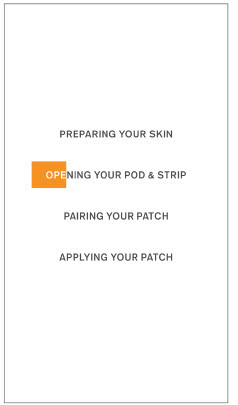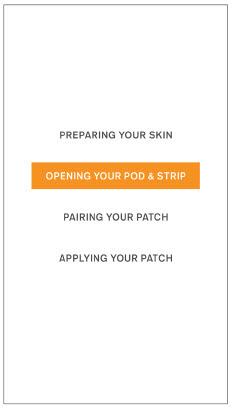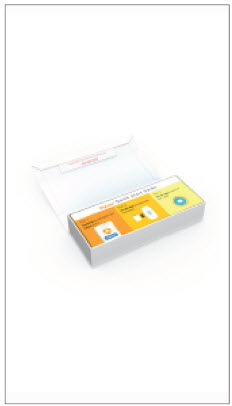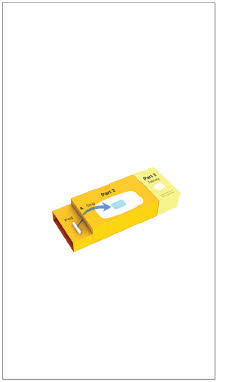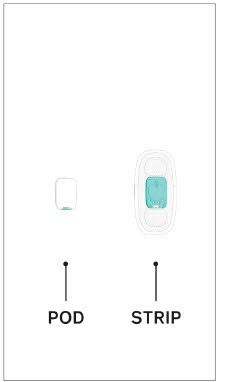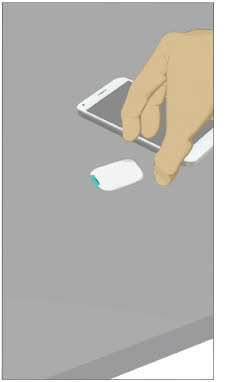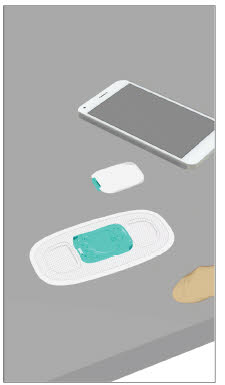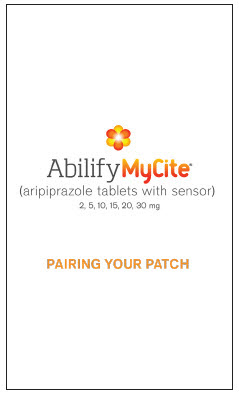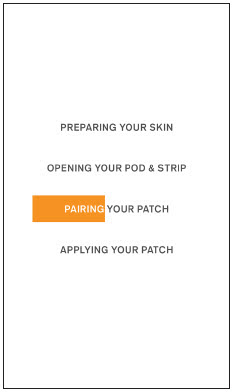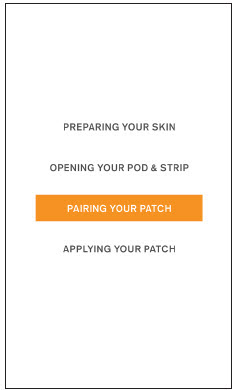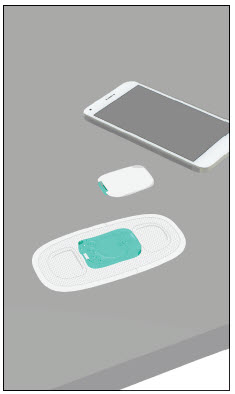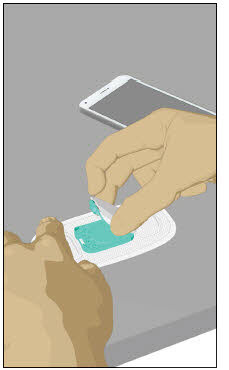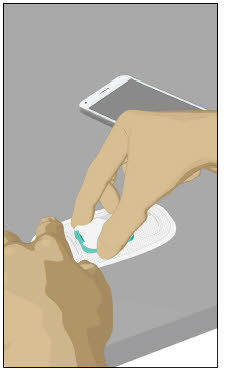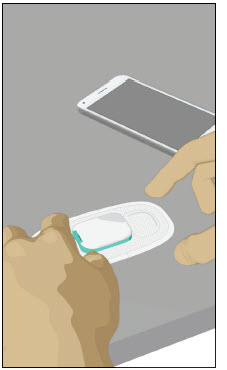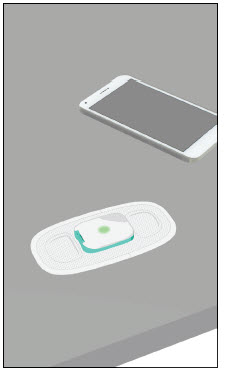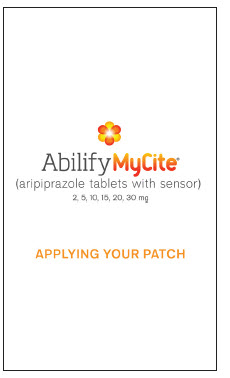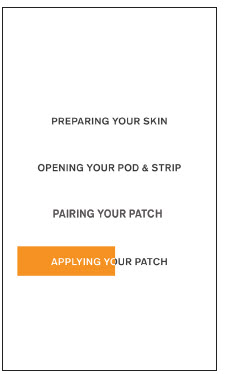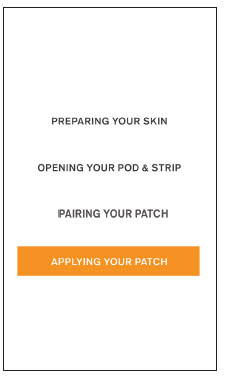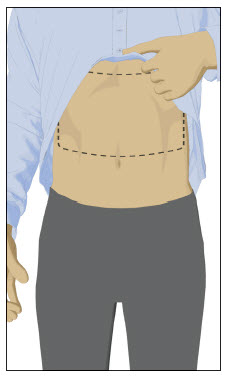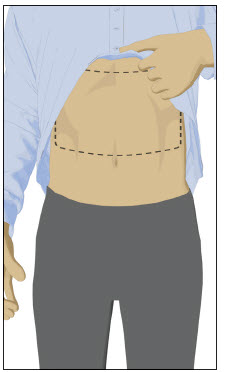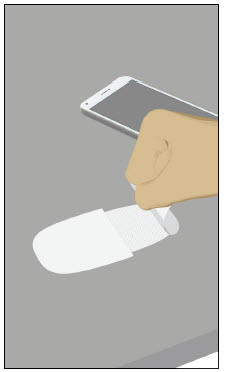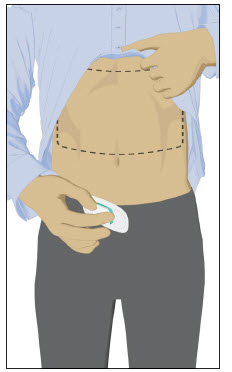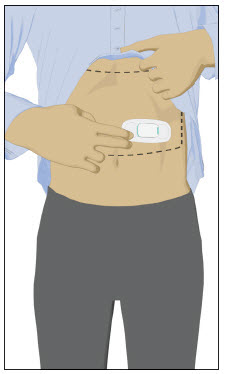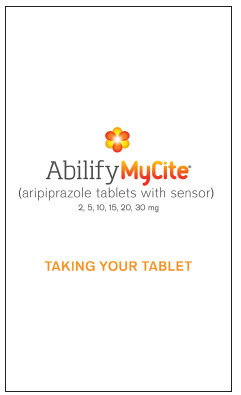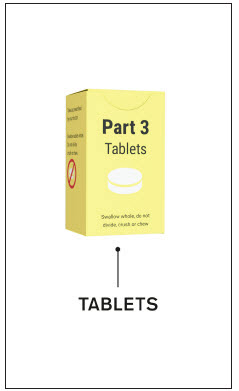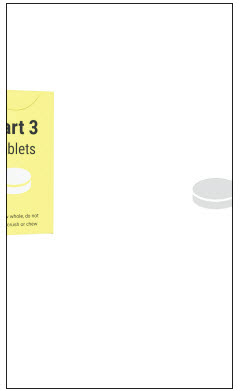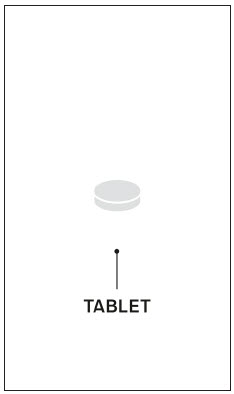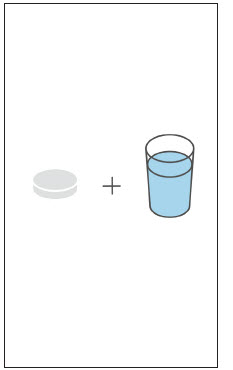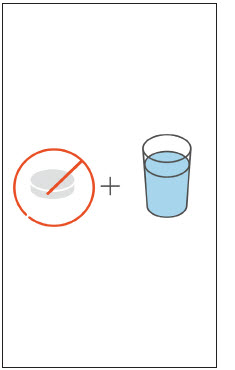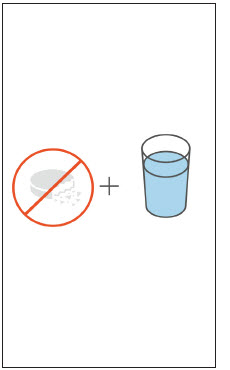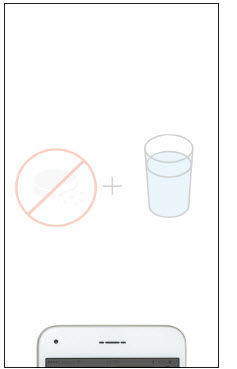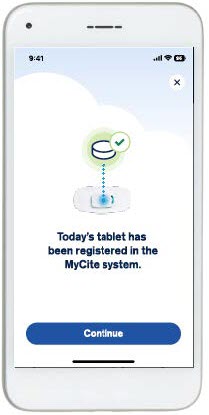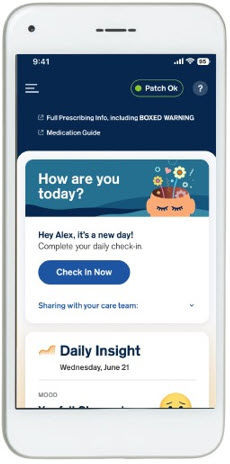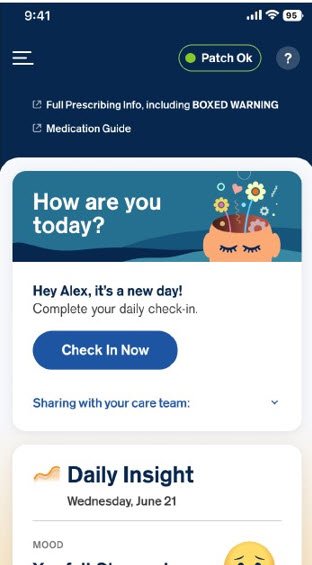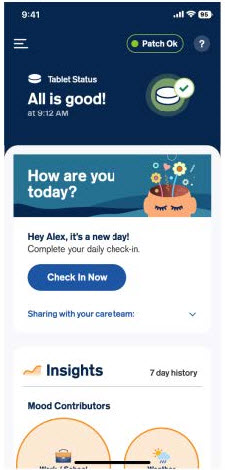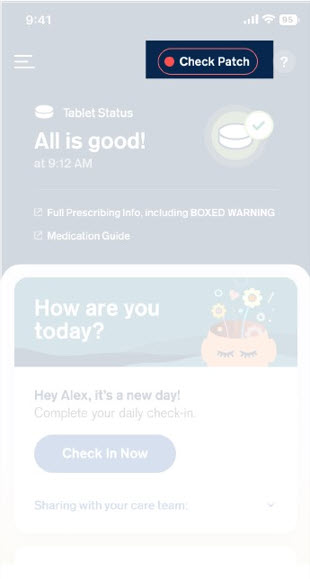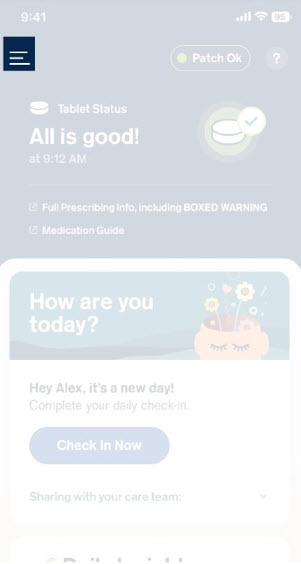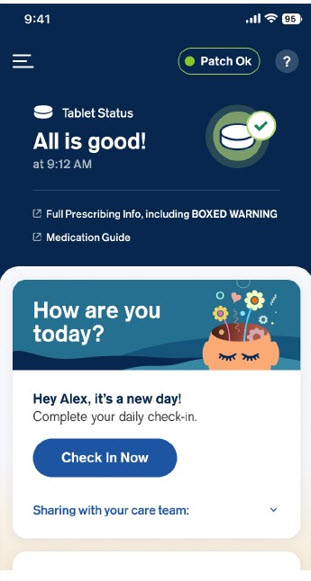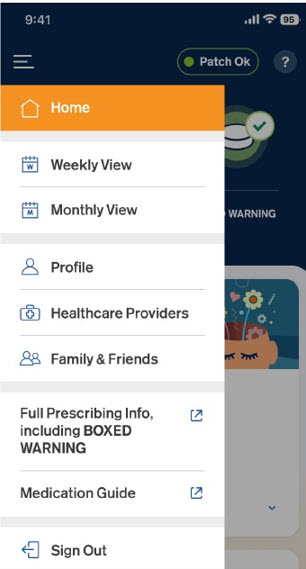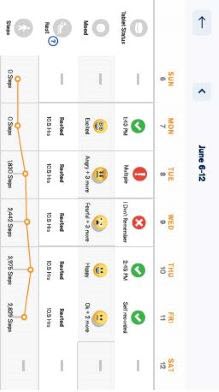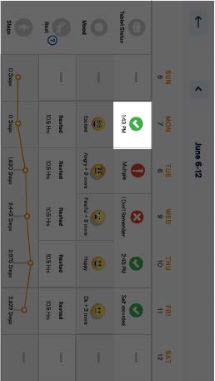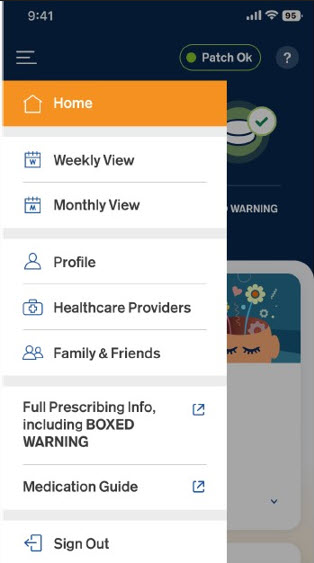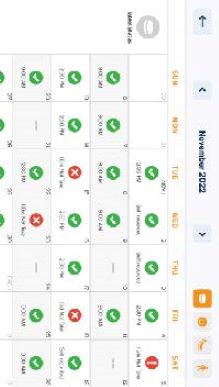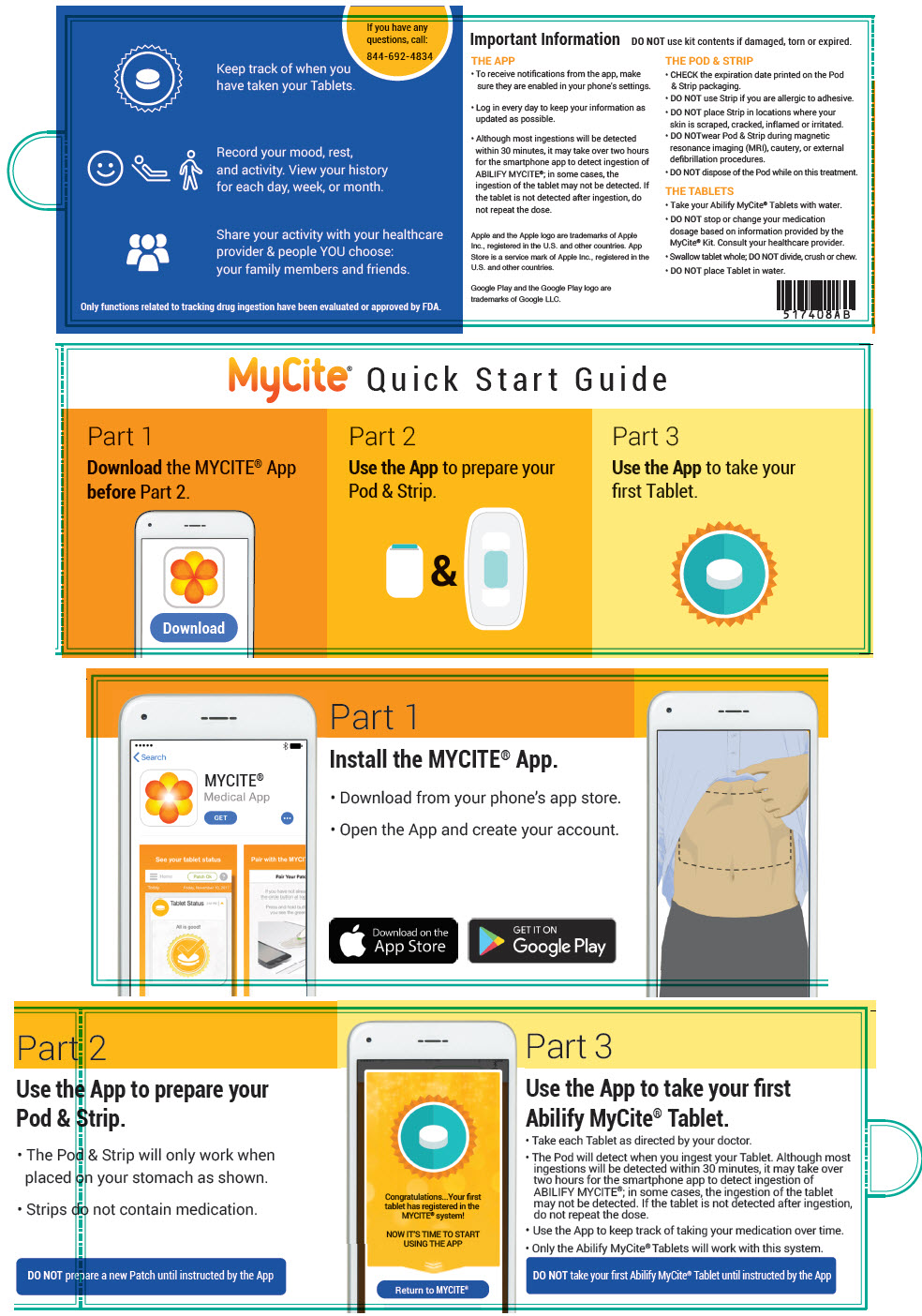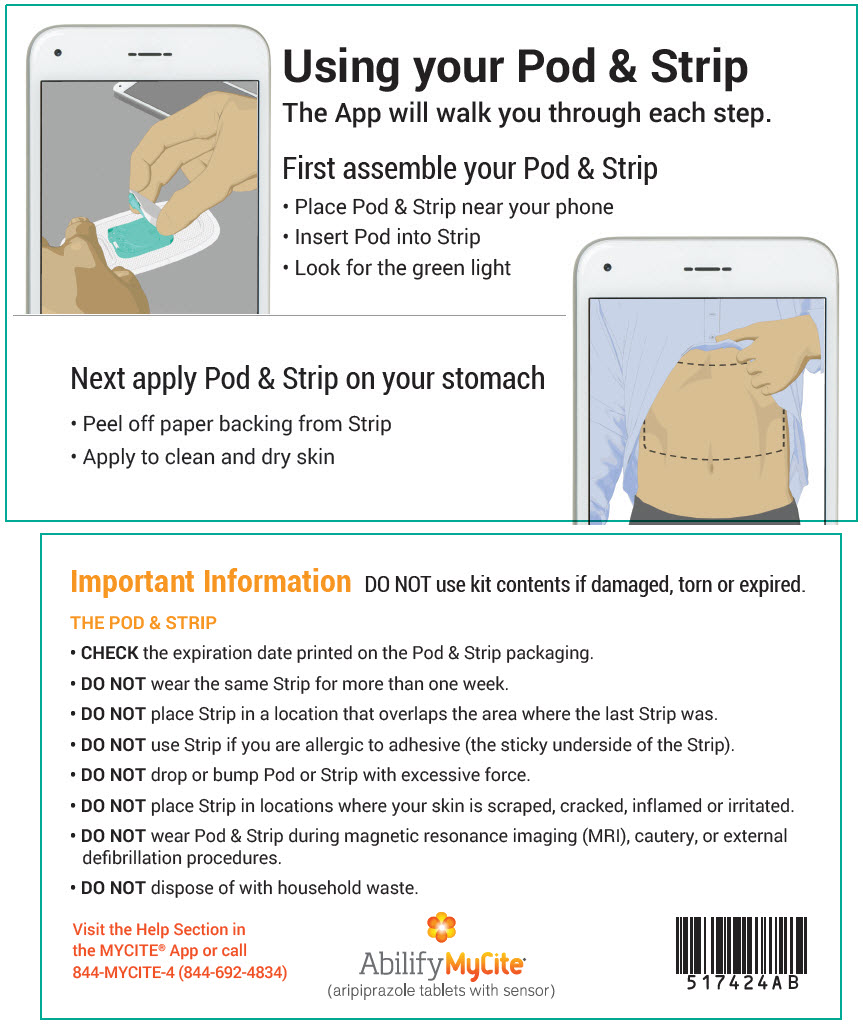 DRUG LABEL: Abilify MyCite
NDC: 59148-029 | Form: TABLET WITH SENSOR
Manufacturer: Otsuka America Pharmaceutical, Inc.
Category: prescription | Type: HUMAN PRESCRIPTION DRUG LABEL
Date: 20250131

ACTIVE INGREDIENTS: ARIPIPRAZOLE 2 mg/1 1
INACTIVE INGREDIENTS: STARCH, CORN; HYDROXYPROPYL CELLULOSE, UNSPECIFIED; LACTOSE MONOHYDRATE; MAGNESIUM STEARATE; MICROCRYSTALLINE CELLULOSE; FERRIC OXIDE YELLOW; FD&C BLUE NO. 2; ALUMINUM; CUPROUS CHLORIDE; ETHYLCELLULOSE, UNSPECIFIED; GOLD; MAGNESIUM; SILICON; SILICON DIOXIDE; SILICON NITRIDE; TITANIUM; TRIETHYL CITRATE

HIGHLIGHTS OF PRESCRIBING INFORMATION

These highlights do not include all the information needed to use ABILIFY MYCITE safely and effectively. See full prescribing information for ABILIFY MYCITE.
ABILIFY MYCITE® (aripiprazole tablets with sensor), for oral use
Initial U.S. Approval: 2002

WARNING: INCREASED MORTALITY IN ELDERLY PATIENTS WITH DEMENTIA-RELATED PSYCHOSIS and SUICIDAL THOUGHTS AND BEHAVIORS

See full prescribing information for complete boxed warning.

- Elderly patients with dementia-related psychosis treated with antipsychotic drugs are at an increased risk of death. ABILIFY MYCITE is not approved for the treatment of patients with dementia-related psychosis. (5.1)
- Increased risk of suicidal thoughts and behaviors in pediatric and young adult patients taking antidepressants. Closely monitor for worsening and emergence of suicidal thoughts and behaviors. (5.2)
- The safety and effectiveness of ABILIFY MYCITE have not been established in pediatric patients. (8.4)

1 INDICATIONS AND USAGE

ABILIFY MYCITE, a drug-device combination product comprised of aripiprazole tablets embedded with an Ingestible Event Marker (IEM) sensor intended to track drug ingestion, is indicated for the:

- Treatment of adults with schizophrenia (1)
- Treatment of bipolar I disorder (1)
  - Acute treatment of adults with manic and mixed episodes as monotherapy and as adjunct to lithium or valproate
  - Maintenance treatment of adults as monotherapy and as adjunct to lithium or valproate
- Adjunctive treatment of adults with major depressive disorder (MDD) (1)

Limitations of Use:

- The ability of ABILIFY MYCITE to improve patient compliance or modify aripiprazole dosage has not been established. (1)
- The use of ABILIFY MYCITE to track drug ingestion in "real-time" or during an emergency is not recommended because detection may be delayed or not occur. (1)

2 DOSAGE AND ADMINISTRATION

 | Initial Dose | Recommended Dose | Maximum Dose
Schizophrenia – adults (2.3) | 10 to 15 mg/day | 10 to 15 mg/day | 30 mg/day
Bipolar mania – adults: monotherapy (2.4) | 15 mg/day | 15 mg/day | 30 mg/day
Bipolar mania – adults: adjunct to lithium or valproate (2.4) | 10 to 15 mg/day | 15 mg/day | 30 mg/day
Major Depressive Disorder – adults: adjunct to antidepressants (2.5) | 2 to 5 mg/day | 5 to 10 mg/day | 15 mg/day

- Administer once daily without regard to meals (2.2)
- Swallow whole; do not divide, crush, or chew (2.2)
- Known CYP2D6 poor metabolizers: Administer half of the usual dose (2.6)

3 DOSAGE FORMS AND STRENGTHS

Tablets with sensor: 2 mg, 5 mg, 10 mg, 15 mg, 20 mg, and 30 mg (3)

4 CONTRAINDICATIONS

Known hypersensitivity to aripiprazole tablets (4)

5 WARNINGS AND PRECAUTIONS

- Cerebrovascular Adverse Reactions in Elderly Patients with Dementia-Related Psychosis: Increased incidence of cerebrovascular adverse reactions (e.g., stroke, transient ischemic attack, including fatalities) (5.3)
- Neuroleptic Malignant Syndrome: Manage with immediate discontinuation and close monitoring (5.4)
- Tardive Dyskinesia: Discontinue if clinically appropriate (5.5)
- Metabolic Changes: Monitor for hyperglycemia/diabetes mellitus, dyslipidemia, and weight gain (5.6)
- Pathological Gambling and other Compulsive Behaviors: Consider dose reduction or discontinuation (5.7)
- Orthostatic Hypotension: Monitor heart rate and blood pressure and warn patients with known cardiovascular or cerebrovascular disease, and risk of dehydration or syncope (5.8)
- Leukopenia, Neutropenia, and Agranulocytosis: Perform complete blood cell counts in patients with a history of a clinically significant low white blood cell count (WBC)/absolute neutrophil count (ANC). Consider discontinuation if clinically significant decline in WBC/ANC in the absence of other causative factors (5.10)
- Seizures: Use cautiously in patients with a history of seizures or with conditions that lower the seizure threshold (5.11)
- Potential for Cognitive and Motor Impairment: Use caution when operating machinery (5.12)

6 ADVERSE REACTIONS

Commonly observed adverse reactions (incidence ≥5% and at least twice that for placebo) in adult patients (6.1):

- Schizophrenia: akathisia
- Bipolar mania (monotherapy): akathisia, sedation, restlessness, tremor, and extrapyramidal disorder
- Bipolar mania (adjunctive therapy with lithium or valproate): akathisia, insomnia, and extrapyramidal disorder
- MDD (adjunctive treatment to antidepressant therapy): akathisia, restlessness, insomnia, constipation, fatigue, and blurred vision

To report SUSPECTED ADVERSE REACTIONS, contact Otsuka America Pharmaceutical, Inc. at 1-800-438-9927 or FDA at 1-800-FDA-1088 or www.fda.gov/medwatch.

7 DRUG INTERACTIONS

Dosage adjustment due to drug interactions and CYP2D6 poor metabolizers (7.1):

Factors | Dosage Adjustments for ABILIFY MYCITE
Known CYP2D6 Poor Metabolizers | Administer half recommended dose
Known CYP2D6 Poor Metabolizers and strong CYP3A4 inhibitors | Administer a quarter of recommended dose
Strong CYP2D6 or CYP3A4 inhibitors | Administer half recommended dose
Strong CYP2D6 and CYP3A4 inhibitors | Administer a quarter of recommended dose
Strong CYP3A4 inducers | Double recommended dose over 1 to 2 weeks

8 USE IN SPECIFIC POPULATIONS

Pregnancy: May cause extrapyramidal and/or withdrawal symptoms in neonates with third trimester exposure (8.1)

Lactation: Monitor the breastfed infant for dehydration and lack of appropriate weight gain (8.2)

FULL PRESCRIBING INFORMATION

WARNING: INCREASED MORTALITY IN ELDERLY PATIENTS WITH DEMENTIA-RELATED PSYCHOSIS and SUICIDAL THOUGHTS AND BEHAVIORS

Increased Mortality in Elderly Patients with Dementia-Related Psychosis

Elderly patients with dementia-related psychosis treated with antipsychotic drugs are at an increased risk of death. ABILIFY MYCITE is not approved for the treatment of patients with dementia-related psychosis [see Warnings and Precautions (5.1)].

Suicidal Thoughts and Behaviors

Antidepressants increased the risk of suicidal thoughts and behaviors in pediatric and young adult patients in short-term studies. Closely monitor all antidepressant-treated patients for clinical worsening, and for emergence of suicidal thoughts and behaviors [see Warnings and Precautions (5.2)]. The safety and efficacy of ABILIFY MYCITE have not been established in pediatric patients [see Use in Specific Populations (8.4)].

1 INDICATIONS AND USAGE

ABILIFY MYCITE, a drug-device combination product comprised of aripiprazole tablets embedded with an Ingestible Event Marker (IEM) sensor intended to track drug ingestion, is indicated for the:

- Treatment of adults with schizophrenia.
- Treatment of bipolar I disorder
  - Acute treatment of adults with manic and mixed episodes as monotherapy and as adjunct to lithium or valproate.
  - Maintenance treatment of adults as monotherapy and as adjunct to lithium or valproate.
- Adjunctive treatment of adults with Major Depressive Disorder.

Limitations of Use:

- The ability of the ABILIFY MYCITE to improve patient compliance or modify aripiprazole dosage has not been established [see Dosage and Administration (2.1)].
- The use of ABILIFY MYCITE to track drug ingestion in "real-time" or during an emergency is not recommended because detection may be delayed or not occur [see Dosage and Administration (2.1)].

2 DOSAGE AND ADMINISTRATION

2.1 Overview of the ABILIFY MYCITE System

The ABILIFY MYCITE System is composed of the following:

- Aripiprazole tablet embedded with an IEM sensor (ABILIFY MYCITE);
- MYCITE® Patch (wearable sensor) that detects the signal from the IEM sensor after ingestion and transmits data to a smartphone (referred to as the patch);
- MYCITE App - a smartphone application which is used with a compatible smartphone to display information for the patient (referred to as the app);
- Web-based portal for healthcare professionals and caregivers

Prior to initial patient use of the ABILIFY MYCITE System, facilitate use of ABILIFY MYCITE and the patch, app, and portal; ensure the patient is capable and willing to use a smartphone and the app; and instruct patients to [see How Supplied/Storage and Handling (16.1)]:

- Download the app,
- Follow all the instructions in the Instructions for Use within the app and the Quick Start Guide within the carton, and
- Ensure that the app is compatible with their specific smartphone and is paired with the patch prior to use.

Prior to prescribing the ABILIFY MYCITE Maintenance Kit ensure the patient has access to the appropriate components of the patch [see How Supplied/Storage and Handling (16.1)].

Although most ingestions will be detected within 30 minutes, it may take up to two hours for the app and portal to detect the ingestion of ABILIFY MYCITE; in some cases, the ingestion of the tablet with sensor may not be detected. If the tablet with sensor is not detected after ingestion, do not repeat the dose [see Adverse Reactions (6)].

2.2 Administration Instructions

ABILIFY MYCITE

Administer ABILIFY MYCITE orally with or without food [see Clinical Pharmacology (12.3)]. Swallow tablets with sensor whole; do not divide, crush, or chew.

MYCITE Patch

Refer to the Instructions for Use (IFU) within the app [see How Supplied/Storage and Handling (16.1)]:

- Apply only when instructed by the app to the right or left side of the body just above the lower edge of the rib cage.

Additional patch instructions:

- Do not place the patch in areas where the skin is scraped, cracked, inflamed, or irritated, or in a location that overlaps the area of the most recently removed patch (if there is skin irritation, instruct patients to remove the patch).
- The app will prompt the patient to change the patch (at least weekly or sooner), and to apply and remove the patch correctly.
- Keep the patch on when showering, swimming, or exercising.
- For those undergoing an MRI, remove the patch and replace with a new patch as soon as possible.

2.3 Dosage in Schizophrenia

The recommended starting and target dosage for ABILIFY MYCITE in adults with schizophrenia is 10 or 15 mg daily. Dosage increases should generally not be made before 2 weeks [see Clinical Pharmacology (12.3)]. The maximum recommended dosage is 30 mg daily; however, doses above 15 mg daily have shown no additional clinically meaningful benefit.

2.4 Dosage in Bipolar I Disorder

The recommended starting dosage in adults with acute and mixed episodes associated with bipolar I disorder is 15 mg given once daily as monotherapy and 10 mg to 15 mg given once daily as adjunctive treatment with lithium or valproate. The recommended target dose of ABILIFY MYCITE is 15 mg daily, as monotherapy or as adjunctive treatment with lithium or valproate. The dosage may be increased to 30 mg daily based on clinical response. The maximum recommended daily dosage is 30 mg.

2.5 Dosage in Adjunctive Treatment of Major Depressive Disorder

The recommended starting dose for ABILIFY MYCITE as adjunctive treatment of adults with MDD taking an antidepressant is 2 to 5 mg daily. The recommended dosage range is 2 to 15 mg daily. Dosage adjustments of up to 5 mg daily should occur gradually, at intervals of no less than one week. The maximum recommended daily dosage is 15 mg. Periodically reassess to determine the continued need for maintenance treatment.

2.6 Dosage Adjustments for Cytochrome P450 Considerations

Dosage adjustments are recommended in patients who are known CYP2D6 poor metabolizers and in patients taking concomitant CYP3A4 inhibitors or CYP2D6 inhibitors or strong CYP3A4 inducers (see Table 1). When the coadministered drug is withdrawn from the combination therapy, ABILIFY MYCITE dosage should then be adjusted to its original level. When the coadministered CYP3A4 inducer is withdrawn, ABILIFY MYCITE dosage should be reduced to the original level over 1 to 2 weeks. Patients who may be receiving a combination of strong, moderate, and weak inhibitors of CYP3A4 and CYP2D6 (e.g., a strong CYP3A4 inhibitor and a moderate CYP2D6 inhibitor or a moderate CYP3A4 inhibitor with a moderate CYP2D6 inhibitor), the dosing may be reduced to one-quarter (25%) of the usual dose initially and then adjusted based on clinical response.

Table 1: Dose Adjustments for ABILIFY MYCITE in Patients Who Are Known CYP2D6 Poor Metabolizers and Patients Taking Concomitant CYP2D6 Inhibitors, 3A4 Inhibitors, and/or CYP3A4 Inducers
Factors | Dosage Adjustments for ABILIFY MYCITE
Known CYP2D6 Poor Metabolizers | Administer half of recommended dose
Known CYP2D6 Poor Metabolizers taking concomitant strong CYP3A4 inhibitors (e.g., itraconazole, clarithromycin) | Administer a quarter of recommended dose
Strong CYP2D6 (e.g., quinidine, fluoxetine, paroxetine) or CYP3A4 inhibitors (e.g., itraconazole, clarithromycin) | Administer half of recommended dose
Strong CYP2D6 and CYP3A4 inhibitors | Administer a quarter of recommended dose
Strong CYP3A4 inducers (e.g., carbamazepine, rifampin) | Double recommended dose over 1 to 2 weeks

When adjunctive ABILIFY MYCITE is administered to patients with major depressive disorder, ABILIFY MYCITE should be administered without dosage adjustment as specified in [Dosage and Administration (2.5)].

3 DOSAGE FORMS AND STRENGTHS

ABILIFY MYCITE (aripiprazole tablets with sensor) is available as described in Table 2.

Table 2: ABILIFY MYCITE Presentations
Strength | Color/Shape | Markings
2 mg | pale green modified rectangle | "DA-029" and "2"
5 mg | pale blue modified rectangle | "DA-030" and "5"
10 mg | off-white to pale pink modified rectangle | "DA-031" and "10"
15 mg | pale yellow round | "DA-032" and "15"
20 mg | white to pale yellowish white round | "DA-033" and "20"
30 mg | off-white to pale pink round | "DA-034" and "30"

4 CONTRAINDICATIONS

ABILIFY MYCITE is contraindicated in patients with a history of a hypersensitivity reaction to aripiprazole. Reactions have ranged from pruritus/urticaria to anaphylaxis [see Adverse Reactions (6.2)].

5 WARNINGS AND PRECAUTIONS

5.1 Increased Mortality in Elderly Patients with Dementia-Related Psychosis

Elderly patients with dementia-related psychosis treated with antipsychotic drugs are at an increased risk of death. Analyses of 17 placebo-controlled trials (modal duration of 10 weeks), largely in patients taking atypical antipsychotic drugs, revealed a risk of death in drug-treated patients of between 1.6 to 1.7 times the risk of death in placebo-treated patients. Over the course of a typical 10-week controlled trial, the rate of death in drug-treated patients was about 4.5%, compared to a rate of about 2.6% in the placebo group.

Although the causes of death were varied, most of the deaths appeared to be either cardiovascular (e.g., heart failure, sudden death) or infectious (e.g., pneumonia) in nature. Observational studies suggest that, similar to atypical antipsychotic drugs, treatment with conventional antipsychotic drugs may increase mortality. The extent to which the findings of increased mortality in observational studies may be attributed to the antipsychotic drug as opposed to some characteristic(s) of the patients is not clear. ABILIFY MYCITE is not approved for the treatment of patients with dementia-related psychosis [see Boxed Warning, and Warnings and Precautions (5.3)].

5.2 Suicidal Thoughts and Behaviors in Pediatric and Young Adult Patients

In pooled analyses of placebo-controlled trials of antidepressant drugs (SSRIs and other antidepressant classes) that included approximately 77,000 adult patients and over 4,400 pediatric patients, the incidence of suicidal thoughts and behaviors in pediatric and young adult patients was greater in antidepressant-treated patients than in placebo-treated patients. The safety and efficacy of ABILIFY MYCITE have not been established in pediatric patients [see Use in Specific Populations (8.4)]. The drug-placebo differences in the number of cases of suicidal thoughts and behaviors per 1000 patients treated are provided in Table 3.

No suicides occurred in any of the pediatric studies. There were suicides in the adult studies, but the number was not sufficient to reach any conclusion about antidepressant drug effect on suicide.

Table 3: Risk Differences of the Number of Cases of Suicidal Thoughts or Behaviors in the Pooled Placebo-Controlled Trials of Antidepressants in Pediatric and Adult Patients
Age Range (years) | Drug-Placebo Difference in Number of Patients with Suicidal Thoughts or Behaviors per 1000 Patients Treated
 | Increases Compared to Placebo
<18 | 14 additional patients
18 to 24 | 5 additional patients
 | Decreases Compared to Placebo
25 to 64 | 1 fewer patient
≥65 | 6 fewer patients

It is unknown whether the risk of suicidal thoughts and behaviors in pediatric and young adult patients extends to longer-term use, i.e., beyond four months. However, there is substantial evidence from placebo-controlled maintenance trials in adults with MDD that antidepressants delay the recurrence of depression.

Monitor all antidepressant-treated patients for clinical worsening and emergence of suicidal thoughts and behaviors, especially during the initial few months of drug therapy and at times of dosage changes. Counsel family members or caregivers of patients to monitor for changes in behavior and to alert the healthcare provider. Consider changing the therapeutic regimen, including possibly discontinuing ABILIFY MYCITE, in patients whose depression is persistently worse, or who are experiencing emergent suicidal thoughts or behaviors.

5.3 Cerebrovascular Adverse Reactions, Including Stroke, in Elderly Patients with Dementia-Related Psychosis

In placebo-controlled clinical studies (two flexible-dose and one fixed-dose study) of dementia-related psychosis, there was an increased incidence of cerebrovascular adverse events (e.g., stroke, transient ischemic attack), including fatalities, in aripiprazole-treated patients (mean age: 84 years; range: 78 to 88 years). In the fixed-dose study, there was a statistically significant dose-response relationship for cerebrovascular adverse events in patients treated with aripiprazole. ABILIFY MYCITE is not approved for the treatment of patients with dementia-related psychosis [see Boxed Warning].

5.4 Neuroleptic Malignant Syndrome (NMS)

A potentially fatal symptom complex sometimes referred to as Neuroleptic Malignant Syndrome (NMS) may occur with administration of antipsychotic drugs, including ABILIFY MYCITE. Clinical manifestations of NMS are hyperpyrexia, muscle rigidity, altered mental status, and evidence of autonomic instability (irregular pulse or blood pressure, tachycardia, diaphoresis, and cardiac dysrhythmia). Additional signs may include elevated creatine phosphokinase, myoglobinuria (rhabdomyolysis), and acute renal failure.

The diagnostic evaluation of patients with this syndrome is complicated. In arriving at a diagnosis, it is important to exclude cases where the clinical presentation includes both serious medical illness (e.g., pneumonia, systemic infection) and untreated or inadequately treated extrapyramidal signs and symptoms (EPS). Other important considerations in the differential diagnosis include central anticholinergic toxicity, heat-stroke, drug fever, and primary central nervous system pathology.

The management of NMS should include: 1) immediate discontinuation of antipsychotic drugs and other drugs not essential to concurrent therapy; 2) intensive symptomatic treatment and medical monitoring; and 3) treatment of any concomitant serious medical problems for which specific treatments are available. There is no general agreement about specific pharmacological treatment regimens for uncomplicated NMS.

If a patient requires antipsychotic drug treatment after recovery from NMS, the potential reintroduction of drug therapy should be carefully considered. The patient should be carefully monitored, since recurrences of NMS have been reported.

5.5 Tardive Dyskinesia

A syndrome of potentially irreversible, involuntary, dyskinetic movements may develop in patients treated with antipsychotic drugs, including ABILIFY MYCITE. Although the prevalence of the syndrome appears to be highest among the elderly, especially elderly women, it is impossible to rely upon prevalence estimates to predict, at the inception of antipsychotic treatment, which patients are likely to develop the syndrome. Whether antipsychotic drug products differ in their potential to cause tardive dyskinesia is unknown.

The risk of developing tardive dyskinesia and the likelihood that it will become irreversible are believed to increase as the duration of treatment and the total cumulative dose of antipsychotic drugs administered to the patient increase. However, the syndrome can develop, although much less commonly, after relatively brief treatment periods at low doses.

The syndrome may remit, partially or completely, if antipsychotic treatment is withdrawn. Antipsychotic treatment itself, however, may suppress (or partially suppress) the signs and symptoms of the syndrome and, thereby, may possibly mask the underlying process. The effect that symptomatic suppression has upon the long-term course of the syndrome is unknown.

Given these considerations, ABILIFY MYCITE should be prescribed in a manner that is most likely to minimize the occurrence of tardive dyskinesia. Chronic antipsychotic treatment should generally be reserved for patients who suffer from a chronic illness that (1) is known to respond to antipsychotic drugs and (2) for whom alternative, equally effective, but potentially less harmful treatments are not available or appropriate. In patients who do require chronic treatment, the smallest dose and the shortest duration of treatment producing a satisfactory clinical response should be sought. The need for continued treatment should be reassessed periodically.

If signs and symptoms of tardive dyskinesia appear in a patient on ABILIFY MYCITE, drug discontinuation should be considered. However, some patients may require treatment with ABILIFY MYCITE despite the presence of the syndrome.

5.6 Metabolic Changes

Atypical antipsychotic drugs have caused metabolic changes that include hyperglycemia, diabetes mellitus, dyslipidemia, and body weight gain. While all of the drugs in the class have been shown to produce some metabolic changes, each drug has its own specific risk profile.

Hyperglycemia/Diabetes Mellitus

Hyperglycemia, in some cases extreme and associated with ketoacidosis or hyperosmolar coma or death, has been reported in patients treated with atypical antipsychotics. There have been reports of hyperglycemia in patients treated with aripiprazole [see Adverse Reactions (6.1, 6.2)]. Assessment of the relationship between atypical antipsychotic use and glucose abnormalities is complicated by the possibility of an increased background risk of diabetes mellitus in patients with schizophrenia and the increasing incidence of diabetes mellitus in the general population. Given these confounders, the relationship between atypical antipsychotic use and hyperglycemia-related adverse events is not completely understood. However, epidemiological studies suggest an increased risk of hyperglycemia-related adverse reactions in patients treated with the atypical antipsychotics.

Patients with an established diagnosis of diabetes mellitus who are started on atypical antipsychotics should be monitored regularly for worsening of glucose control. Patients with risk factors for diabetes mellitus (e.g., obesity, family history of diabetes) who are starting treatment with atypical antipsychotics should undergo fasting blood glucose testing at the beginning of treatment and periodically during treatment. Any patient treated with atypical antipsychotics should be monitored for symptoms of hyperglycemia including polydipsia, polyuria, polyphagia, and weakness. Patients who develop symptoms of hyperglycemia during treatment with atypical antipsychotics should undergo fasting blood glucose testing. In some cases, hyperglycemia has resolved when the atypical antipsychotic was discontinued; however, some patients required continuation of anti-diabetic treatment despite discontinuation of the atypical antipsychotic drug.

In an analysis of 13 placebo-controlled monotherapy trials in adults, primarily with schizophrenia or bipolar disorder, the mean change in fasting glucose in aripiprazole -treated patients (+4.4 mg/dL; median exposure 25 days; N=1057) was not significantly different than in placebo-treated patients (+2.5 mg/dL; median exposure 22 days; N=799). Table 4 shows the proportion of aripiprazole-treated patients with normal and borderline fasting glucose at baseline (median exposure 25 days) that had treatment-emergent high fasting glucose measurements compared to placebo-treated patients (median exposure 22 days).

Table 4: Changes in Fasting Glucose in Placebo-Controlled Monotherapy Trials in Adult Patients (Primarily Schizophrenia and Bipolar Disorder)
 | Category Change (at least once) from Baseline | Treatment Arm | n/N | %
Fasting Glucose | Normal to High (<100 mg/dL to ≥126 mg/dL) | Aripiprazole | 31/822 | 3.8
Fasting Glucose | Normal to High (<100 mg/dL to ≥126 mg/dL) | Placebo | 22/605 | 3.6
 | Borderline to High (≥100 mg/dL and <126 mg/dL to ≥126 mg/dL) | Aripiprazole | 31/176 | 17.6
 | Borderline to High (≥100 mg/dL and <126 mg/dL to ≥126 mg/dL) | Placebo | 13/142 | 9.2

At 24 weeks, the mean change in fasting glucose in aripiprazole-treated patients was not significantly different than in placebo-treated patients [+2.2 mg/dL (n=42) and +9.6 mg/dL (n=28), respectively].

The mean change in fasting glucose in adjunctive aripiprazole-treated patients with major depressive disorder (+0.7 mg/dL; median exposure 42 days; N=241) was not significantly different than in placebo-treated patients (+0.8 mg/dL; median exposure 42 days; N=246). Table 5 shows the proportion of adult patients with changes in fasting glucose levels from two placebo-controlled, adjunctive trials (median exposure 42 days) in patients with major depressive disorder.

Table 5: Changes in Fasting Glucose from Placebo-Controlled Adjunctive Trials in Adult Patients with Major Depressive Disorder
 | Category Change (at least once) from Baseline | Treatment Arm | n/N | %
Fasting Glucose | Normal to High (<100 mg/dL to ≥126 mg/dL) | Aripiprazole | 2/201 | 1.0
Fasting Glucose | Normal to High (<100 mg/dL to ≥126 mg/dL) | Placebo | 2/204 | 1.0
 | Borderline to High (≥100 mg/dL and <126 mg/dL to ≥126 mg/dL) | Aripiprazole | 4/34 | 11.8
 | Borderline to High (≥100 mg/dL and <126 mg/dL to ≥126 mg/dL) | Placebo | 3/37 | 8.1

Dyslipidemia

Undesirable alterations in lipids have been observed in patients treated with atypical antipsychotics.

Analyses of patients with at least 12 or 24 weeks of exposure were limited by small numbers of patients. Table 6 shows the proportion of adult patients, primarily from pooled schizophrenia and bipolar disorder monotherapy placebo-controlled trials, with changes in total cholesterol (pooled from 17 trials; median exposure 21 to 25 days), fasting triglycerides (pooled from eight trials; median exposure 42 days), fasting LDL cholesterol (pooled from eight trials; median exposure 39 to 45 days, except for placebo-treated patients with baseline normal fasting LDL measurements, who had median treatment exposure of 24 days) and HDL cholesterol (pooled from nine trials; median exposure 40 to 42 days).

Table 6: Changes in Blood Lipid Parameters from Placebo-Controlled Monotherapy Trials in Adults (Primarily Schizophrenia and Bipolar Disorder)
 | Treatment Arm | n/N | %
Total Cholesterol Normal to High (<200 mg/dL to ≥240 mg/dL) | Aripiprazole | 34/1357 | 2.5
Total Cholesterol Normal to High (<200 mg/dL to ≥240 mg/dL) | Placebo | 27/973 | 2.8
Fasting Triglycerides Normal to High (<150 mg/dL to ≥200 mg/dL) | Aripiprazole | 40/539 | 7.4
Fasting Triglycerides Normal to High (<150 mg/dL to ≥200 mg/dL) | Placebo | 30/431 | 7.0
Fasting LDL Cholesterol Normal to High (<100 mg/dL to ≥160 mg/dL) | Aripiprazole | 2/332 | 0.6
Fasting LDL Cholesterol Normal to High (<100 mg/dL to ≥160 mg/dL) | Placebo | 2/268 | 0.7
HDL Cholesterol Normal to Low (≥40 mg/dL to <40 mg/dL) | Aripiprazole | 121/1066 | 11.4
HDL Cholesterol Normal to Low (≥40 mg/dL to <40 mg/dL) | Placebo | 99/794 | 12.5

In monotherapy trials in adults, the proportion of patients at 12 weeks and 24 weeks with changes from normal to high in total cholesterol (fasting/nonfasting), fasting triglycerides, and fasting LDL cholesterol were similar between aripiprazole- and placebo-treated patients: at 12 weeks, total cholesterol (fasting/nonfasting), 1/71 (1.4%) vs. 3/74 (4.1%); fasting triglycerides, 8/62 (12.9%) vs. 5/37 (13.5%); fasting LDL cholesterol, 0/34 (0%) vs. 1/25 (4.0%), respectively; and at 24 weeks, total cholesterol (fasting/nonfasting), 1/42 (2.4%) vs. 3/37 (8.1%); fasting triglycerides, 5/34 (14.7%) vs. 5/20 (25%); fasting LDL cholesterol, 0/22 (0%) vs. 1/18 (5.6%), respectively.

Table 7 shows the proportion of patients with changes in total cholesterol (fasting/nonfasting), fasting triglycerides, fasting LDL cholesterol, and HDL cholesterol from two placebo-controlled adjunctive trials in adult patients with major depressive disorder (median exposure 42 days).

Table 7: Changes in Blood Lipid Parameters from Placebo-Controlled Adjunctive Trials in Adult Patients with Major Depressive Disorder
 | Treatment Arm | n/N | %
Total Cholesterol Normal to High (<200 mg/dL to ≥240 mg/dL) | Aripiprazole | 3/139 | 2.2
Total Cholesterol Normal to High (<200 mg/dL to ≥240 mg/dL) | Placebo | 7/135 | 5.2
Fasting Triglycerides Normal to High (<150 mg/dL to ≥200 mg/dL) | Aripiprazole | 14/145 | 9.7
Fasting Triglycerides Normal to High (<150 mg/dL to ≥200 mg/dL) | Placebo | 6/147 | 4.1
Fasting LDL Cholesterol Normal to High (<100 mg/dL to ≥160 mg/dL) | Aripiprazole | 0/54 | 0
Fasting LDL Cholesterol Normal to High (<100 mg/dL to ≥160 mg/dL) | Placebo | 0/73 | 0
HDL Cholesterol Normal to Low (≥40 mg/dL to <40 mg/dL) | Aripiprazole | 17/318 | 5.3
HDL Cholesterol Normal to Low (≥40 mg/dL to <40 mg/dL) | Placebo | 10/286 | 3.5

Weight Gain

Weight gain has been observed with atypical antipsychotic use. Clinical monitoring of weight is recommended.

In an analysis of 13 placebo-controlled monotherapy trials, primarily from pooled schizophrenia and bipolar disorder, with a median exposure of 21 to 25 days, the mean change in body weight in aripiprazole-treated patients was +0.3 kg (N=1,673) compared to –0.1 kg (N=1,100) in placebo-controlled patients. At 24 weeks, the mean change from baseline in body weight in aripiprazole-treated patients was –1.5 kg (n=73) compared to –0.2 kg (n=46) in placebo-treated patients.

In the trials adding aripiprazole to antidepressants, patients first received 8 weeks of antidepressant treatment followed by 6 weeks of adjunctive aripiprazole or placebo in addition to their ongoing antidepressant treatment. The mean change in body weight in patients receiving adjunctive aripiprazole was +1.7 kg (N=347) compared to +0.4 kg (N=330) in patients receiving adjunctive placebo.

Table 8 shows the percentage of adult patients with weight gain ≥7% of body weight by indication.

Table 8: Percentage of Patients From Placebo-Controlled Trials in Adult Patients with Weight Gain ≥7% of Body Weight
Weight gain ≥7% of body weight | Indication | Treatment Arm | N | Patients n (%)
 | Schizophrenia [4 to 6 weeks duration.] | Aripiprazole | 852 | 69 (8.1)
 | Schizophrenia [4 to 6 weeks duration.] | Placebo | 379 | 12 (3.2)
 | Bipolar Mania [3 weeks duration.] | Aripiprazole | 719 | 16 (2.2)
 | Bipolar Mania [3 weeks duration.] | Placebo | 598 | 16 (2.7)
 | Major Depressive Disorder (Adjunctive Therapy) [6 weeks duration.] | Aripiprazole | 347 | 18 (5.2)
 | Major Depressive Disorder (Adjunctive Therapy) [6 weeks duration.] | Placebo | 330 | 2 (0.6)

5.7 Pathological Gambling and Other Compulsive Behaviors

Postmarketing case reports suggest that patients can experience intense urges, particularly for gambling, and the inability to control these urges while taking aripiprazole. Other compulsive urges, reported less frequently, include: sexual urges, shopping, eating or binge eating, and other impulsive or compulsive behaviors. Because patients may not recognize these behaviors as abnormal, it is important for prescribers to ask patients or their caregivers specifically about the development of new or intense gambling urges, compulsive sexual urges, compulsive shopping, binge or compulsive eating, or other urges while being treated with ABILIFY MYCITE. It should be noted that impulse-control symptoms can be associated with the underlying disorder. In some cases, although not all, urges were reported to have stopped when the dose was reduced or the medication was discontinued. Compulsive behaviors may result in harm to the patient and others if not recognized. Consider dose reduction or stopping the medication if a patient develops such urges.

5.8 Orthostatic Hypotension

ABILIFY MYCITE may cause orthostatic hypotension, perhaps due to its α1-adrenergic receptor antagonism. The incidence of orthostatic hypotension-associated events from short-term, placebo-controlled trials of adult patients on oral aripiprazole (n=2467) included (aripiprazole incidence, placebo incidence) orthostatic hypotension (1%, 0.3%), postural dizziness (0.5%, 0.3%), and syncope (0.5%, 0.4%) [see Adverse Reactions (6.1)].

The incidence of a significant orthostatic change in blood pressure (defined as a decrease in systolic blood pressure ≥20 mmHg accompanied by an increase in heart rate ≥25 bpm when comparing standing to supine values) for aripiprazole was not meaningfully different from placebo (aripiprazole incidence, placebo incidence) in adult oral aripiprazole-treated patients (4%, 2%).

ABILIFY MYCITE should be used with caution in patients with known cardiovascular disease (history of myocardial infarction or ischemic heart disease, heart failure or conduction abnormalities), cerebrovascular disease, or conditions which would predispose patients to hypotension (dehydration, hypovolemia, and treatment with antihypertensive medications) [see Drug Interactions (7.1)].

5.9 Falls

Antipsychotics, including ABILIFY MYCITE, may cause somnolence, postural hypotension, motor and sensory instability, which may lead to falls and, consequently, fractures or other injuries. For patients with diseases, conditions, or medications that could exacerbate these effects, complete fall risk assessments when initiating antipsychotic treatment and recurrently for patients on long-term antipsychotic therapy.

5.10 Leukopenia, Neutropenia, and Agranulocytosis

In clinical trials and/or postmarketing experience, events of leukopenia and neutropenia have been reported temporally related to antipsychotic agents, including aripiprazole. Agranulocytosis has also been reported.

Possible risk factors for leukopenia/neutropenia include pre-existing low white blood cell count (WBC)/absolute neutrophil count (ANC) and history of drug-induced leukopenia/neutropenia. In patients with a history of a clinically significant low WBC/ANC or drug-induced leukopenia/neutropenia, perform a complete blood count (CBC) frequently during the first few months of therapy. In such patients, consider discontinuation of ABILIFY MYCITE at the first sign of a clinically significant decline in WBC in the absence of other causative factors.

Monitor patients with clinically significant neutropenia for fever or other symptoms or signs of infection and treat promptly if such symptoms or signs occur. Discontinue ABILIFY MYCITE in patients with severe neutropenia (absolute neutrophil count <1,000/mm^3) and follow their WBC counts until recovery.

5.11 Seizures

In short-term, placebo-controlled trials, patients with a history of seizures excluded seizures/convulsions occurred in 0.1% (3/2,467) of undiagnosed adult patients treated with oral aripiprazole.

As with other antipsychotic drugs, ABILIFY MYCITE should be used cautiously in patients with a history of seizures or with conditions that lower the seizure threshold. Conditions that lower the seizure threshold may be more prevalent in a population of 65 years or older.

5.12 Potential for Cognitive and Motor Impairment

ABILIFY MYCITE, like other antipsychotics, has the potential to impair judgment, thinking, or motor skills. In short-term, placebo-controlled trials, somnolence (including sedation) was reported in 11% of aripiprazole-treated patients compared with 6% of placebo-treated patients. Somnolence (including sedation) led to discontinuation in 0.3% (8/2,467) of adult patients on oral aripiprazole in short-term, placebo-controlled trials.

Patients should be cautioned about operating hazardous machinery, including automobiles, until they are reasonably certain that therapy with ABILIFY MYCITE does not affect them adversely.

5.13 Body Temperature Regulation

Disruption of the body's ability to reduce core body temperature has been attributed to antipsychotic agents. Appropriate care is advised when prescribing ABILIFY MYCITE for patients who will be experiencing conditions which may contribute to an elevation in core body temperature (e.g., exercising strenuously, exposure to extreme heat, receiving concomitant medication with anticholinergic activity, or being subject to dehydration).

5.14 Dysphagia

Esophageal dysmotility and aspiration have been associated with antipsychotic drug use, including aripiprazole. ABILIFY MYCITE and other antipsychotic drugs should be used cautiously in patients at risk for aspiration pneumonia.

6 ADVERSE REACTIONS

The following adverse reactions are discussed in more detail in other sections of the labeling:

- Increased Mortality in Elderly Patients with Dementia-Related Psychosis [see Boxed Warning and Warnings and Precautions (5.1)]
- Suicidal Thoughts and Behaviors in Pediatric and Young Adult Patients [see Boxed Warning and Warnings and Precautions (5.2)]
- Cerebrovascular Adverse Events, Including Stroke [see Warnings and Precautions (5.3)]
- Neuroleptic Malignant Syndrome (NMS) [see Warnings and Precautions (5.4)]
- Tardive Dyskinesia [see Warnings and Precautions (5.5)]
- Metabolic Changes [see Warnings and Precautions (5.6)]
- Pathological Gambling and Other Compulsive Behaviors [see Warnings and Precautions (5.7)]
- Orthostatic Hypotension [see Warnings and Precautions (5.8)]
- Falls [see Warnings and Precautions (5.9)]
- Leukopenia, Neutropenia, and Agranulocytosis [see Warnings and Precautions (5.10)]
- Seizures [see Warnings and Precautions (5.11)]
- Potential for Cognitive and Motor Impairment [see Warnings and Precautions (5.12)]
- Body Temperature Regulation [see Warnings and Precautions (5.13)]
- Dysphagia [see Warnings and Precautions (5.14)]

6.1 Clinical Trials Experience

Because clinical trials are conducted under widely varying conditions, adverse reaction rates observed in the clinical trials of a drug cannot be directly compared to rates in the clinical trials of another drug and may not reflect the rates observed in practice.

The safety of ABILIFY MYCITE for the treatment of adults with schizophrenia, treatment of adults with manic and mixed episodes associated with bipolar I disorder, and adjunctive treatment of adults with major depressive disorder (MDD) has been established and is based on trials of aripiprazole including 13,543 adult patients who participated in multiple-dose clinical trials in schizophrenia, bipolar disorder, major depressive disorder, and other disorders, and who had approximately 7,619 patient-years of exposure to oral aripiprazole. A total of 3,390 patients were treated with oral aripiprazole for at least 180 days and 1,933 patients treated with oral aripiprazole had at least one year of exposure.

The conditions and duration of treatment with aripiprazole (monotherapy and adjunctive therapy with antidepressants or mood stabilizers) included (in overlapping categories) double-blind, comparative and noncomparative open-label studies, inpatient and outpatient studies, fixed- and flexible-dose studies, and short- and longer-term exposure.

The most common adverse reactions of aripiprazole in adult patients in clinical trials (≥10%) were nausea, vomiting, constipation, headache, dizziness, akathisia, anxiety, insomnia, and restlessness.

Adverse Reactions in Adult Patients with Schizophrenia

The following findings are based on a pool of five placebo-controlled trials (four 4-week and one 6-week) in which oral aripiprazole was administered in doses ranging from 2 to 30 mg/day.

The commonly observed adverse reaction associated with the use of aripiprazole tablets in patients with schizophrenia (incidence of 5% or greater and aripiprazole tablets incidence at least twice that for placebo) was akathisia (aripiprazole tablets 8%; placebo 4%).

Adverse Reactions in Adult Patients with Bipolar Mania

Adult Patients Who Received Monotherapy

The following findings are based on a pool of 3-week, placebo-controlled bipolar mania trials in which oral aripiprazole was administered at doses of 15 or 30 mg/day.

Commonly observed adverse reactions associated with the use of aripiprazole tablets in patients with bipolar mania (incidence of 5% or greater and aripiprazole tablets incidence at least twice that for placebo) are shown in Table 9.

Table 9: Commonly Observed Adverse Reactions in Short-Term, Placebo-Controlled Trials of Adult Patients with Bipolar Mania Treated with Oral Aripiprazole Monotherapy
Preferred Term | Percentage of Patients Reporting Reaction
 | Aripiprazole tablets (n=917) | Placebo (n=753)
Akathisia | 13 | 4
Sedation | 8 | 3
Restlessness | 6 | 3
Tremor | 6 | 3
Extrapyramidal Disorder | 5 | 2

Table 10 enumerates the pooled incidence, rounded to the nearest percent, of adverse reactions that occurred during acute therapy (up to 6 weeks in schizophrenia and up to 3 weeks in bipolar mania), including only those reactions that occurred in 2% or more of patients treated with aripiprazole tablets (doses ≥2 mg/day) and for which the incidence in patients treated with aripiprazole tablets was greater than the incidence in patients treated with placebo in the combined dataset.

Table 10: Adverse Reactions in Short-Term, Placebo-Controlled Trials in Adult Patients Treated with Oral Aripiprazole
System Organ Class Preferred Term | Percentage of Patients Reporting Reaction [Adverse reactions reported by at least 2% of patients treated with oral aripiprazole, except adverse reactions which had an incidence equal to or less than placebo]
 | Aripiprazole tablets (n=1843) | Placebo (n=1166)
Eye Disorders
Blurred Vision | 3 | 1
Gastrointestinal Disorders
Nausea | 15 | 11
Constipation | 11 | 7
Vomiting | 11 | 6
Dyspepsia | 9 | 7
Dry Mouth | 5 | 4
Toothache | 4 | 3
Abdominal Discomfort | 3 | 2
Stomach Discomfort | 3 | 2
General Disorders and Administration Site Conditions
Fatigue | 6 | 4
Pain | 3 | 2
Musculoskeletal and Connective Tissue Disorders
Musculoskeletal Stiffness | 4 | 3
Pain in Extremity | 4 | 2
Myalgia | 2 | 1
Muscle Spasms | 2 | 1
Nervous System Disorders
Headache | 27 | 23
Dizziness | 10 | 7
Akathisia | 10 | 4
Sedation | 7 | 4
Extrapyramidal Disorder | 5 | 3
Tremor | 5 | 3
Somnolence | 5 | 3
Psychiatric Disorders
Agitation | 19 | 17
Insomnia | 18 | 13
Anxiety | 17 | 13
Restlessness | 5 | 3
Respiratory, Thoracic, and Mediastinal Disorders
Pharyngolaryngeal Pain | 3 | 2
Cough | 3 | 2

An examination of population subgroups did not reveal any clear evidence of differential adverse reaction incidence on the basis of age, gender, or race.

Adult Patients with Adjunctive Therapy with Bipolar Mania

The following findings are based on a placebo-controlled trial of adult patients with bipolar disorder in which aripiprazole tablets was administered at doses of 15 or 30 mg/day as adjunctive therapy with lithium or valproate.

In a study of patients who were already tolerating either lithium or valproate as monotherapy, discontinuation rates due to adverse reactions were 12% for patients treated with adjunctive aripiprazole tablets compared to 6% for patients treated with adjunctive placebo. The most common adverse drug reactions associated with discontinuation in the adjunctive aripiprazole-treated compared to placebo-treated patients were akathisia (5% and 1%, respectively) and tremor (2% and 1%, respectively).

The commonly observed adverse reactions associated with adjunctive aripiprazole tablets and lithium or valproate in patients with bipolar mania (incidence of 5% or greater and incidence at least twice that for adjunctive placebo) were: akathisia, insomnia, and extrapyramidal disorder.

Table 11 enumerates the incidence, rounded to the nearest percent, of adverse reactions that occurred during acute treatment (up to 6 weeks), including only those reactions that occurred in 2% or more of patients treated with adjunctive aripiprazole tablets (doses of 15 or 30 mg/day) and lithium or valproate and for which the incidence in patients treated with this combination was greater than the incidence in patients treated with placebo plus lithium or valproate.

Table 11: Adverse Reactions in a Short-Term, Placebo-Controlled Trial of Adjunctive Therapy in Patients with Bipolar Disorder
System Organ Class Preferred Term | Percentage of Patients Reporting Reaction [Adverse reactions reported by at least 2% of patients treated with oral aripiprazole, except adverse reactions which had an incidence equal to or less than placebo]
 | Aripiprazole tablets + Li or Val [Lithium or Valproate] (n=253) | Placebo + Li or Val (n=130)
Gastrointestinal Disorders
Nausea | 8 | 5
Vomiting | 4 | 0
Salivary Hypersecretion | 4 | 2
Dry Mouth | 2 | 1
Infections and Infestations
Nasopharyngitis | 3 | 2
Investigations
Weight Increased | 2 | 1
Nervous System Disorders
Akathisia | 19 | 5
Tremor | 9 | 6
Extrapyramidal Disorder | 5 | 1
Dizziness | 4 | 1
Sedation | 4 | 2
Psychiatric Disorders
Insomnia | 8 | 4
Anxiety | 4 | 1
Restlessness | 2 | 1

Adult Patients Receiving Aripiprazole Tablets as Adjunctive Treatment of Major Depressive Disorder

The following findings are based on a pool of two placebo-controlled trials of patients with major depressive disorder in which aripiprazole tablets were administered at doses of 2 mg to 20 mg as adjunctive treatment to continued antidepressant therapy.

The incidence of discontinuation due to adverse reactions was 6% for adjunctive aripiprazole-treated patients and 2% for adjunctive placebo-treated patients.

The commonly observed adverse reactions associated with the use of adjunctive aripiprazole tablets in patients with major depressive disorder (incidence of 5% or greater and aripiprazole tablets incidence at least twice that for placebo) were: akathisia, restlessness, insomnia, constipation, fatigue, and blurred vision.

Table 12 enumerates the pooled incidence, rounded to the nearest percent, of adverse reactions that occurred during acute therapy (up to 6 weeks), including only those adverse reactions that occurred in 2% or more of patients treated with adjunctive aripiprazole tablets (doses ≥2 mg/day) and for which the incidence in patients treated with adjunctive aripiprazole tablets was greater than the incidence in patients treated with adjunctive placebo in the combined dataset.

Table 12: Adverse Reactions in Short-Term, Placebo-Controlled Adjunctive Trials in Patients with Major Depressive Disorder
System Organ Class Preferred Term | Percentage of Patients Reporting Reaction [Adverse reactions reported by at least 2% of patients treated with adjunctive aripiprazole tablets, except adverse reactions which had an incidence equal to or less than placebo]
 | Aripiprazole tablets + ADT [Antidepressant Therapy] (n=371) | Placebo + ADT (n=366)
Eye Disorders
Blurred Vision | 6 | 1
Gastrointestinal Disorders
Constipation | 5 | 2
General Disorders and Administration Site Conditions
Fatigue | 8 | 4
Feeling Jittery | 3 | 1
Infections and Infestations
Upper Respiratory Tract Infection | 6 | 4
Investigations
Weight Increased | 3 | 2
Metabolism and Nutrition Disorders
Increased Appetite | 3 | 2
Musculoskeletal and Connective Tissue Disorders
Arthralgia | 4 | 3
Myalgia | 3 | 1
Nervous System Disorders
Akathisia | 25 | 4
Somnolence | 6 | 4
Tremor | 5 | 4
Sedation | 4 | 2
Dizziness | 4 | 2
Disturbance in Attention | 3 | 1
Extrapyramidal Disorder | 2 | 0
Psychiatric Disorders
Restlessness | 12 | 2
Insomnia | 8 | 2

Dose-Related Adverse Reactions in Patients with Schizophrenia

Dose response relationships for the incidence of treatment-emergent adverse events were evaluated from four trials in adult patients with schizophrenia comparing various fixed doses (2, 5, 10, 15, 20, and 30 mg/day) of oral aripiprazole to placebo. This analysis, stratified by study, indicated that the only adverse reaction to have a possible dose response relationship, and then most prominent only with 30 mg, was somnolence [including sedation]; (incidences were placebo, 7.1%; 10 mg, 8.5%; 15 mg, 8.7%; 20 mg, 7.5%; 30 mg, 12.6%).

Extrapyramidal Symptoms

Schizophrenia

In short-term, placebo-controlled trials in schizophrenia in adults, the incidence of reported EPS-related events, excluding events related to akathisia, for aripiprazole-treated patients was 13% vs. 12% for placebo; and the incidence of akathisia-related events for aripiprazole-treated patients was 8% vs. 4% for placebo.

Objectively collected data from those trials was collected on the Simpson Angus Rating Scale (for EPS), the Barnes Akathisia Scale (for akathisia), and the Assessments of Involuntary Movement Scales (for dyskinesias). In the adult schizophrenia trials, the objectively collected data did not show a difference between aripiprazole tablets and placebo, with the exception of the Barnes Akathisia Scale (aripiprazole tablets, 0.08; placebo, –0.05).

Similarly, in a long-term (26-week), placebo-controlled trial of schizophrenia in adults, objectively collected data on the Simpson Angus Rating Scale (for EPS), the Barnes Akathisia Scale (for akathisia), and the Assessments of Involuntary Movement Scales (for dyskinesias) did not show a difference between aripiprazole tablets and placebo.

Bipolar Mania

In the short-term, placebo-controlled trials in bipolar mania in adults, the incidence of reported EPS-related events, excluding events related to akathisia, for monotherapy aripiprazole-treated patients was 16% vs. 8% for placebo and the incidence of akathisia-related events for monotherapy aripiprazole-treated patients was 13% vs. 4% for placebo. In the 6-week placebo-controlled trial in bipolar mania for adjunctive therapy with lithium or valproate, the incidence of reported EPS-related events, excluding events related to akathisia for adjunctive aripiprazole-treated patients was 15% vs. 8% for adjunctive placebo and the incidence of akathisia-related events for adjunctive aripiprazole-treated patients was 19% vs. 5% for adjunctive placebo.

In the adult bipolar mania trials with monotherapy aripiprazole tablets, the Simpson Angus Rating Scale and the Barnes Akathisia Scale showed a significant difference between aripiprazole tablets and placebo (aripiprazole tablets, 0.50; placebo, –0.01 and aripiprazole tablets, 0.21; placebo, –0.05). Changes in the Assessments of Involuntary Movement Scales were similar for the aripiprazole tablets and placebo groups. In the bipolar mania trials with aripiprazole tablets as adjunctive therapy with either lithium or valproate, the Simpson Angus Rating Scale and the Barnes Akathisia Scale showed a significant difference between adjunctive aripiprazole tablets and adjunctive placebo (aripiprazole tablets, 0.73; placebo, 0.07 and aripiprazole tablets, 0.30; placebo, 0.11). Changes in the Assessments of Involuntary Movement Scales were similar for adjunctive aripiprazole tablets and adjunctive placebo.

Major Depressive Disorder

In the short-term, placebo-controlled trials in major depressive disorder, the incidence of reported EPS-related events, excluding events related to akathisia, for adjunctive aripiprazole-treated patients was 8% vs. 5% for adjunctive placebo-treated patients; and the incidence of akathisia-related events for adjunctive aripiprazole-treated patients was 25% vs. 4% for adjunctive placebo-treated patients.

In the major depressive disorder trials, the Simpson Angus Rating Scale and the Barnes Akathisia Scale showed a significant difference between adjunctive aripiprazole tablets and adjunctive placebo (aripiprazole tablets, 0.31; placebo, 0.03 and aripiprazole tablets, 0.22; placebo, 0.02). Changes in the Assessments of Involuntary Movement Scales were similar for the adjunctive aripiprazole tablets and adjunctive placebo groups.

Dystonia

Symptoms of dystonia, prolonged abnormal contractions of muscle groups, may occur in susceptible individuals during the first few days of treatment. Dystonic symptoms include: spasm of the neck muscles, sometimes progressing to tightness of the throat, swallowing difficulty, difficulty breathing, and/or protrusion of the tongue. While these symptoms can occur at low doses, they occur more frequently and with greater severity with high potency and at higher doses of first generation antipsychotic drugs. An elevated risk of acute dystonia is observed in males and younger age groups.

Skin Irritation for MYCITE Patch

Symptoms of skin irritation localized at the site of the MYCITE Patch may occur in some patients. In clinical studies with the 1-component patch, sixty-one patients (12.4%) experienced skin rashes localized at the site of patch placement.

Adverse Reactions in Long-Term, Double-Blind, Placebo-Controlled Trials

The adverse reactions reported in a 26-week, double-blind trial comparing oral aripiprazole and placebo in patients with schizophrenia were generally consistent with those reported in the short-term, placebo-controlled trials, except for a higher incidence of tremor [8% (12/153) for aripiprazole tablets vs. 2% (3/153) for placebo]. In this study, the majority of the cases of tremor were of mild intensity (8/12 mild and 4/12 moderate), occurred early in therapy (9/12 ≤49 days), and were of limited duration (7/12 ≤10 days). Tremor led to discontinuation (<1%) of aripiprazole tablets. In addition, in a long-term (52 weeks), active-controlled study, the incidence of tremor was 5% (40/859) for aripiprazole tablets. A similar profile was observed in a long-term monotherapy study and a long-term adjunctive study with lithium and valproate in bipolar disorder.

Other Adverse Reactions Observed during Clinical Trial Evaluation of Aripiprazole

Other adverse reactions associated with aripiprazole are presented below. The listing does not include reactions: 1) already listed in previous tables or elsewhere in labeling, 2) for which a drug cause was remote, 3) which were so general as to be uninformative, 4) which were not considered to have significant clinical implications, or 5) which occurred at a rate equal to or less than placebo.

Reactions are categorized by body system according to the following definitions: frequent adverse reactions are those occurring in at least 1/100 patients; infrequent adverse reactions are those occurring in 1/100 to 1/1000 patients; rare reactions are those occurring in fewer than 1/1000 patients:

- Blood and Lymphatic System Disorders: rare - thrombocytopenia
- Cardiac Disorders: infrequent – bradycardia, palpitations, rare – atrial flutter, cardio-respiratory arrest, atrioventricular block, atrial fibrillation, angina pectoris, myocardial ischemia, myocardial infarction, cardiopulmonary failure
- Eye Disorders: infrequent – photophobia; rare - diplopia
- Gastrointestinal Disorders: infrequent - gastroesophageal reflux disease
- General Disorders and Administration Site Conditions: frequent - asthenia; infrequent – peripheral edema, chest pain; rare – face edema
- Hepatobiliary Disorders: rare - hepatitis, jaundice
- Immune System Disorders: rare- hypersensitivity
- Injury, Poisoning, and Procedural Complications: infrequent – fall; rare – heatstroke
- Investigations: frequent - blood prolactin decreased, weight decreased; infrequent - hepatic enzyme increased, blood glucose increased, blood lactate dehydrogenase increased, gamma glutamyl transferase increased; rare – blood prolactin increased, blood urea increased, blood creatinine increased, blood bilirubin increased, electrocardiogram QT prolonged, glycosylated hemoglobin increased
- Metabolism and Nutrition Disorders: frequent – anorexia; rare - hypokalemia, hyponatremia, hypoglycemia
- Musculoskeletal and Connective Tissue Disorders: infrequent - muscular weakness, muscle tightness; rare – rhabdomyolysis, mobility decreased
- Nervous System Disorders: infrequent - parkinsonism, memory impairment, cogwheel rigidity, hypokinesia, bradykinesia; rare – akinesia, myoclonus, coordination abnormal, speech disorder, grand mal convulsion; <1/10,000 patients - choreoathetosis
- Psychiatric Disorders: infrequent – aggression, loss of libido, delirium; rare – libido increased, anorgasmia, tic, homicidal ideation, catatonia, sleep walking
- Renal and Urinary Disorders: rare - urinary retention, nocturia
- Reproductive System and Breast Disorders: infrequent - erectile dysfunction; rare – gynaecomastia, menstruation irregular, amenorrhea, breast pain, priapism
- Respiratory, Thoracic, and Mediastinal Disorders: infrequent - nasal congestion, dyspnea
- Skin and Subcutaneous Tissue Disorders: infrequent - rash, hyperhidrosis, pruritus, photosensitivity reaction, alopecia; rare - urticaria
- Vascular Disorders: infrequent – hypotension, hypertension

6.2 Postmarketing Experience

The following adverse reactions have been identified during post-approval use of aripiprazole. Because these reactions are reported voluntarily from a population of uncertain size, it is not always possible to reliably estimate their frequency or establish a causal relationship to drug exposure: occurrences of allergic reaction (anaphylactic reaction, angioedema, laryngospasm, pruritus/urticaria, or oropharyngeal spasm), blood glucose fluctuation, Drug Reaction with Eosinophilia and Systemic Symptoms (DRESS), hiccups, oculogyric crisis, pathological gambling, and fecal incontinence.

7 DRUG INTERACTIONS

7.1 Drugs Having Clinically Important Interactions with ABILIFY MYCITE

Table 13 below includes clinically important drug interactions with ABILIFY MYCITE.

Table 13: Clinically Important Drug Interactions with ABILIFY MYCITE
Concomitant Drug Name or Drug Class | Clinical Rationale | Clinical Recommendation
Strong CYP3A4 Inhibitors (e.g., itraconazole, clarithromycin) or strong CYP2D6 inhibitors (e.g., quinidine, fluoxetine, paroxetine) | The concomitant use of aripiprazole with strong CYP3A4 or CYP2D6 inhibitors increased the exposure of aripiprazole compared to the use of aripiprazole alone [see Clinical Pharmacology (12.3)]. | With concomitant use of ABILIFY MYCITE with a strong CYP3A4 inhibitor or CYP2D6 inhibitor, reduce the ABILIFY MYCITE dosage [see Dosage and Administration (2.6)].
Strong CYP3A4 Inducers (e.g., carbamazepine, rifampin) | The concomitant use of aripiprazole and carbamazepine decreased the exposure of aripiprazole compared to the use of aripiprazole alone [see Clinical Pharmacology (12.3)]. | With concomitant use of ABILIFY MYCITE with a strong CYP3A4 inducer, consider increasing the ABILIFY MYCITE dosage [see Dosage and Administration (2.6)].
Antihypertensive Drugs | Due to its alpha adrenergic antagonism, aripiprazole has the potential to enhance the effect of certain antihypertensive agents. | Monitor blood pressure and adjust dose accordingly [see Warnings and Precautions (5.8)].
Benzodiazepines (e.g., lorazepam) | The intensity of sedation was greater with the combination of oral aripiprazole and lorazepam as compared to that observed with aripiprazole alone. The orthostatic hypotension observed was greater with the combination as compared to that observed with lorazepam alone [see Warnings and Precautions (5.8)] | Monitor sedation and blood pressure. Adjust dose accordingly.

7.2 Drugs Having No Clinically Important Interactions with ABILIFY MYCITE

Based on pharmacokinetic studies, no dosage adjustment of ABILIFY MYCITE is required when administered concomitantly with famotidine, valproate, lithium, lorazepam.

In addition, no dosage adjustment is necessary for substrates of CYP2D6 (e.g., dextromethorphan, fluoxetine, paroxetine, or venlafaxine), CYP2C9 (e.g., warfarin), CYP2C19 (e.g., omeprazole, warfarin, escitalopram), or CYP3A4 (e.g., dextromethorphan) when co-administered with ABILIFY MYCITE. Additionally, no dosage adjustment is necessary for valproate, lithium, lamotrigine, lorazepam, or sertraline when co-administered with ABILIFY MYCITE [see Clinical Pharmacology (12.3)].

8 USE IN SPECIFIC POPULATIONS

8.1 Pregnancy

Pregnancy Exposure Registry

There is a pregnancy exposure registry that monitors pregnancy outcomes in women exposed to ABILIFY MYCITE during pregnancy. For more information contact the National Pregnancy Registry for Atypical Antipsychotics at 1-866-961-2388 or visit http://womensmentalhealth.org/clinical-and-research-programs/pregnancyregistry/.

Risk Summary

Neonates exposed to antipsychotic drugs, including ABILIFY MYCITE, during the third trimester of pregnancy are at risk for extrapyramidal and/or withdrawal symptoms [see Clinical Considerations]. Overall available data from published epidemiologic studies of pregnant women exposed to aripiprazole have not established a drug-associated risk of major birth defects, miscarriage, or adverse maternal outcomes. There are risks to the mother associated with untreated schizophrenia, bipolar I disorder, or major depressive disorder, and with exposure to antipsychotics, including ABILIFY MYCITE, during pregnancy (see Clinical Considerations). Aripiprazole exposure during pregnancy may decrease milk supply in the post-partum period [see Use in Specific Populations (8.2)].

Animal reproduction studies were conducted with aripiprazole in rats and rabbits during organogenesis, and in rats during the pre-and post-natal period. Oral and intravenous aripiprazole administration during organogenesis in rats and/or rabbits at doses higher than the maximum recommended human dose (MRHD) produced fetal death, decreased fetal weight, undescended testicles, delayed skeletal ossification, skeletal abnormalities, and diaphragmatic hernia. Oral and intravenous aripiprazole administration during the pre- and post-natal period in rats at doses higher than the MRHD produced prolonged gestation, stillbirths, decreased pup weight, and decreased pup survival.

The background risk of major birth defects and miscarriage for the indicated population are unknown. All pregnancies have a background risk of birth defect, loss, or other adverse outcomes. In the U.S. general population, the estimated background risk of major birth defects and miscarriage in clinically recognized pregnancies is 2 to 4% and 15 to 20%, respectively.

Clinical Considerations

Disease-associated maternal and/or embryo/fetal risk

There is a risk to the mother from untreated schizophrenia or bipolar I disorder, including increased risk of relapse, hospitalization, and suicide. Schizophrenia and bipolar I disorder are associated with increased adverse perinatal outcomes, including preterm birth. It is not known if this is a direct result of the illness or other comorbid factors.

A prospective, longitudinal study followed 201 pregnant women with a history of major depressive disorder who were euthymic and taking antidepressants at the beginning of pregnancy. The women who discontinued antidepressants during pregnancy were more likely to experience a relapse of major depression than women who continued antidepressants.

Consider the risk of untreated depression when discontinuing or changing treatment with antidepressant medication during pregnancy and postpartum.

Fetal/Neonatal Adverse Reactions

Extrapyramidal and/or withdrawal symptoms, including agitation, hypertonia, hypotonia, tremor, somnolence, respiratory distress and feeding disorder have been reported in neonates who were exposed to antipsychotic drugs (including aripiprazole) during the third trimester of pregnancy. These symptoms have varied in severity. Some neonates recovered within hours or days without specific treatment; others required prolonged hospitalization. Monitor neonates for extrapyramidal and/or withdrawal symptoms.

Data

Animal Data

In animal studies, aripiprazole demonstrated developmental toxicity, including possible teratogenic effects in rats and rabbits.

Pregnant rats were treated with oral doses of 3, 10, and 30 mg/kg/day (1, 3, and 10 times the MRHD on mg/m^2 basis) of aripiprazole during the period of organogenesis. Gestation was slightly prolonged at 30 mg/kg/day. Treatment at the high dose of 30 mg/kg/day caused a slight delay in fetal development (decreased fetal weight), undescended testes, and delayed skeletal ossification (also seen at 10 mg/kg/day). There were no adverse effects on embryofetal or pup survival. Delivered offspring had decreased body weights (10 and 30 mg/kg/day) and increased incidences of hepatodiaphragmatic nodules and diaphragmatic hernia at 30 mg/kg (the other dose groups were not examined for these findings). Postnatally, delayed vaginal opening was seen at 10 and 30 mg/kg/day and impaired reproductive performance (decreased fertility rate, corpora lutea, implants, live fetuses, and increased post-implantation loss, likely mediated through effects on female offspring) was seen at 30 mg/kg/day. Some maternal toxicity was seen at 30 mg/kg/day however, there was no evidence to suggest that these developmental effects were secondary to maternal toxicity.

In pregnant rats receiving aripiprazole injection intravenously (3, 9, and 27 mg/kg/day) during the period of organogenesis, decreased fetal weight and delayed skeletal ossification were seen at the highest dose where it also caused maternal toxicity.

Pregnant rabbits were treated with oral doses of 10, 30, and 100 mg/kg/day (2 , 3, and 11 times human exposure at MRHD based on AUC and 6, 19, and 65 times the MRHD based on mg/m^2) of aripiprazole during the period of organogenesis. At the high dose of 100 mg/kg/day decreased maternal food consumption, and increased abortions were seen as well as increased fetal mortality, decreased fetal weight (also seen at 30 mg/kg/day), increased incidence of a skeletal abnormality (fused sternebrae) (also seen at 30 mg/kg/day).

In pregnant rabbits receiving aripiprazole injection intravenously (3, 10, and 30 mg/kg/day) during the period of organogenesis, the highest dose, which caused pronounced maternal toxicity, resulted in decreased fetal weight, increased fetal abnormalities (primarily skeletal), and decreased fetal skeletal ossification. The fetal no-effect dose was 10 mg/kg/day, which is 5 times the human exposure at the MRHD based on AUC and is 6 times the MRHD based on mg/m^2.

In a study in which rats were treated peri- and post-natally with oral doses of 3, 10, and 30 mg/kg/day (1, 3, and 10 times the MRHD on mg/m^2 basis) of aripiprazole from gestation Day 17 through Day 21 postpartum, slight maternal toxicity, slightly prolonged gestation an increase in stillbirths and decreases in pup weight (persisting into adulthood) and survival were seen at 30 mg/kg/day.

In rats receiving aripiprazole injection intravenously (3, 8, and 20 mg/kg/day) from gestation Day 6 through Day 20 postpartum, an increase in stillbirths was seen at 8 and 20 mg/kg/day, and decreases in early postnatal pup weights and survival were seen at 20 mg/kg/day; these effects were seen in presence of maternal toxicity. There were no effects on postnatal behavioral and reproductive development.

The effect of ABILIFY MYCITE on labor and delivery in humans is unknown.

8.2 Lactation

Risk Summary

Aripiprazole is present in human breast milk. Based on published case reports and pharmacovigilance reports, aripiprazole exposure during pregnancy and/or the postpartum period may lead to clinically relevant decreases in milk supply which may be reversible with discontinuation of the drug. There are also reports of aripiprazole exposure during pregnancy and no maternal milk supply in the post-partum period. Effects on milk supply may be mediated through decreases in prolactin levels, which have been observed [see Adverse Reactions (6.1)]. Monitor the breastfed infant for dehydration and lack of appropriate weight gain. The developmental and health benefits of breastfeeding should be considered along with the mother's clinical need for ABILIFY MYCITE and any potential adverse effects on the breastfed infant from ABILIFY MYCITE or from the underlying maternal condition.

8.4 Pediatric Use

Safety and effectiveness of ABILIFY MYCITE in pediatric patients have not been established.

Antidepressants increased the risk of suicidal thoughts and behaviors in pediatric patients [see Boxed Warning,and Warnings and Precautions (5.2)].

8.5 Geriatric Use

No dosage adjustment of ABILIFY MYCITE is recommended for elderly patients for the approved indications [see Boxed Warning, Warnings and Precautions (5.1) and Clinical Pharmacology (12.3)].

Of the 13,543 patients treated with oral aripiprazole in clinical trials, 1,073 (8%) were ≥65 years old and 799 (6%) were ≥75 years old. Placebo-controlled studies of oral aripiprazole in schizophrenia, bipolar mania, or major depressive disorder did not include sufficient numbers of patients aged 65 and over to determine whether they respond differently from younger patients.

Elderly patients with dementia-related psychosis treated with antipsychotic drugs are at an increased risk of death. Elderly patients treated with antipsychotic drugs with dementia-related psychosis had a greater incidence of stroke and transient ischemic attack. ABILIFY MYCITE is not approved for the treatment of elderly patients with dementia-related psychosis [see Boxed Warning and Warnings and Precautions (5.1, 5.3)].

8.6 CYP2D6 Poor Metabolizers

ABILIFY MYCITE dosage adjustment is recommended in known CYP2D6 poor metabolizers due to high aripiprazole concentrations. Approximately 8% of Caucasians and 3 to 8% of Black/African Americans cannot metabolize CYP2D6 substrates and are classified as poor metabolizers (PM) [see Dosage and Administration (2.6) and Clinical Pharmacology (12.3)].

8.7 Hepatic and Renal Impairment

RENAL IMPAIRMENT SUBSECTION

No dosage adjustment for ABILIFY MYCITE is required on the basis of a patient's hepatic function (mild to severe hepatic impairment, Child-Pugh score between 5 and 15) or renal function (mild to severe renal impairment, glomerular filtration rate between 15 and 90 mL/minute) [see Clinical Pharmacology (12.3)].

8.8 Other Specific Populations

No dosage adjustment for ABILIFY MYCITE is required on the basis of a patient's sex, race, or smoking status [see Clinical Pharmacology (12.3)].

9 DRUG ABUSE AND DEPENDENCE

9.1 Controlled Substance

ABILIFY MYCITE is not a controlled substance.

9.2 Abuse

ABILIFY MYCITE has not been systematically studied in humans for its potential for abuse, tolerance, or physical dependence. Consequently, patients should be evaluated carefully for a history of drug abuse, and such patients should be observed closely for signs of ABILIFY MYCITE misuse or abuse (e.g., development of tolerance, increases in dose, drug-seeking behavior).

9.3 Dependence

In physical dependence studies in monkeys, withdrawal symptoms were observed upon abrupt cessation of dosing. While the clinical trials did not reveal any tendency for any drug-seeking behavior, these observations were not systematic and it is not possible to predict on the basis of this limited experience the extent to which a CNS-active drug will be misused, diverted, and/or abused once marketed.

10 OVERDOSAGE

10.1 Human Experience

In clinical trials and in postmarketing experience, adverse reactions of deliberate or accidental overdosage with oral aripiprazole have been reported worldwide. These include overdoses with oral aripiprazole alone and in combination with other substances.

Common adverse reactions (reported in at least 5% of all overdose cases) reported with oral aripiprazole overdosage (alone or in combination with other substances) include vomiting, somnolence, and tremor. Other clinically important signs and symptoms observed in one or more patients with aripiprazole overdoses (alone or with other substances) include acidosis, aggression, aspartate aminotransferase increased, atrial fibrillation, bradycardia, coma, confusional state, convulsion, blood creatine phosphokinase increased, depressed level of consciousness, hypertension, hypokalemia, hypotension, lethargy, loss of consciousness, QRS complex prolonged, QT prolonged, pneumonia aspiration, respiratory arrest, status epilepticus, and tachycardia.

10.2 Management of Overdosage

No specific information is available on the treatment of overdose with ABILIFY MYCITE. If over-exposure occurs call your poison control center at 1-800-222-1222. An electrocardiogram should be obtained in case of overdosage and if QT interval prolongation is present, cardiac monitoring should be instituted. Otherwise, management of overdose should concentrate on supportive therapy, maintaining an adequate airway, oxygenation and ventilation, and management of symptoms. Close medical supervision and monitoring should continue until the patient recovers.

Charcoal: In the event of an overdose of ABILIFY MYCITE, an early charcoal administration may be useful in partially preventing the absorption of aripiprazole. Administration of 50 g of activated charcoal, one hour after a single 15 mg oral dose of aripiprazole, decreased the mean AUC and Cmax of aripiprazole by 50%.

Hemodialysis: Although there is no information on the effect of hemodialysis in treating an overdose with aripiprazole, hemodialysis is unlikely to be useful in overdose management since aripiprazole is highly bound to plasma proteins.

11 DESCRIPTION

ABILIFY MYCITE (aripiprazole tablets with sensor) is a drug-device combination product containing aripiprazole, an atypical antipsychotic, embedded with an Ingestible Event Marker (IEM) sensor.

Aripiprazole is 7-[4-[4-(2,3-dichlorophenyl)-1-piperazinyl]butoxy]-3,4-dihydrocarbostyril. The empirical formula is C23H27Cl2N3O2 and its molecular weight is 448.38. The chemical structure is:

ABILIFY MYCITE is available in 2 mg, 5 mg, 10 mg, 15 mg, 20 mg, and 30 mg strength tablets with sensor. Inactive ingredients of the tablets with sensor include cornstarch, hydroxypropyl cellulose, lactose monohydrate, magnesium stearate, and microcrystalline cellulose. Colorants include ferric oxide (yellow or red) and FD&C Blue No. 2 Aluminum Lake. Ingredients of the IEM include aluminum, cuprous chloride, ethyl cellulose, gold, hydroxypropyl cellulose, magnesium, silicon, silicon dioxide, silicon nitride, titanium-tungsten, titanium and triethyl citrate.

The ABILIFY MYCITE System is a drug-device combination product composed of the following components:

- An aripiprazole tablet with an embedded Ingestible Event Marker (IEM) sensor. The IEM is a 1 mm sized sensor embedded in the ABILIFY MYCITE tablets with sensor. Upon contact with gastric fluid, magnesium and cuprous chloride within the IEM react to activate and power the device. The IEM then communicates to the MYCITE Patch, to track aripiprazole ingestion.
- A MYCITE Patch (wearable sensor) is designed to detect the ingestion of the ABILIFY MYCITE tablets with sensor, record the ingestion of the IEM, and transmit ingestion data to the mobile patient application (app).
- A compatible app displays this data to allow patients to review their medication ingestion. These data can be shared with healthcare providers and caregivers.
- Web-based portal or dashboard for healthcare professionals and caregivers.

12 CLINICAL PHARMACOLOGY

12.1 Mechanism of Action

The mechanism of action of aripiprazole in the treatment of schizophrenia, bipolar I disorder, or adjunctive treatment of major depressive disorder is unknown. However, the efficacy of aripiprazole could be mediated through a combination of partial agonist activity at D2 and 5-HT1A receptors and antagonist activity at 5-HT2A receptors.

12.2 Pharmacodynamics

Aripiprazole exhibits high affinity for dopamine D2 and D3, serotonin 5-HT1A and 5-HT2A receptors (Ki values of 0.34 nM, 0.8 nM, 1.7 nM, and 3.4 nM, respectively), moderate affinity for dopamine D4, serotonin 5-HT2C and 5-HT7, alpha1-adrenergic and histamine H1 receptors (Ki values of 44 nM, 15 nM, 39 nM, 57 nM, and 61 nM, respectively), and moderate affinity for the serotonin reuptake site (Ki=98 nM). Aripiprazole has no appreciable affinity for cholinergic muscarinic receptors (IC50>1,000 nM). Actions at receptors other than D2, 5-HT1A, and 5-HT2A may explain some of the adverse reactions of aripiprazole (e.g., the orthostatic hypotension observed with aripiprazole may be explained by its antagonist activity at adrenergic alpha1 receptors).

12.3 Pharmacokinetics

Aripiprazole activity is presumably primarily due to the parent drug, aripiprazole, and to a lesser extent, to its major metabolite, dehydro-aripiprazole, which has been shown to have affinities for D2 receptors similar to the parent drug and represents 40% of the parent drug exposure in plasma. The mean elimination half-lives are about 75 hours and 94 hours for aripiprazole and dehydro-aripiprazole, respectively. Steady-state concentrations are attained within 14 days of dosing for both active moieties. Aripiprazole accumulation is predictable from single-dose pharmacokinetics. At steady-state, the pharmacokinetics of aripiprazole is dose-proportional. Elimination of aripiprazole is mainly through hepatic metabolism involving two P450 isozymes, CYP2D6 and CYP3A4. For CYP2D6 poor metabolizers, the mean elimination half-life for aripiprazole is about 146 hours.

Absorption

Aripiprazole is well absorbed after administration of the tablet, with peak plasma concentrations occurring within 3 hours to 5 hours; the absolute oral bioavailability of the tablet formulation is 87%. ABILIFY MYCITE can be administered with or without food. Administration of a 15 mg aripiprazole tablet with a standard high-fat meal did not significantly affect the Cmax or AUC of aripiprazole or its active metabolite, dehydro-aripiprazole, but delayed Tmax by 3 hours for aripiprazole and 12 hours for dehydro-aripiprazole.

Distribution

The steady-state volume of distribution of aripiprazole following intravenous administration is high (404 L or 4.9 L/kg), indicating extensive extravascular distribution. At therapeutic concentrations, aripiprazole and its major metabolite are greater than 99% bound to serum proteins, primarily to albumin. In healthy human volunteers administered 0.5 to 30 mg/day aripiprazole for 14 days, there was dose-dependent D2 receptor occupancy indicating brain penetration of aripiprazole in humans.

Elimination

Metabolism

Aripiprazole is metabolized primarily by three biotransformation pathways: dehydrogenation, hydroxylation, and N-dealkylation. Based on in vitro studies, CYP3A4 and CYP2D6 enzymes are responsible for dehydrogenation and hydroxylation of aripiprazole, and N-dealkylation is catalyzed by CYP3A4. Aripiprazole is the predominant drug moiety in the systemic circulation. At steady-state, dehydro-aripiprazole, the active metabolite, represents about 40% of aripiprazole AUC in plasma.

Excretion

Following a single oral dose of [^14C]-labeled aripiprazole, approximately 25% and 55% of the administered radioactivity was recovered in the urine and feces, respectively. Less than 1% of unchanged aripiprazole was excreted in the urine and approximately 18% of the oral dose was recovered unchanged in the feces.

Drug Interaction Studies

Effect of other drugs on the exposures of aripiprazole and dehydro-aripiprazole are summarized in Figure 1 and Figure 2, respectively. Based on simulation, a 4.5-fold increase in mean Cmax and AUC values at steady-state is expected when extensive metabolizers of CYP2D6 are administered with both strong CYP2D6 and CYP3A4 inhibitors. A 3-fold increase in mean Cmax and AUC values at steady-state is expected in poor metabolizers of CYP2D6 administered with strong CYP3A4 inhibitors.

Figure 1: The Effect of Other Drugs on Aripiprazole Pharmacokinetics

Figure 2: The Effect of Other Drugs on Dehydro-Aripiprazole Pharmacokinetics

The effect of aripiprazole on the exposures of other drugs are summarized in Figure 3. A population PK analysis in patients with major depressive disorder showed no substantial change in plasma concentrations of fluoxetine (20 or 40 mg/day), paroxetine CR (37.5 or 50 mg/day), or sertraline (100 or 150 mg/day) dosed to steady-state. The steady-state plasma concentrations of fluoxetine and norfluoxetine increased by about 18% and 36%, respectively, and concentrations of paroxetine decreased by about 27%. The steady-state plasma concentrations of sertraline and desmethylsertraline were not substantially changed when these antidepressant therapies were coadministered with aripiprazole.

Figure 3: The Effect of Aripiprazole on Pharmacokinetics of Other Drugs

Specific Populations

Exposure of aripiprazole and dehydro-aripiprazole in specific populations are summarized in Figure 4 and Figure 5, respectively.

Figure 4: Effect of Intrinsic Factors on Aripiprazole Pharmacokinetics

Figure 5: Effect of Intrinsic Factors on Dehydro-Aripiprazole Pharmacokinetics

13 NONCLINICAL TOXICOLOGY

13.1 Carcinogenesis, Mutagenesis, Impairment of Fertility

Carcinogenesis

Lifetime carcinogenicity studies were conducted in ICR mice, Sprague-Dawley (SD) rats, and F344 rats. Aripiprazole was administered for 2 years in the diet at doses of 1, 3, 10, and 30 mg/kg/day to ICR mice and 1, 3, and 10 mg/kg/day to F344 rats (0.2 to 5 times and 0.3 to 3 times the maximum recommended human dose [MRHD] based on mg/m^2, respectively). In addition, SD rats were dosed orally for 2 years at 10, 20, 40, and 60 mg/kg/day (3 to 19 times the MRHD based on mg/m^2). Aripiprazole did not induce tumors in male mice or male rats. In female mice, the incidences of pituitary gland adenomas and mammary gland adenocarcinomas and adenoacanthomas were increased at dietary doses of 3 to 30 mg/kg/day (0.1 to 0.9 times human exposure at MRHD based on AUC and 0.5 to 5 times the MRHD based on mg/m^2). In female rats, the incidence of mammary gland fibroadenomas was increased at a dietary dose of 10 mg/kg/day (0.1 times human exposure at MRHD based on AUC and 3 times the MRHD based on mg/m^2); and the incidences of adrenocortical carcinomas and combined adrenocortical adenomas/carcinomas were increased at an oral dose of 60 mg/kg/day (14 times human exposure at MRHD based on AUC and 19 times the MRHD based on mg/m^2).

Proliferative changes in the pituitary and mammary gland of rodents have been observed following chronic administration of other antipsychotic agents and are considered prolactin-mediated. Serum prolactin was not measured in the aripiprazole carcinogenicity studies. However, increases in serum prolactin levels were observed in female mice in a 13-week dietary study at the doses associated with mammary gland and pituitary tumors. Serum prolactin was not increased in female rats in 4-week and 13-week dietary studies at the dose associated with mammary gland tumors. The relevance for human risk of the findings of prolactin-mediated endocrine tumors in rodents is unknown.

Mutagenesis

The mutagenic potential of aripiprazole was tested in the in vitro bacterial reverse-mutation assay, the in vitro bacterial DNA repair assay, the in vitro forward gene mutation assay in mouse lymphoma cells, the in vitro chromosomal aberration assay in Chinese hamster lung (CHL) cells, the in vivo micronucleus assay in mice, and the unscheduled DNA synthesis assay in rats. Aripiprazole and a metabolite (2,3-DCPP) were clastogenic in the in vitro chromosomal aberration assay in CHL cells with and without metabolic activation. The metabolite, 2,3-DCPP, produced increases in numerical aberrations in the in vitro assay in CHL cells in the absence of metabolic activation. A positive response was obtained in the in vivo micronucleus assay in mice; however, the response was due to a mechanism not considered relevant to humans.

Impairment of Fertility

Female rats were treated with oral doses of 2, 6, and 20 mg/kg/day (0.6, 2, and 6 times the MRHD on a mg/m^2 basis) of aripiprazole from 2 weeks prior to mating through Day 7 of gestation. Estrus cycle irregularities and increased corpora lutea were seen at all doses, but no impairment of fertility was seen. Increased pre-implantation loss was seen at 6 and 20 mg/kg/day and decreased fetal weight was seen at 20 mg/kg/day.

Male rats were treated with oral doses of 20, 40, and 60 mg/kg/day (6, 13, and 19 times the MRHD on a mg/m^2 basis) of aripiprazole from 9 weeks prior to mating through mating. Disturbances in spermatogenesis were seen at 60 mg/kg and prostate atrophy was seen at 40 and 60 mg/kg, but no impairment of fertility was seen.

13.2 Animal Toxicology and/or Pharmacology

Aripiprazole produced retinal degeneration in albino rats in a 26-week chronic toxicity study at a dose of 60 mg/kg and in a 2-year carcinogenicity study at doses of 40 and 60 mg/kg. The 40 and 60 mg/kg/day doses are 13 and 19 times the maximum recommended human dose (MRHD) based on mg/m^2 and 7 to 14 times human exposure at MRHD based on AUC. Evaluation of the retinas of albino mice and of monkeys did not reveal evidence of retinal degeneration. Additional studies to further evaluate the mechanism have not been performed. The relevance of this finding to human risk is unknown.

14 CLINICAL STUDIES

14.1 Overview of the Clinical Studies

The safety and efficacy of aripiprazole tablets for the treatment of adults with schizophrenia, acute treatment of adults with manic and mixed episodes associated with Bipolar I disorder, and adjunctive treatment of adults with major depressive disorder (MDD) has been established and is based on the following adequate and well-controlled trials of aripiprazole tablets:

- Four short-term trials and one maintenance trial in adult patients with schizophrenia [see Clinical Studies (14.2)]
- Four short-term monotherapy trials and one 6-week adjunctive trial in adult patients with manic or mixed episodes [see Clinical Studies (14.3)]
- One maintenance monotherapy trial and in one maintenance adjunctive trial in adult patients with bipolar I disorder [see Clinical Studies (14.3)]
- Two short-term trials in adult patients with MDD who had an inadequate response to antidepressant therapy during the current episode [see Clinical Studies (14.4)]

14.2 Schizophrenia

The efficacy of aripiprazole tablets in the treatment of schizophrenia was evaluated in five short-term (4-week and 6-week), placebo-controlled trials of acutely relapsed inpatients who predominantly met DSM-III/IV criteria for schizophrenia. Four of the five trials were able to distinguish aripiprazole tablets from placebo, but one study, the smallest, did not. Three of these studies also included an active control group consisting of either risperidone (one trial) or haloperidol (two trials), but they were not designed to allow for a comparison of aripiprazole tablets and the active comparators.

In the four positive trials for aripiprazole tablets, four primary measures were used for assessing psychiatric signs and symptoms. Efficacy was evaluated using the total score on the Positive and Negative Syndrome Scale (PANSS). The PANSS is a 30-item scale that measures positive symptoms of schizophrenia (7 items), negative symptoms of schizophrenia (7 items), and general psychopathology (16 items), each rated on a scale of 1 (absent) to 7 (extreme); total PANSS scores range from 30 to 210. The Clinical Global Impression (CGI) assessment reflects the impression of a skilled observer, fully familiar with the manifestations of schizophrenia, about the overall clinical state of the patient.

In a 4-week trial (n=414) comparing two fixed doses of aripiprazole tablets (15 or 30 mg/day) to placebo, both doses of aripiprazole tablets were superior to placebo in the PANSS total score (Study 1 in Table 14), PANSS positive subscale, and CGI-severity score. In addition, the 15 mg dose was superior to placebo in the PANSS negative subscale.

In a 4-week trial (n=404) comparing two fixed doses of aripiprazole tablets (20 or 30 mg/day) to placebo, both doses of aripiprazole tablets were superior to placebo in the PANSS total score (Study 2 in Table 14), PANSS positive subscale, PANSS negative subscale, and CGI-severity score.

In a 6-week trial (n=420) comparing three fixed doses of aripiprazole tablets (10, 15, or 20 mg/day) to placebo, all three doses of aripiprazole tablets were superior to placebo in the PANSS total score (Study 3 in Table 14), PANSS positive subscale, and the PANSS negative subscale.

In a 6-week trial (n=367) comparing three fixed doses of aripiprazole tablets (2, 5, or 10 mg/day) to placebo, the 10 mg dose of aripiprazole tablets was superior to placebo in the PANSS total score (Study 4 in Table 14), the primary outcome measure of the study. The 2 and 5 mg doses did not demonstrate superiority to placebo on the primary outcome measure.

Thus, the efficacy of 10, 15, 20, and 30 mg daily doses was established in two studies for each dose. Among these doses, there was no evidence that the higher dose groups offered any advantage over the lowest dose group of these studies.

An examination of population subgroups did not reveal any clear evidence of differential responsiveness on the basis of age, gender, or race.

A longer-term trial enrolled 310 inpatients or outpatients meeting DSM-IV criteria for schizophrenia who were, by history, symptomatically stable on other antipsychotic medications for periods of 3 months or longer. These patients were discontinued from their antipsychotic medications and randomized to aripiprazole tablets 15 mg/day or placebo for up to 26 weeks of observation for relapse. Relapse during the double-blind phase was defined as CGI-Improvement score of ≥5 (minimally worse), scores ≥5 (moderately severe) on the hostility or uncooperativeness items of the PANSS, or ≥20% increase in the PANSS total score. Patients receiving aripiprazole tablets 15 mg/day experienced a significantly longer time to relapse over the subsequent 26 weeks compared to those receiving placebo (Study 5 in Figure 6).

Table 14: Schizophrenia Studies
Study Number | Treatment Group | Primary Efficacy Measure: PANSS
 |  | Mean Baseline Score (SD) | LS Mean Change from Baseline (SE) | Placebo-subtracted Difference [Difference (drug minus placebo) in least-squares mean change from baseline] (95% CI)
Study 1 | Aripiprazole tablets (15 mg/day) [Doses statistically significantly superior to placebo] | 98.5 (17.2) | -15.5 (2.40) | -12.6 (-18.9, -6.2)
 | Aripiprazole tablets (30 mg/day) | 99.0 (19.2) | -11.4 (2.39) | -8.5 (-14.8, -2.1)
 | Placebo | 100.2 (16.5) | -2.9 (2.36) | --
Study 2 | Aripiprazole tablets (20 mg/day) | 92.6 (19.5) | -14.5 (2.23) | -9.6 (-15.4, -3.8)
 | Aripiprazole tablets (30 mg/day) | 94.2 (18.5) | -13.9 (2.24) | -9.0 (-14.8, -3.1)
 | Placebo | 94.3 (18.5) | -5.0 (2.17) | --
Study 3 | Aripiprazole tablets (10 mg/day) | 92.7 (19.5) | -15.0 (2.38) | -12.7 (-19.00, -6.41)
 | Aripiprazole tablets (15 mg/day) | 93.2 (21.6) | -11.7 (2.38) | -9.4 (-15.71, -3.08)
 | Aripiprazole tablets (20 mg/day) | 92.5 (20.9) | -14.4 (2.45) | -12.1 (-18.53, -5.68)
 | Placebo | 92.3 (21.8) | -2.3 (2.35) | --
Study 4 | Aripiprazole tablets (2 mg/day) | 90.7 (14.5) | -8.2 (1.90) | -2.9 (-8.29, 2.47)
 | Aripiprazole tablets (5 mg/day) | 92.0 (12.6) | -10.6 (1.93) | -5.2 (-10.7, 0.19)
 | Aripiprazole tablets (10 mg/day) | 90.0 (11.9) | -11.3 (1.88) | -5.9 (-11.3, -0.58)
 | Placebo | 90.8 (13.3) | -5.3 (1.97) | --
SD: standard deviation; SE: standard error; LS Mean: least-squares mean; CI: unadjusted confidence interval.

Figure 6: Kaplan-Meier Estimation of Cumulative Proportion of Patients with Relapse (Schizophrenia Study 5)

14.3 Bipolar Disorder

Acute Treatment of Manic and Mixed Episodes

Monotherapy

The efficacy of aripiprazole tablets as monotherapy in the acute treatment of manic and mixed episodes associated with bipolar I disorder was established in four 3-week placebo-controlled trials in hospitalized patients who met the DSM-IV criteria for bipolar I disorder with manic or mixed episodes. These studies included patients with or without psychotic features and two of the studies also included patients with or without a rapid-cycling course.

The primary instrument used for assessing manic symptoms was the Young Mania Rating Scale (Y-MRS), an 11-item clinician-rated scale traditionally used to assess the degree of manic symptomatology in a range from 0 (no manic features) to 60 (maximum score). A key secondary instrument included the Clinical Global Impression-Bipolar (CGI-BP) Scale.

In the four positive, 3-week placebo-controlled trials (n=268; n=248; n=480; n=485) which evaluated aripiprazole tablets in a range of 15 mg to 30 mg, once daily (with a starting dose of 30 mg/day in two studies and 15 mg/day in two studies), aripiprazole tablets were superior to placebo in the reduction of Y-MRS total score (Studies 1 to 4 in Table 15) and CGI-BP Severity of Illness score (mania). In the two studies with a starting dose of 15 mg/day, 48% and 44% of patients were on 15 mg/day at endpoint. In the two studies with a starting dose of 30 mg/day, 86% and 85% of patients were on 30 mg/day at endpoint.

Adjunctive Therapy

The efficacy of adjunctive aripiprazole tablets with concomitant lithium or valproate in the treatment of manic or mixed episodes associated with Bipolar I Disorder was established in a 6-week placebo-controlled study (n=384) with a 2-week lead-in mood stabilizer monotherapy phase in adult patients who met DSM-IV criteria for bipolar I disorder. This study included patients with manic or mixed episodes and with or without psychotic features.

Patients were initiated on open-label lithium (0.6 to 1.0 mEq/L) or valproate (50 to 125 mcg/mL) at therapeutic serum levels and remained on stable doses for 2 weeks. At the end of 2 weeks, patients demonstrating inadequate response (Y-MRS total score ≥16 and ≤25% improvement on the Y-MRS total score) to lithium or valproate were randomized to receive either aripiprazole tablets (15 mg/day or an increase to 30 mg/day as early as Day 7) or placebo as adjunctive therapy with open-label lithium or valproate. In the 6-week placebo-controlled phase, adjunctive aripiprazole tablets starting at 15 mg/day with concomitant lithium or valproate (in a therapeutic range of 0.6 to 1.0 mEq/L or 50 to 125 mcg/mL, respectively) was superior to lithium or valproate with adjunctive placebo in the reduction of the Y-MRS total score (Study 5 in Table 15) and CGI-BP Severity of Illness score (mania). Seventy-one percent of the patients coadministered valproate and 62% of the patients coadministered lithium were on 15 mg/day at 6-week endpoint.

Table 15: Bipolar Studies
Study Number | Treatment Group | Primary Efficacy Measure: Y-MRS
 |  | Mean Baseline Score (SD) | LS Mean Change from Baseline (SE) | Placebo-subtracted Difference [Difference (drug minus placebo) in least-squares mean change from baseline.] (95% CI)
Study 1 | Aripiprazole tablets (30/15 mg/day) [Doses statistically significantly superior to placebo.] | 29.0 (5.9) | -12.52 (1.05) | -5.33 (-7.90, -2.76)
 | Placebo | 28.5 (4.6) | -7.19 (1.07) | --
Study 2 | Aripiprazole tablets (30/15 mg/day) | 27.8 (5.7) | -8.15 (1.23) | -4.80 (-7.80, -1.80)
 | Placebo | 29.1 (6.9) | -3.35 (1.22) | --
Study 3 | Aripiprazole tablets (15 to 30 mg/day) | 28.5 (5.6) | -12.64 (0.84) | -3.63 (-5.75, -1.51)
 | Placebo | 28.9 (5.9) | 9.01 (0.81) | --
Study 4 | Aripiprazole tablets (15 to 30 mg/day) | 28.0 (5.8) | -11.98 (0.80) | -2.28 (-4.44 , -0.11)
 | Placebo | 28.3 (5.8) | -9.70 (0.83) | --
Study 5 | Aripiprazole tablets (15 or 30 mg/day) + Lithium/Valproate | 23.2 (5.7) | -13.31 (0.50) | -2.62 (-4.29 , -0.95)
Study 5 | Placebo + Lithium/Valproate | 23.0 (4.9) | -10.70 (0.69) | --
SD: standard deviation; SE: standard error; LS Mean: least-squares mean; CI: unadjusted confidence interval.

Maintenance Treatment of Bipolar I Disorder

Monotherapy Maintenance Therapy

A maintenance trial was conducted in adult patients meeting DSM-IV criteria for bipolar I disorder with a recent manic or mixed episode who had been stabilized on open-label aripiprazole tablets and who had maintained a clinical response for at least 6 weeks. The first phase of this trial was an open-label stabilization period in which inpatients and outpatients were clinically stabilized and then maintained on open-label aripiprazole tablets (15 or 30 mg/day, with a starting dose of 30 mg/day) for at least 6 consecutive weeks. One hundred sixty-one outpatients were then randomized in a double-blind fashion to either the same dose of aripiprazole tablets they were on at the end of the stabilization and maintenance period or placebo and were then monitored for manic or depressive relapse. During the randomization phase, aripiprazole tablets were superior to placebo on time to the number of combined affective relapses (manic plus depressive), the primary outcome measure for this study (Study 7 in Figure 7). A total of 55 mood events were observed during the double-blind treatment phase. Nineteen were from the aripiprazole tablets group and 36 were from the placebo group. The number of observed manic episodes in the aripiprazole tablets group (6) were fewer than that in the placebo group (19), while the number of depressive episodes in the aripiprazole tablets group (9) was similar to that in the placebo group (11).

An examination of population subgroups did not reveal any clear evidence of differential responsiveness on the basis of age and gender; however, there were insufficient numbers of patients in each of the ethnic groups to adequately assess inter-group differences.

Figure 7: Kaplan-Meier Estimation of Cumulative Proportion of Patients with Relapse (Bipolar Study 7)

Adjunctive Maintenance Therapy

An adjunctive maintenance trial was conducted in adult patients meeting DSM-IV criteria for bipolar I disorder with a recent manic or mixed episode. Patients were initiated on open-label lithium (0.6 to 1.0 mEq/L) or valproate (50 to 125 mcg/mL) at therapeutic serum levels, and remained on stable doses for 2 weeks. At the end of 2 weeks, patients demonstrating inadequate response (Y-MRS total score ≥16 and ≤35% improvement on the Y-MRS total score) to lithium or valproate received aripiprazole tablets with a starting dose of 15 mg/day with the option to increase to 30 mg or reduce to 10 mg as early as Day 4, as adjunctive therapy with open-label lithium or valproate. Prior to randomization, patients on the combination of single-blind aripiprazole tablets and lithium or valproate were required to maintain stability (Y-MRS and MADRS total scores ≤12) for 12 consecutive weeks. Three hundred thirty-seven patients were then randomized in a double-blind fashion, to either the same dose of aripiprazole tablets they were on at the end of the stabilization period or placebo plus lithium or valproate and were then monitored for manic, mixed, or depressive relapse for a maximum of 52 weeks. Aripiprazole tablets were superior to placebo on the primary endpoint, time from randomization to relapse to any mood event (Study 8 in Figure 8). A mood event was defined as hospitalization for a manic, mixed, or depressive episode, study discontinuation due to lack of efficacy accompanied by Y-MRS score >16 and/or a MADRS >16, or an SAE of worsening disease accompanied by Y-MRS score >16 and/or a MADRS >16. A total of 68 mood events were observed during the double-blind treatment phase. Twenty-five were from the aripiprazole group and 43 were from the placebo group. The number of observed manic episodes in the aripiprazole group (7) were fewer than that in the placebo group (19), while the number of depressive episodes in the aripiprazole group (14) was similar to that in the placebo group (18). The Kaplan-Meier curves of the time from randomization to relapse to any mood event during the 52-week double-blind treatment phase for aripiprazole tablets and placebo groups are shown in Figure 8.

An examination of population subgroups did not reveal any clear evidence of differential responsiveness on the basis of age and gender; however, there were insufficient numbers of patients in each of the ethnic groups to adequately assess inter-group differences.

Figure 8: Kaplan-Meier Estimation of Cumulative Proportion of Patients with Relapse to Any Mood Event (Bipolar Study 8)

14.4 Adjunctive Treatment of Adults with Major Depressive Disorder

The efficacy of aripiprazole tablets in the adjunctive treatment of major depressive disorder (MDD) was demonstrated in two short-term (6-week), placebo-controlled trials of adult patients meeting DSM-IV criteria for MDD who had had an inadequate response to prior antidepressant therapy (1 to 3 courses) in the current episode and who had also demonstrated an inadequate response to 8 weeks of prospective antidepressant therapy (paroxetine extended-release, venlafaxine extended-release, fluoxetine, escitalopram, or sertraline). Inadequate response for prospective treatment was defined as less than 50% improvement on the 17-item version of the Hamilton Depression Rating Scale (HAMD17), minimal HAMD17 score of 14, and a Clinical Global Impressions Improvement rating of no better than minimal improvement. Inadequate response to prior treatment was defined as less than 50% improvement as perceived by the patient after a minimum of 6 weeks of antidepressant therapy at or above the minimal effective dose.

The primary instrument used for assessing depressive symptoms was the Montgomery-Asberg Depression Rating Scale (MADRS), a 10-item clinician-rated scale used to assess the degree of depressive symptomatology. The key secondary instrument was the Sheehan Disability Scale (SDS), a 3-item self-rated instrument used to assess the impact of depression on three domains of functioning with each item scored from 0 (not at all) to 10 (extreme).

In the two trials (n=381, n=362), aripiprazole tablets were superior to placebo in reducing mean MADRS total scores (Studies 1, 2 in Table 16). In one study, aripiprazole tablets were also superior to placebo in reducing the mean SDS score.

In both trials, patients received aripiprazole tablets adjunctive to antidepressants at a dose of 5 mg/day. Based on tolerability and efficacy, doses could be adjusted by 5 mg increments, one week apart. Allowable doses were: 2, 5, 10, 15 mg/day, and for patients who were not on potent CYP2D6 inhibitors fluoxetine and paroxetine, 20 mg/day. The mean final dose at the end point for the two trials was 10.7 and 11.4 mg/day.

An examination of population subgroups did not reveal evidence of differential response based on age, choice of prospective antidepressant, or race. With regards to gender, a smaller mean reduction on the MADRS total score was seen in males than in females.

Table 16: Adjunctive Treatment of Major Depressive Disorder Studies
Study Number | Treatment Group | Primary Efficacy Measure: MADRS
 |  | Mean Baseline Score (SD) | LS Mean Change from Baseline (SE) | Placebo-subtracted Difference [Difference (drug minus placebo) in least-squares mean change from baseline.] (95% CI)
Study 1 | Aripiprazole tablets (5 to 20 mg/day) [Doses statistically significantly superior to placebo.] + Antidepressant | 25.2 (6.2) | -8.49 (0.66) | -2.84 (-4.53, -1.15)
 | Placebo + Antidepressant | 27.0 (5.5) | -5.65 (0.64) | --
Study 2 | Aripiprazole tablets (5 to 20 mg/day) + Antidepressant | 26.0 (6.0) | -8.78 (0.63) | -3.01 (-4.66, -1.37)
 | Placebo + Antidepressant | 26.0 (6.5) | -5.77 (0.67) | --
SD: standard deviation; SE: standard error; LS Mean: least-squares mean; CI: unadjusted confidence interval.

16 HOW SUPPLIED/STORAGE AND HANDLING

16.1 How Supplied

The ABILIFY MYCITE kit contains aripiprazole tablets embedded with an Ingestible Event Marker (IEM) sensor co-packaged with MYCITE Patches (wearable sensors) (referred to as the patch). The patch is available as a:

- 2-component patch, comprised of a removable electronics module (referred to as the "pod") and an adhesive "strip" (see Table 18 and Figure 9). The pod contains electronic components to record drug ingestion information and transfer the data to a compatible smartphone. The 30 Day Starter kits contain (a) aripiprazole tablets with sensor, (b) strips, and (c) one pod; whereas, the Maintenance kits contain (a) aripiprazole tablets with sensor and (b) strips [see Dosage and Administration (2.2)].

The patch has a corresponding IFU within the app. The status of the patch is indicated by a status icon in the app to inform the user that the patch is properly adhered and fully functioning.

Figure 9: MYCITE Patch (2-component)

Assembled

ABILIFY MYCITE Kits (2-component patch)

ABILIFY MYCITE kits are available in the following strengths and packages:

Strength | Color/ Shape | Markings | Pack Size and Components (2-component patch) [The Maintenance Kits do not include the pod.] | NDC Code
2 mg | pale green modified rectangle | "DA-029" and "2" | 30 Day Starter kit: Bottle of 30 tablets with sensor + 1 MYCITE pod and 7 MYCITE strips | 59148-029-61
2 mg | pale green modified rectangle | "DA-029" and "2" | Maintenance kit: Bottle of 30 tablets with sensor + 7 MYCITE strips | 59148-029-72
5 mg | pale blue modified rectangle | "DA-030 and "5" | 30 Day Starter kit: Bottle of 30 tablets with sensor + 1 MYCITE pod and 7 MYCITE strips | 59148-030-61
5 mg | pale blue modified rectangle | "DA-030 and "5" | Maintenance kit: Bottle of 30 tablets with sensor + 7 MYCITE strips | 59148-030-72
10 mg | off-white to pale pink modified rectangle | "DA-031" and "10" | 30 Day Starter kit: Bottle of 30 tablets with sensor + 1 MYCITE pod and 7 MYCITE strips | 59148-031-61
10 mg | off-white to pale pink modified rectangle | "DA-031" and "10" | Maintenance kit: Bottle of 30 tablets with sensor + 7 MYCITE strips | 59148-031-72
15 mg | pale yellow round | "DA-032" and "15" | 30 Day Starter kit: Bottle of 30 tablets with sensor + 1 MYCITE pod and 7 MYCITE strips | 59148-032-61
15 mg | pale yellow round | "DA-032" and "15" | Maintenance kit: Bottle of 30 tablets with sensor + 7 MYCITE strips | 59148-032-72
20 mg | white to pale yellowish white round | "DA-033" and "20" | 30 Day Starter kit: Bottle of 30 tablets with sensor + 1 MYCITE pod and 7 MYCITE strips | 59148-033-61
20 mg | white to pale yellowish white round | "DA-033" and "20" | Maintenance kit: Bottle of 30 tablets with sensor + 7 MYCITE strips | 59148-033-72
30 mg | off-white to pale pink round | "DA-034" and "30" | 30 Day Starter kit: Bottle of 30 tablets with sensor + 1 MYCITE pod and 7 MYCITE strips | 59148-034-61
30 mg | off-white to pale pink round | "DA-034" and "30" | Maintenance kit: Bottle of 30 tablets with sensor + 7 MYCITE strips | 59148-034-72

16.2 Storage

Tablet bottle:

Store 20°C to 25°C (68°F to 77°F); excursions permitted between 15°C to 30°C (59°F to 86°F) [see USP Controlled Room Temperature].

Do not store in conditions where tablets are exposed to humid conditions.

MYCITE Patch (Wearable Sensor):

Store between 5°C and 27°C (41°F to 81°F), 15% to 93% relative humidity.

17 PATIENT COUNSELING INFORMATION

Advise the patient to read the FDA-approved patient labeling (Medication Guide).

General Instructions for Use

Instruct patients to:

- Refer to the app store to ensure compatibility with their specific smartphone.
- First download the MYCITE App and follow instructions provided by the app.

Advise patients that:

- The initial use should be facilitated by the healthcare provider [see Dosage and Administration (2.1)].
- They need a functioning pod before using the Maintenance Kit [see How Supplied/Storage and Handling (16.1)].

Advise patients that most ingestions will be detected within 30 minutes; however, in some cases it can take over two hours for the smartphone app and web portal to detect the ingestion of ABILIFY MYCITE. In some cases, the ingestion of the tablet may not be detected. If the tablet is not detected after ingestion, the dose should not be repeated.

Managing Lost or Disabled Smartphone

Advise patients that if their smartphone is lost, impaired or otherwise rendered unusable, some information collected by the system (synced) may be lost. Advise patients to change their MYCITE Patch immediately and connect to a new smartphone using their current account information. Information previously synced to the patients account will be available.

Using the MYCITE Patch in Different Environments

The MYCITE Patch will communicate with a paired device when it is within 9-foot proximity. The MYCITE Patch should remain on an individual whether they are showering, swimming, or exercising as it is intended to tolerate water or perspiration. Patients undergoing an MRI, however, need to remove their patch and replace with a new one as soon as possible. In order for the MYCITE Patch to communicate with a smartphone, the device must be powered on and Bluetooth®-enabled.

Suicidal Thoughts and Behaviors

Advise patients and caregivers to look for the emergence of suicidality, especially early during treatment and when the dosage is adjusted up or down and instruct them to report such symptoms to the healthcare provider [see Boxed Warning, Warnings and Precautions (5.2)].

Neuroleptic Malignant Syndrome (NMS)

Counsel patients about a potentially fatal adverse reaction referred to as Neuroleptic Malignant Syndrome (NMS) that has been reported in association with administration of antipsychotic drugs. Advise patients to contact a healthcare provider or report to the emergency room if they experience signs or symptoms of NMS [see Warnings and Precautions (5.4)].

Tardive Dyskinesia

Advise patients that abnormal involuntary movements have been associated with the administration of antipsychotic drugs. Counsel patients on the signs and symptoms of tardive dyskinesia and to contact their healthcare provider if these abnormal movements occur [see Warnings and Precautions (5.5)].

Metabolic Changes

Educate patients about the risk of metabolic changes, how to recognize symptoms of hyperglycemia and diabetes mellitus, and the need for specific monitoring, including blood glucose, lipids, and weight [see Warnings and Precautions (5.6)].

Pathological Gambling and Other Compulsive Behaviors

Advise patients and their caregivers of the possibility that they may experience compulsive urges to shop, increased urges to gamble, compulsive sexual urges, binge eating and/or other compulsive urges and the inability to control these urges while taking aripiprazole. In some cases, but not all, the urges were reported to have stopped when the dose was reduced or stopped [see Warnings and Precautions (5.7)].

Orthostatic Hypotension and Syncope

Educate patients about the risk of orthostatic hypotension and syncope especially early in treatment, when re-initiating treatment, or when increasing the dosage [see Warnings and Precautions (5.8)].

Leukopenia, Neutropenia and Agranulocytosis

Advise patients with a pre-existing low WBC or a history of drug induced leukopenia/neutropenia that they should have their CBC monitored while taking ABILIFY MYCITE [see Warnings and Precautions (5.10)].

Interference with Cognitive and Motor Performance

Because ABILIFY MYCITE may have the potential to impair judgment, thinking, or motor skills, patients should be cautioned about operating hazardous machinery, including automobiles, until they are reasonably certain that ABILIFY MYCITE therapy does not affect them adversely [see Warnings and Precautions (5.12)].

Heat Exposure and Dehydration

Counsel patients regarding appropriate care in avoiding overheating and dehydration [see Warnings and Precautions (5.13)].

Concomitant Medication

Patients should be advised to inform their physicians if they are taking, or plan to take, any prescription or over-the-counter drugs, since there is a potential for interactions [see Drug Interactions (7)].

Pregnancy

Advise patients to notify their healthcare provider if they become pregnant or intend to become pregnant during treatment with ABILIFY MYCITE. Advise patients that ABILIFY MYCITE may cause extrapyramidal and/or withdrawal symptoms (agitation, hypertonia, hypotonia, tremor, somnolence, respiratory distress, and feeding disorder). Advise patients that there is a pregnancy exposure registry that monitors pregnancy outcomes in women exposed to ABILIFY MYCITE during pregnancy [see Use In Specific Populations (8.1)].

Lactation

ABILIFY MYCITE use during pregnancy may affect milk supply. Advise the lactating patient to discuss any plans for breastfeeding with their healthcare provider, and to monitor the breastfed infant for dehydration and lack of appropriate weight gain [see Use in Specific Populations (8.2)].

Tablets with embedded IEM sensors Manufactured by Otsuka Pharmaceutical Co., Ltd., Tokyo, 101-8535 Japan

MYCITE Patches Manufactured for Otsuka America Pharmaceutical, Inc. 3956 Point Eden Way, Hayward, CA 94545 USA

Distributed and marketed by Otsuka America Pharmaceutical, Inc., Rockville, MD 20850 USA

ABILIFY MYCITE® and MYCITE® are registered trademarks of Otsuka Pharmaceutical Co., Ltd.

©2025, Otsuka Pharmaceutical Co., Ltd., Tokyo, 101-8535 Japan

MEDICATION GUIDE
ABILIFY MYCITE® (a BIL ĭ fī - Mi SIHYT)
(aripiprazole tablets with sensor), for oral use

Important:

- If you are taking ABILIFY MYCITE with other medicines for treatment of major depressive disorder (MDD), you should also read the Medication Guides or Patient Information that comes with the other medicines.
- The ABILIFY MYCITE System has 4 parts:
  - Aripiprazole tablet with an Ingestible Event Marker (IEM) sensor inside it (ABILIFY MYCITE).
  - MYCITE Patch (wearable sensor) that picks up (detects) the signal from the IEM sensor after you take the ABILIFY MYCITE tablet and sends the information to a smartphone.
  - MYCITE App, which is a smartphone application (app) that is used with a compatible smartphone to show information about when you take your ABILIFY MYCITE tablet.
  - Web-based portal for healthcare providers and caregivers.
- Download the MYCITE App before using the ABILIFY MYCITE System. Always follow the instructions provided within the MYCITE App when using the ABILIFY MYCITE System.
- Your healthcare provider should show you how to use the ABILIFY MYCITE System before you use it for the first time.

What is the most important information I should know about ABILIFY MYCITE?
ABILIFY MYCITE may cause serious side effects, including:

- Increased risk of death in elderly people with dementia-related psychosis. Medicines like ABILIFY MYCITE can raise the risk of death in elderly people who have lost touch with reality (psychosis) due to confusion and memory loss (dementia). ABILIFY MYCITE is not approved for the treatment of people who have lost touch with reality (psychosis) due to confusion or memory loss (dementia).
- Increased risk of suicidal thoughts or actions in children and young adults. Antidepressant medicines may increase suicidal thoughts or actions in some children and young adults within the first few months of treatment and when the dose is changed. It is not known if ABILIFY MYCITE is safe and effective for use in children.
  - How can I watch for and try to prevent suicidal thoughts and actions in myself or a family member?
    - Pay close attention to any changes, especially sudden changes, in mood, behaviors, thoughts, or feelings. This is very important when an antidepressant medicine is started or when the dose is changed.
    - Call the healthcare provider right away to report new or sudden changes in mood, behavior, thoughts, or feelings.
    - Keep all follow-up visits with the healthcare provider as scheduled. Call the healthcare provider between visits as needed, especially if you have concerns about symptoms.

What is ABILIFY MYCITE?
ABILIFY MYCITE is a prescription medicine of aripiprazole tablets with an Ingestible Event Marker (IEM) sensor inside it used:

- To treat adults with schizophrenia
- To treat bipolar I disorder:
  - short-term (acute) treatment of adults with manic or mixed episodes alone or when used with the medicine lithium or valproate
  - maintenance treatment of adults alone or when used with the medicine lithium or valproate
- To treat adults with major depressive disorder (MDD) along with other antidepressant medicines

The ABILIFY MYCITE System is meant to track if you have taken your ABILIFY MYCITE.
It is not known if ABILIFY MYCITE can improve how well you take your aripiprazole (patient compliance) or for changing your dose of aripiprazole.
There may be a delay in the detection of the ABILIFY MYCITE tablet and sometimes the detection of the tablet might not happen at all. ABILIFY MYCITE is not for use as real-time or emergency monitoring.
It is not known if ABILIFY MYCITE is safe or effective for use in children.

Do not take ABILIFY MYCITE if you are allergic to aripiprazole or any of the ingredients in ABILIFY MYCITE. See the end of this Medication Guide for a complete list of ingredients in ABILIFY MYCITE.

Before taking ABILIFY MYCITE, tell your healthcare provider about all your medical conditions, including if you:

- have diabetes or high blood sugar or have a family history of diabetes or high blood sugar. Your healthcare provider should check your blood sugar before you start and during treatment with ABILIFY MYCITE.
- have or had seizures (convulsions)
- have or had low or high blood pressure
- have or had heart problems or stroke
- have or had a low white blood cell count
- are pregnant or plan to become pregnant. Talk to your healthcare provider about the risk to your unborn baby if you take ABLIFY MYCITE during pregnancy.
  - Tell your healthcare provider if you become pregnant or think you are pregnant during treatment with ABILIFY MYCITE.
  - If you become pregnant during treatment with ABILIFY MYCITE, talk to your healthcare provider about registering with the National Pregnancy Registry for Atypical Antipsychotics. You can register by calling 1-866-961-2388 or go to http://womensmentalhealth.org/clinical-and-research-programs/pregnancyregistry/.
- are breastfeeding or plan to breastfeed. ABILIFY MYCITE can pass into your breast milk. Talk to your healthcare provider about the best way to feed your baby during treatment with ABILIFY MYCITE.

Tell your healthcare provider about all the medicines that you take, including prescription and over-the-counter medicines, vitamins, and herbal supplements.
ABILIFY MYCITE and other medicines may affect each other causing possible serious side effects. ABILIFY MYCITE may affect the way other medicines work, and other medicines may affect how ABILIFY MYCITE works.
Your healthcare provider can tell you if it is safe to take ABILIFY MYCITE with your other medicines. Do not start or stop any other medicines during treatment with ABILIFY MYCITE without talking to your healthcare provider first.
Know the medicines you take. Keep a list of your medicines to show your healthcare provider and pharmacist when you get a new medicine.

How should I take ABILIFY MYCITE?

- See the MYCITE App for instructions about how to apply and wear the MYCITE Patch and how to use the ABILIFY MYCITE System the right way.
- Take ABILIFY MYCITE exactly as your healthcare provider tells you to take it. Do not change the dose or stop taking ABILIFY MYCITE without first talking to your healthcare provider.
- Take ABILIFY MYCITE by mouth with or without food.
- Swallow ABILIFY MYCITE tablets whole. Do not divide, crush, or chew ABILIFY MYCITE tablets.
- The ABILIFY MYCITE tablet is usually detected within 30 minutes after you take it, but there may be a delay of more than 2 hours for the smartphone app and web portal to detect that you have taken ABILIFY MYCITE, and sometimes the ABILIFY MYCITE tablet might not be detected at all. If the tablet is not detected after you take it, do not repeat the dose.
- If over-exposure occurs, call your poison control center at 1-800-222-1222.

What should I avoid while taking ABILIFY MYCITE?

- Do not drive, operate heavy machinery, or do other dangerous activities until you know how ABILIFY MYCITE affects you. ABILIFY MYCITE may make you drowsy.
- Do not become too hot or dehydrated during treatment with ABILIFY MYCITE.
  - Do not exercise too much.
  - In hot weather, stay inside in a cool place if possible.
  - Stay out of the sun.
  - Do not wear too much clothing or heavy clothing.
  - Drink plenty of water.

What are the possible side effects of ABILIFY MYCITE?
ABILIFY MYCITE may cause serious side effects, including:

- See "What is the most important information I should know about ABILIFY MYCITE?"
- Stroke (cerebrovascular problems) in elderly people with dementia-related psychosis that can lead to death.
- Neuroleptic malignant syndrome (NMS), a serious condition that can lead to death. Call your healthcare provider or go to the nearest hospital emergency room right away if you have some or all of the following signs and symptoms of NMS:
  - high fever
  - stiff muscles
  - confusion
  - sweating
  - changes in pulse, heart rate, and blood pressure
- Uncontrolled body movements (tardive dyskinesia). ABILIFY MYCITE may cause movements that you cannot control in your face, tongue, or other body parts. Tardive dyskinesia may not go away, even if you stop taking ABILIFY MYCITE. Tardive dyskinesia may also start after you stop taking ABILIFY MYCITE.
- Problems with your metabolism such as:
  - high blood sugar (hyperglycemia) and diabetes. Increases in blood sugar can happen in some people who take ABILIFY MYCITE. Extremely high blood sugar can lead to coma or death. If you have diabetes or risk factors for diabetes (such as being overweight or a family history of diabetes), your healthcare provider should check your blood sugar before you start and during your treatment with ABILIFY MYCITE.
    Call your healthcare provider if you have any of these symptoms of high blood sugar during treatment with ABILIFY MYCITE:
    - feel very thirsty
    - need to urinate more than usual
    - feel very hungry
    - feel weak or tired
    - feel sick to your stomach
    - feel confused, or your breath smells fruity
  - increased fat levels (cholesterol and triglycerides) in your blood.
  - weight gain. You and your healthcare provider should check your weight regularly.
- Unusual urges. Some people taking ABILIFY MYCITE have had unusual urges, such as gambling, binge eating or eating that you cannot control (compulsive), compulsive shopping and sexual urges. If you or your family members notice that you are having unusual urges or behaviors, talk to your healthcare provider.
- Decreased blood pressure (orthostatic hypotension). You may feel lightheaded or faint when you rise too quickly from a sitting or lying position.
- Falls
- Low white blood cell count. Your healthcare provider may do blood tests during the first few months of treatment with ABILIFY MYCITE.
- Seizures (convulsions)
- Problems controlling your body temperature so that you feel too warm. See "What should I avoid while taking ABILIFY MYCITE?"
- Difficulty swallowing

The most common side effects of ABILIFY MYCITE in adults include:

- restlessness or need to move (akathisia)
- dizziness
- nausea
- insomnia
- shaking (tremor)
- anxiety
- constipation
- sedation

These are not all the possible side effects of ABILIFY MYCITE.
Call your doctor for medical advice about side effects. You may report side effects to FDA at 1-800-FDA-1088.

How should I store ABILIFY MYCITE?

- Store ABILIFY MYCITE tablets at room temperature, between 68°F to 77°F (20°C to 25°C).
- Store MYCITE Patches between 41°F to 81°F (5°C to 27°C).
- Keep ABILIFY MYCITE tablets and MYCITE Patches (wearable sensor) dry. Do not store ABILIFY MYCITE tablets and Patches (wearable sensor) in places with high humidity.

Keep ABILIFY MYCITE and all medicines out of the reach of children.

General information about the safe and effective use of ABILIFY MYCITE.
Medicines are sometimes prescribed for purposes other than those listed in a Medication Guide. Do not use ABILIFY MYCITE for a condition for which it was not prescribed. Do not give ABILIFY MYCITE to other people, even if they have the same symptoms you have. It may harm them. You can ask your healthcare provider or pharmacist for information about ABILIFY MYCITE that was written for healthcare professionals.

What are the ingredients in ABILIFY MYCITE?
Active ingredient: aripiprazole
Inactive ingredients: cornstarch, hydroxypropyl cellulose, lactose monohydrate, magnesium stearate, and microcrystalline cellulose, and Ingestible Event Marker (IEM). Colorants include ferric oxide (yellow or red) and FD&C Blue No. 2 Aluminum Lake. Ingredients of the IEM include aluminum, cuprous chloride, ethyl cellulose, gold, hydroxypropyl cellulose, magnesium, silicon, silicon dioxide, silicon nitride, titanium-tungsten, titanium and triethyl citrate.
Manufactured by:
Tablets with embedded IEM sensors Manufactured by Otsuka Pharmaceutical Co., Ltd., Tokyo, 101-8535 Japan
MYCITE Patches Manufactured for Otsuka America Pharmaceutical, Inc. 3956 Point Eden Way, Hayward, CA 94545 USA
Distributed and marketed by Otsuka America Pharmaceutical, Inc., Rockville, MD 20850 USA
ABILIFY MYCITE® and MYCITE® are registered trademarks of Otsuka Pharmaceutical Company.
©2025, Otsuka Pharmaceutical Co., Ltd., Tokyo, 101-8535 Japan
For more information about ABILIFY MYCITE go to www.abilifymycite.com or call 1-844-692-4834.

This Medication Guide has been approved by the U.S. Food and Drug Administration.

Revised: 12/2020

INSTRUCTIONS FOR USE

01_GETTING_STARTED

ANIMATION: MyCite logo fades in, followed by section title. | ANIMATION: Three containers expand with a generic phone w/ MyCite app, a patch, and a MyCite tablet. Patch and pod are separated slightly in space. | ANIMATION: Containers fade out, the three items rearrange from a column to a circle. Patch and pod come together before moving. | ANIMATION: A line draws from the bottle to the patch, leaving a dotted line behind.
VO: | VO: The MyCite system works in three connected parts: the MyCite App, a two-part patch consisting of a pod and adhesive strip, and an Abilify MyCite tablet with an ingestible sensor. | VO: | VO: The Abilify MyCite Tablet sends a signal to the Patch when you swallow your medication. The Patch records when you've taken your medication, as well as your sleep and activity levels.

ANIMATION: The line segments draw in until a circle is formed. The circle rotates. | ANIMATION: The phone expands to fill the screen, the rest of the scene fades. | ANIMATION: The shot stays on the phone. An indicator pops over the "Create an Account" button to indicate a click. | ANIMATION: Shot fades to disclaimer screen.
VO: Then your patch communicates this information to the App. The App lets you view your information and share it with your healthcare provider. | VO: (cont.) | VO: This app will help you set up and use your MyCite system. First, create your account, and then follow along to complete the set-up process. | VO:

02_PREPARING_YOUR_SKIN

ANIMATION: MyCite logo fades in, followed by section title | ANIMATION: Four lines of copy fade in. A rectangle expands from the left to highlight the current chapter title | ANIMATION: Four lines of copy fade in. A rectangle expands from the left to highlight the current chapter title | ANIMATION: Shot of figure fades in, slowly zooms in on the patch location. Box expands out from the bottom.
VO: There are four steps to prepare your patch. A series of videos will walk you through each step. Please follow these steps to ensure your MyCite system is set up correctly, starting with preparing your skin. | VO: (cont.) | VO: (cont.) | VO: Find a spot on your stomach, as shown here.

ANIMATION: Figure fully lifts up shirt to reveal the area of interest, and dotted line draws in on area of interest. Box fully expands on the bottom of the screen, and populates with relevant text from the VO. | ANIMATION: Figure demonstrates the cleaning process.
VO: Do not place the MyCite patch in areas where the skin is scraped, cracked, inflamed, or irritated, or in a location that overlaps the area of the most recently removed patch. If there is skin irritation, you should remove the patch. | VO: Gently clean the area with soap and water. Some men may need to trim hair in this area.

03_OPENING_YOUR_POD_&_STRIP

ANIMATION: MyCite logo fades in, followed by section title | ANIMATION: Four lines of copy fade in. A rectangle expands from the left to highlight the current chapter title | ANIMATION: Four lines of copy fade in. A rectangle expands from the left to highlight the current chapter title | ANIMATION: MyCite packaging moves in from left
VO: | VO: Now we'll help you open your pod and adhesive strip. Together they will create your patch. | VO: (cont.) | VO: Inside the Abilify MyCite kit, you'll find Part 2, the pod and the strips.

ANIMATION: main packaging exits left, pod + patch packaging enters from right | ANIMATION: pod + patch packaging exits left, pod + patch models move in from right and spin in space. | ANIMATION: Hand places pod on table | ANIMATION: Hand places strip on table.
VO: (cont.) | VO: Take out your pod and strip. DO NOT dispose of this Pod. You will use this Pod throughout your treatment on MyCite. Your app will prompt you each week to change your strip." | VO: Place the pod and strip on a flat surface near your phone. | VO: (cont.)

04_PAIRING YOUR PATCH

ANIMATION: MyCite logo fades in, followed by section title | ANIMATION: Four lines of copy fade in. A rectangle expands from the left to highlight the current chapter title | ANIMATION: Four lines of copy fade in. A rectangle expands from the left to highlight the current chapter title | ANIMATION: Fade to shot of table with generic phone, the strip and the pod.
VO: | VO: | VO: | VO: Your Pod and Strip should be on a flat surface near your phone. We'll show you how to connect your patch.

ANIMATION: A hand picks up the pod and another hand holds the strip steady. | ANIMATION: The pod is inserted into the strip | ANIMATION: Once the pod is slotted, the light blinks green. | ANIMATION: The hands exit and the shot stays on the slotted strip with the light blinking green.
VO: Insert the pod into the strip until you hear a click, then wait for the blinking green light. | VO: (cont.) | VO: This signals that the pod is inserted correctly creating your patch, and is now connected to your phone. | VO:

05_APPLYING_YOUR_PATCH

ANIMATION: MyCite logo fades in, followed by section title | ANIMATION: Four lines of copy fade in. A rectangle expands from the left to highlight the current chapter title | ANIMATION: Four lines of copy fade in. A rectangle expands from the left to highlight the current chapter title | ANIMATION: The shot fades to the shot of the prepared location on the torso from video 2
VO: | VO: And now we'll help you apply your Patch | VO: (cont.) | VO: You must place the Patch on your stomach, as shown here.

ANIMATION: Dotted line appears around the target location. | ANIMATION: Shot fades to a view of the back of the patch, and a hand peels off both parts of the paper backing. | ANIMATION: Hand places the patch on the designated spot on the torso. | ANIMATION: The fingers smooth out the edges of the strip.
VO: Unlike other Patches you may have seen, the MyCite Patch will only work if it's placed on your stomach . Remember, the Patch does not contain any medication. | VO: If you haven't already, peel off the large piece of paper backing. Then peel off the small piece. Try not to wrinkle the Patch. | VO: Standing in a comfortable, upright position, apply the Patch over the area you've prepared on your stomach. | VO: Then, smooth out any bubbles with your fingers, like this. Keep the patch on when showering, swimming, or exercising. Put the patch in a new location each time you apply a new strip.

06_TAKING_YOUR_TABLET

ANIMATION: MyCite logo fades in, followed by section title | ANIMATION: A 3D model of the MyCite bottle fades in and rotates slowly in place. | ANIMATION: MyCite bottle exits to the left, and the tablet icon enteres from the right. | ANIMATION: Label for tablet draws in.
VO: | VO: Inside the Abilify MyCite kit, you'll find the container labeled "Part 3 Tablets," only the Abilify MyCite tablets will work with MyCite. | VO: | VO: Take your Abilify MyCite tablet now, unless you have already taken it today.

ANIMATION: Tablet moves to the left and glass moves in from the right. Plus sign draws in. | ANIMATION: The tablet is crossed out | ANIMATION: The crossed-out tablet cracks | ANIMATION: Shot of tablet fades to white, a generic phone with the verification screen moves in from the bottom.
VO: Be sure to take it with plenty of water. | VO: Swallow your tablet whole; do not divide, crush, or chew. Remember to take your medication as prescribed by your healthcare provider. | VO: (cont.) | VO: Once you've taken your tablet, your App will let you know when your Tablet has registered.

ANIMATION: Generic phone is centered on screen. Show tap on Continue. | ANIMATION: Modal disapears to reveal home screen. | ANIMATION: Zooms in on the home screen. | ANIMATION: Tiles slide down to display all is good.
VO: Do not change your medication pattern or dosage based on what the MyCite shows you. If you want to change your medication regimen, consult your healthcare provider. | VO: This is your home screen on the MyCite app. |  | VO: Your Tablet Status appears at the top when your Abilify MyCite tablet has registered.

ANIMATION: Highlight patch status button and the patch status turns red and back to green | ANIMATION: Highlight hamburger. | ANIMATION: Highlight disapears. Immediately show a tap on the menu icon. | ANIMATION: Home menu expands from the left while background overlay appears over homescren. Show Tap on Weekly view.
VO: A red Check Patch button means your patch is not working Properly. Tap the button to review your patch status and to resolve any issues, such as changing your patch every seven days. A green Patch OK button means your patch is working properly. | VO:In the upper left hand corner, you'll find the menu icon. | VO: Tap the menu icon to go to your home Menu. | VO: From the home menu select Weekly View.

ANIMATION: After tap on "Weekly View", the perspective rotates and the weekly view screen fades in. | ANIMATION: Green checkmark is highlighted, then red X, then an ! in the same fashion. | ANIMATION: the perspective rotates to Home menu over the background overlay of homescren. Show Tap on Monthly view. | ANIMATION: After tap on Monthly View", the perspective rotates and the monthly view screen fades in.
VO: Here, you can view your information for current and past weeks. | VO: A green Check indicates that your tablet has been registered. An X indicates when a tablet has not registered. An exclamation point shows when more than one tablet has registered. | VO: You can also view your historical information for current or past months.

PRINCIPAL DISPLAY PANEL - Starter Kit Carton - 2 mg

30 tablets
Rx only
NDC 59148-029-61

New 2-Component
Patch Design

Abilify MyCite®
(aripiprazole tablets with sensor)
30-Day Starter Kit

Dispense the accompanying Medication Guide to each patient.

Needs a compatible mobile device.
Keep Abilify MyCite® components out of the reach of children. Swallow tablets whole. Do not divide, crush or chew.

2 mg

PRINCIPAL DISPLAY PANEL - Maintenance Kit Carton - 2 mg

30 tablets
Rx only
NDC 59148-029-72

For
New 2-Component
Patch Design

Abilify MyCite®
(aripiprazole tablets with sensor)

Maintenance Kit (tablets with sensor & strips)

Dispense the accompanying Medication Guide to each patient.

Needs a compatible mobile device.
Keep Abilify MyCite® components out of the reach of children. Swallow tablets whole. Do not divide, crush or chew.

2 mg

PRINCIPAL DISPLAY PANEL - Starter Kit Carton - 5 mg

30 tablets
Rx only
NDC 59148-030-61

New 2-Component
Patch Design

Abilify MyCite®
(aripiprazole tablets with sensor)
30-Day Starter Kit

Dispense the accompanying Medication Guide to each patient.

Needs a compatible mobile device.
Keep Abilify MyCite® components out of the reach of children. Swallow tablets whole. Do not divide, crush or chew.

5 mg

PRINCIPAL DISPLAY PANEL - Maintenance Kit Carton - 5 mg

30 tablets
Rx only
NDC 59148-030-72

For
New 2-Component
Patch Design

Abilify MyCite®
(aripiprazole tablets with sensor)

Maintenance Kit (tablets with sensor & strips)

Dispense the accompanying Medication Guide to each patient.

Needs a compatible mobile device.
Keep Abilify MyCite® components out of the reach of children. Swallow tablets whole. Do not divide, crush or chew.

5 mg

PRINCIPAL DISPLAY PANEL - Starter Kit Carton - 10 mg

30 tablets
Rx only
NDC 59148-031-61

New 2-Component
Patch Design

Abilify MyCite®
(aripiprazole tablets with sensor)
30-Day Starter Kit

Dispense the accompanying Medication Guide to each patient.

Needs a compatible mobile device.
Keep Abilify MyCite® components out of the reach of children. Swallow tablets whole. Do not divide, crush or chew.

10 mg

PRINCIPAL DISPLAY PANEL - Maintenance Kit Carton - 10 mg

30 tablets
Rx only
NDC 59148-031-72

For
New 2-Component
Patch Design

Abilify MyCite®
(aripiprazole tablets with sensor)

Maintenance Kit (tablets with sensor & strips)

Dispense the accompanying Medication Guide to each patient.

Needs a compatible mobile device.
Keep Abilify MyCite® components out of the reach of children. Swallow tablets whole. Do not divide, crush or chew.

10 mg

PRINCIPAL DISPLAY PANEL - Starter Kit Carton - 15 mg

30 tablets
Rx only
NDC 59148-032-61

New 2-Component
Patch Design

Abilify MyCite®
(aripiprazole tablets with sensor)
30-Day Starter Kit

Dispense the accompanying Medication Guide to each patient.

Needs a compatible mobile device.
Keep Abilify MyCite® components out of the reach of children. Swallow tablets whole. Do not divide, crush or chew.

15 mg

PRINCIPAL DISPLAY PANEL - Maintenance Kit Carton - 15 mg

30 tablets
Rx only
NDC 59148-032-72

For
New 2-Component
Patch Design

Abilify MyCite®
(aripiprazole tablets with sensor)

Maintenance Kit (tablets with sensor & strips)

Dispense the accompanying Medication Guide to each patient.

Needs a compatible mobile device.
Keep Abilify MyCite® components out of the reach of children. Swallow tablets whole. Do not divide, crush or chew.

15 mg

PRINCIPAL DISPLAY PANEL - Starter Kit Carton - 20 mg

30 tablets
Rx only
NDC 59148-033-61

New 2-Component
Patch Design

Abilify MyCite®
(aripiprazole tablets with sensor)
30-Day Starter Kit

Dispense the accompanying Medication Guide to each patient.

Needs a compatible mobile device.
Keep Abilify MyCite® components out of the reach of children. Swallow tablets whole. Do not divide, crush or chew.

20 mg

PRINCIPAL DISPLAY PANEL - Maintenance Kit Carton - 20 mg

30 tablets
Rx only
NDC 59148-033-72

For
New 2-Component
Patch Design

Abilify MyCite®
(aripiprazole tablets with sensor)

Maintenance Kit (tablets with sensor & strips)

Dispense the accompanying Medication Guide to each patient.

Needs a compatible mobile device.
Keep Abilify MyCite® components out of the reach of children. Swallow tablets whole. Do not divide, crush or chew.

20 mg

PRINCIPAL DISPLAY PANEL - Starter Kit Carton - 30 mg

30 tablets
Rx only
NDC 59148-034-61

New 2-Component
Patch Design

Abilify MyCite®
(aripiprazole tablets with sensor)
30-Day Starter Kit

Dispense the accompanying Medication Guide to each patient.

Needs a compatible mobile device.
Keep Abilify MyCite® components out of the reach of children. Swallow tablets whole. Do not divide, crush or chew.

30 mg

PRINCIPAL DISPLAY PANEL - Maintenance Kit Carton - 30 mg

30 tablets
Rx only
NDC 59148-034-72

For
New 2-Component
Patch Design

Abilify MyCite®
(aripiprazole tablets with sensor)

Maintenance Kit (tablets with sensor & strips)

Dispense the accompanying Medication Guide to each patient.

Needs a compatible mobile device.
Keep Abilify MyCite® components out of the reach of children. Swallow tablets whole. Do not divide, crush or chew.

30 mg